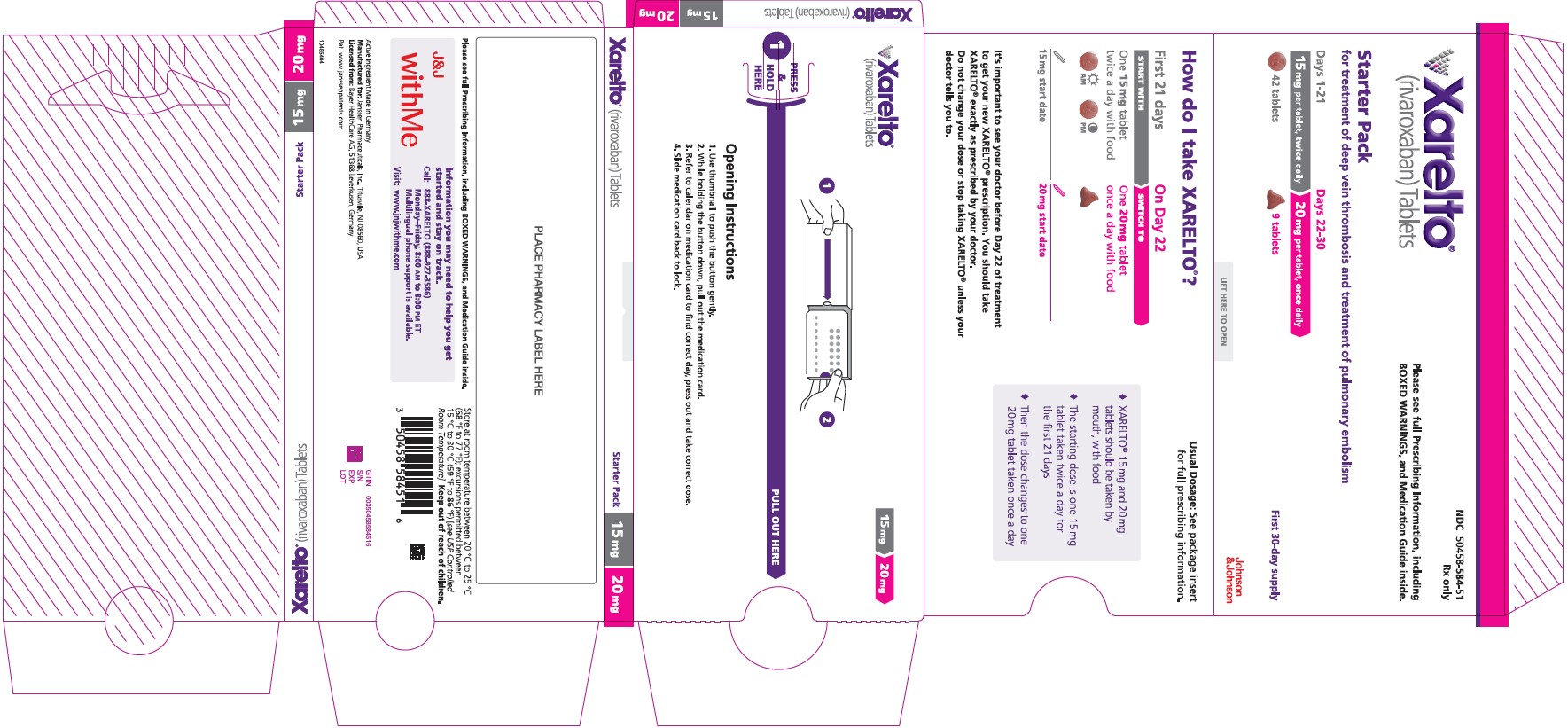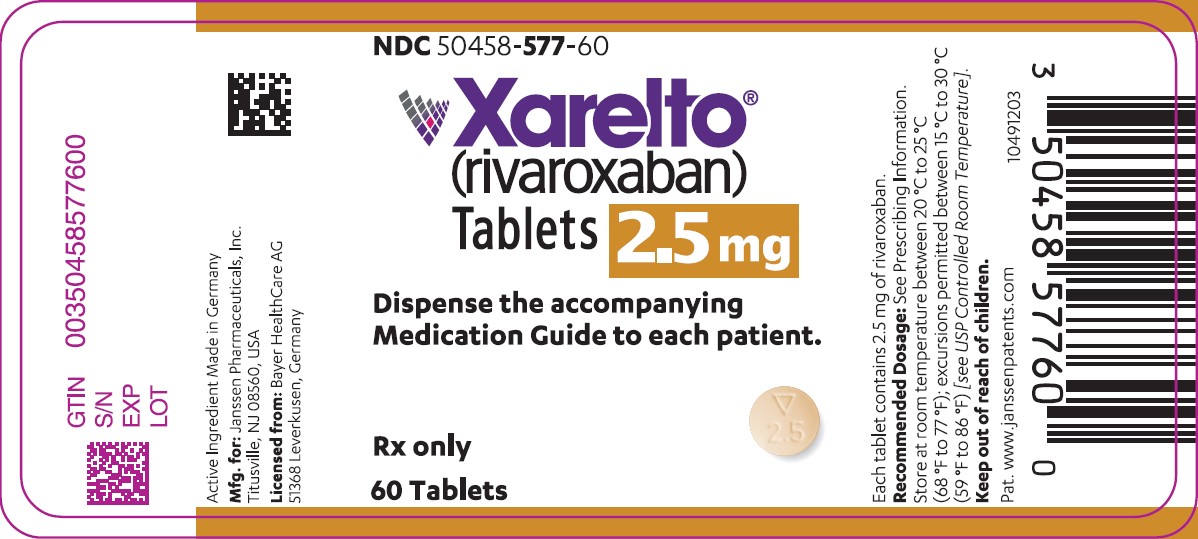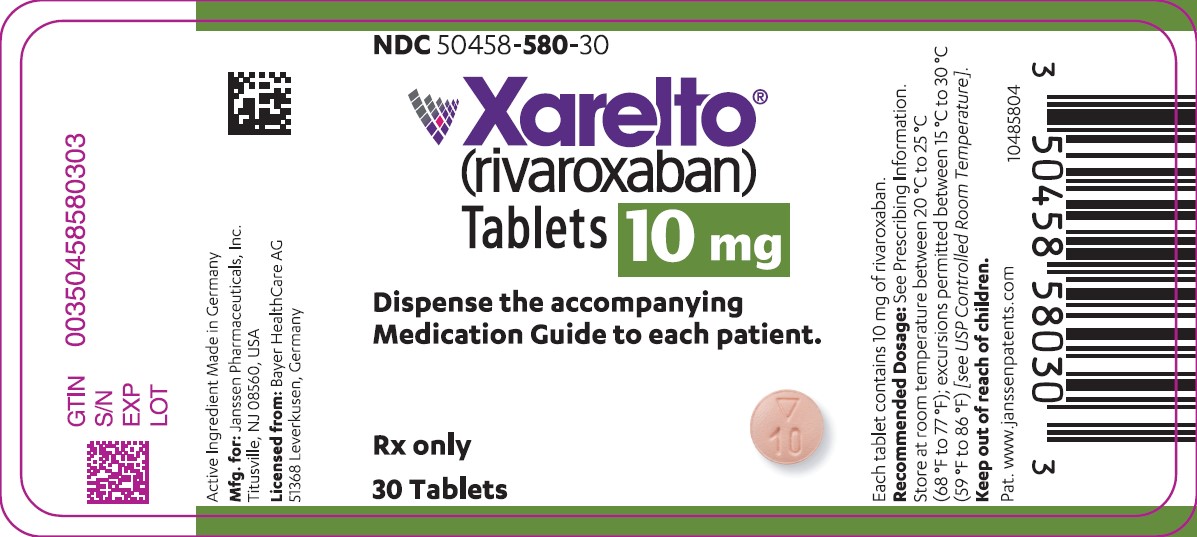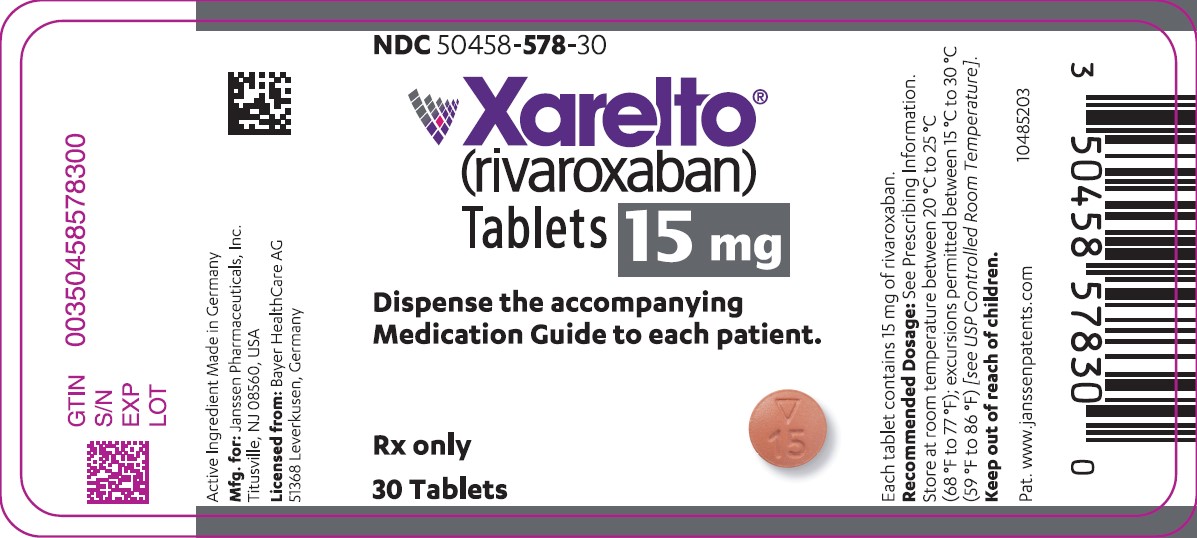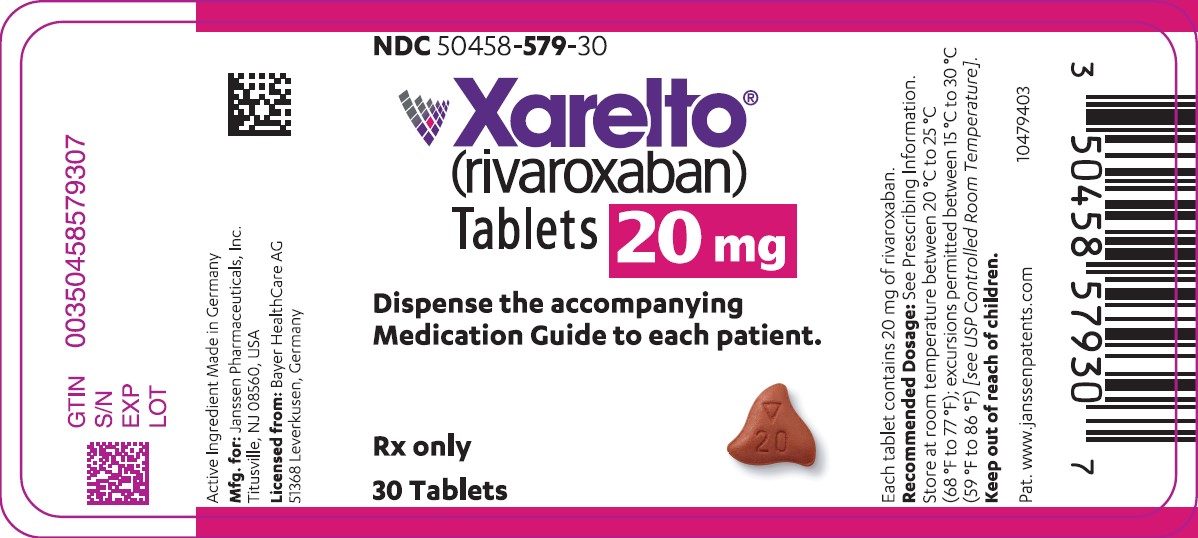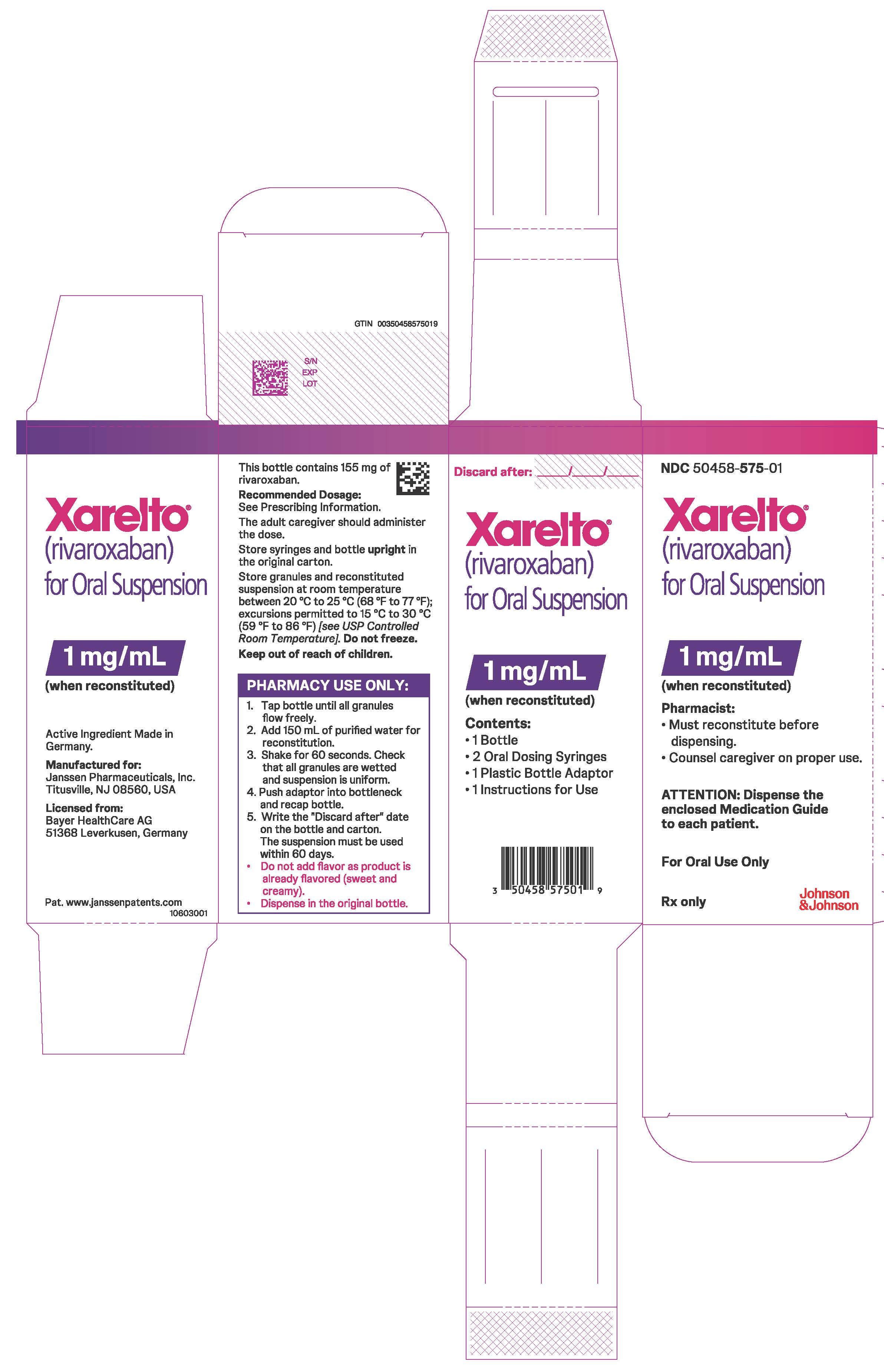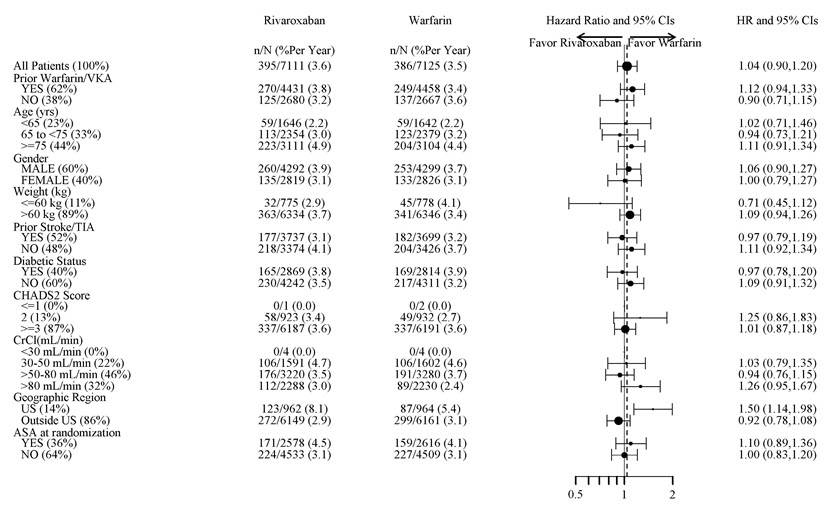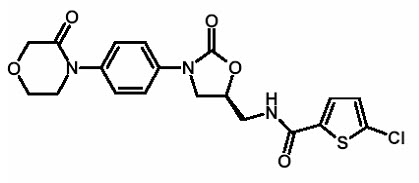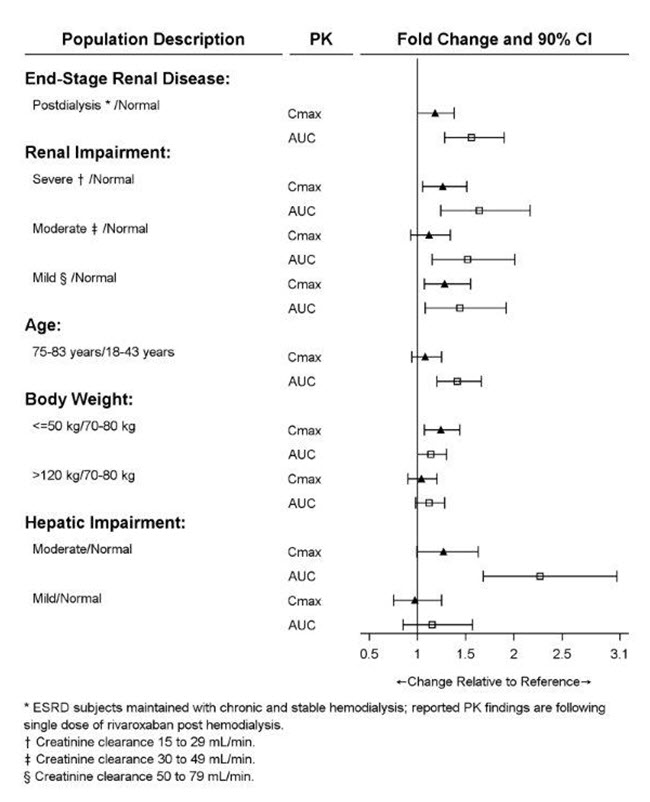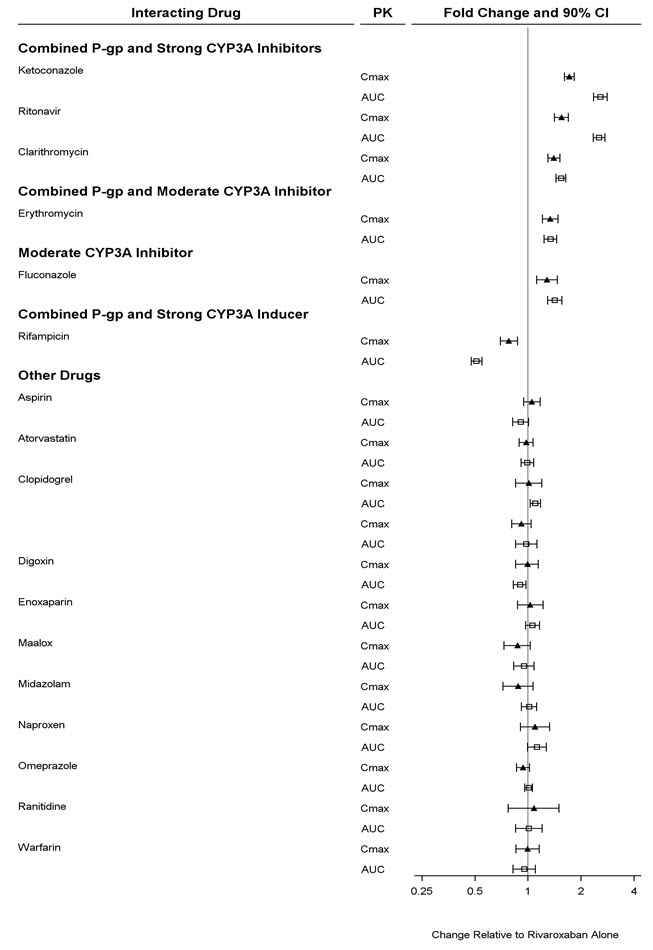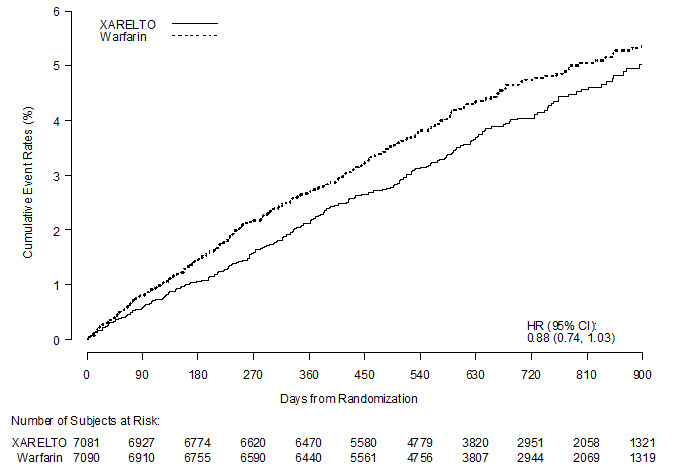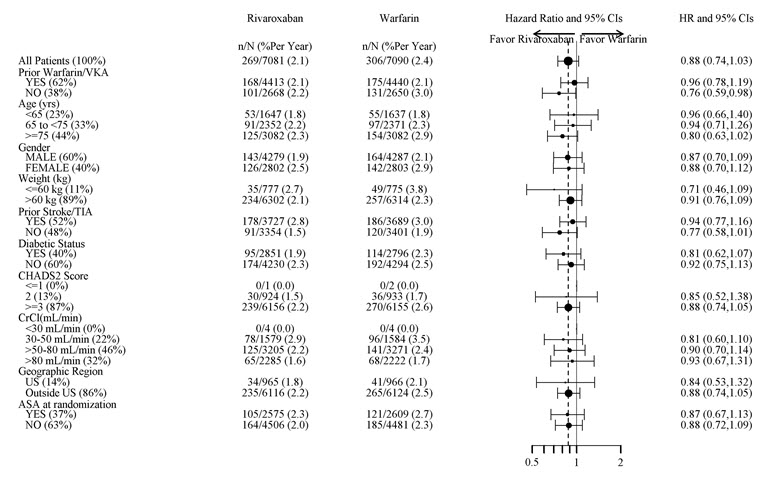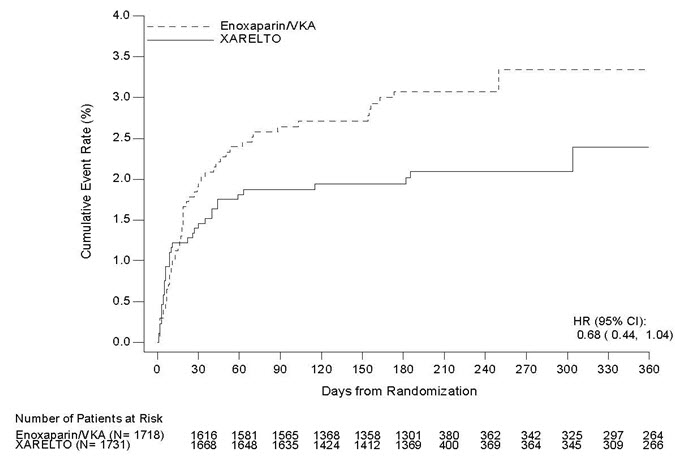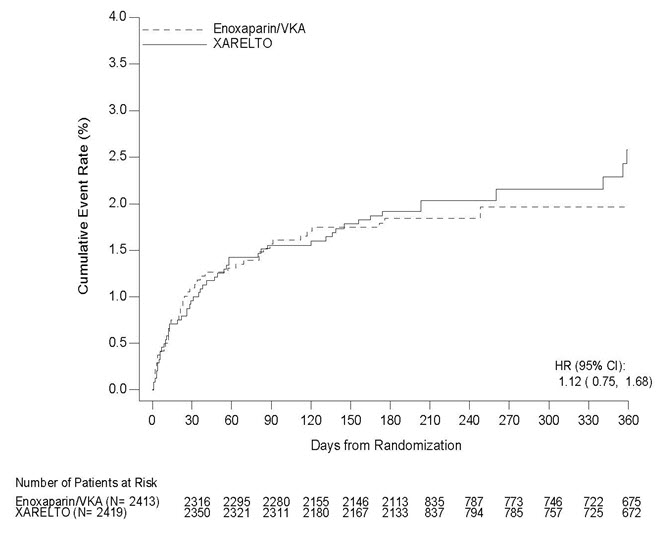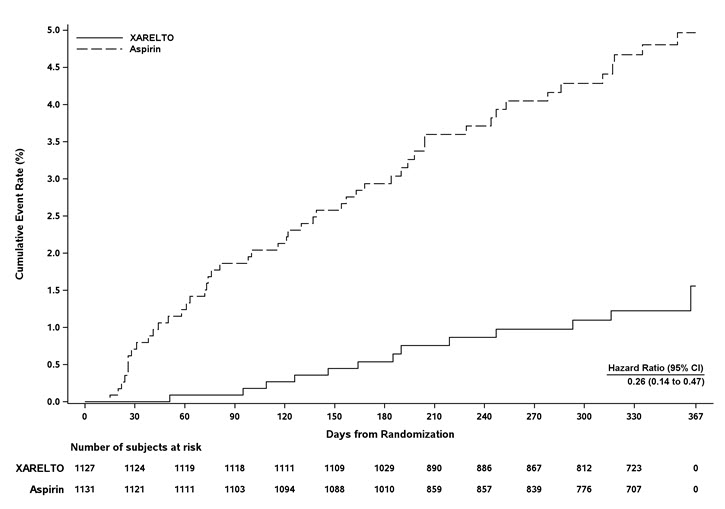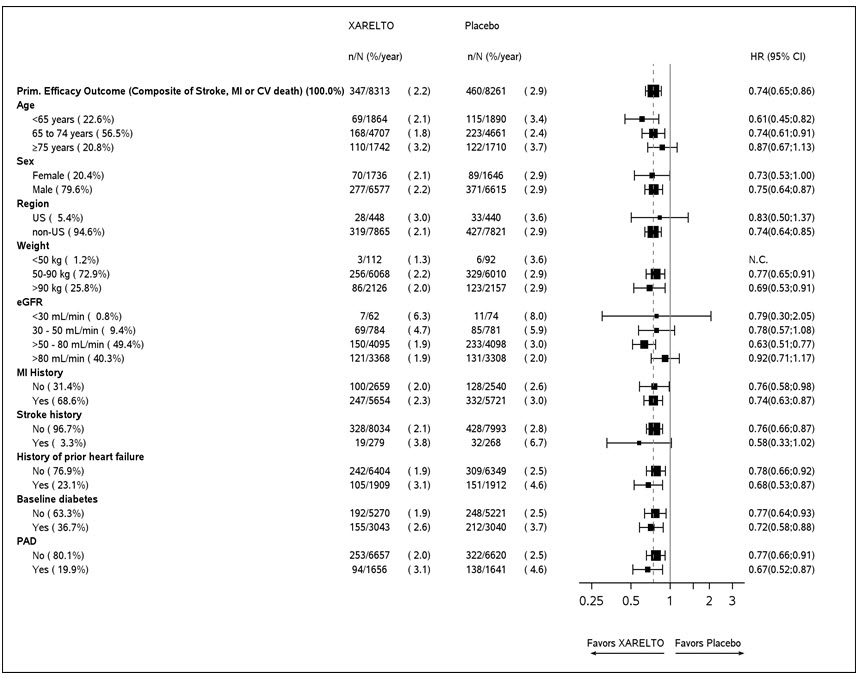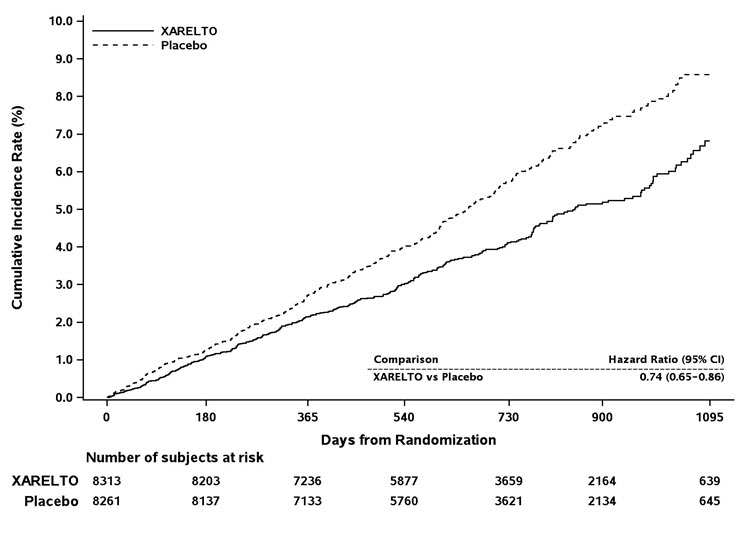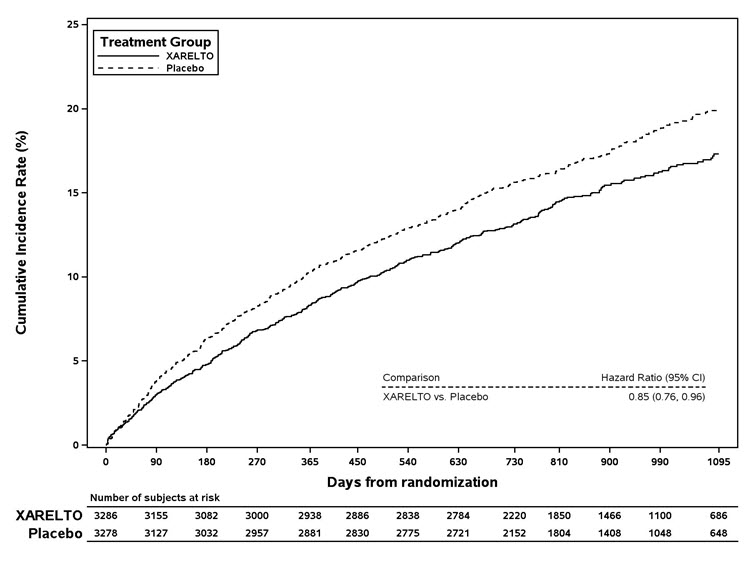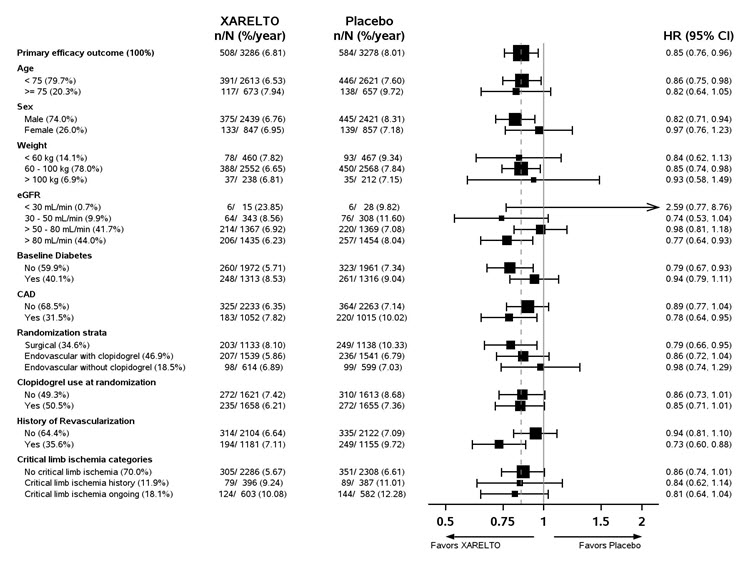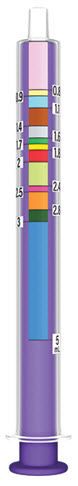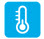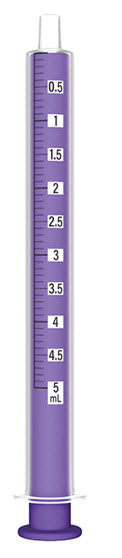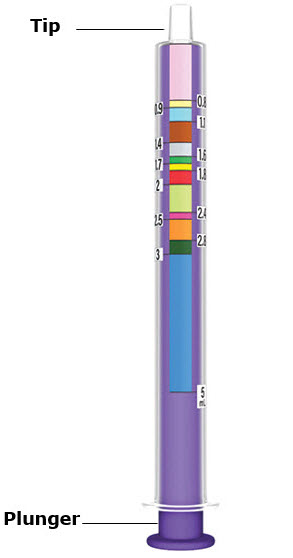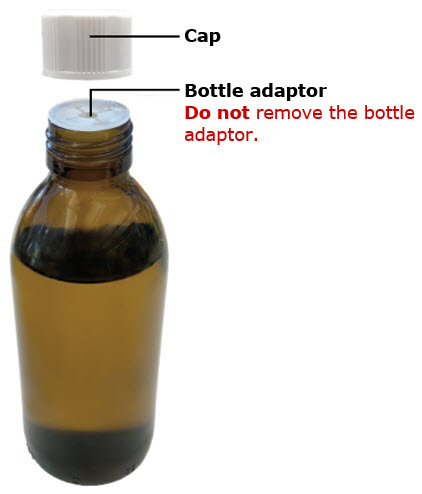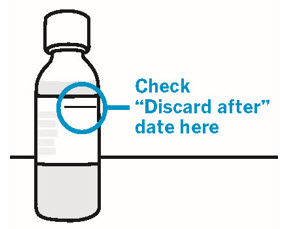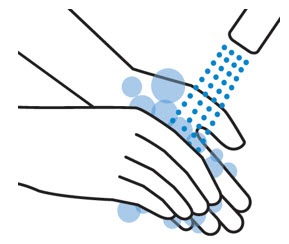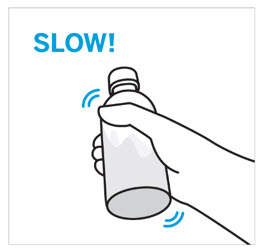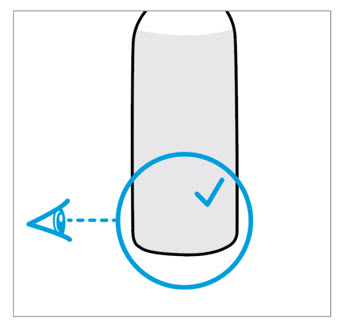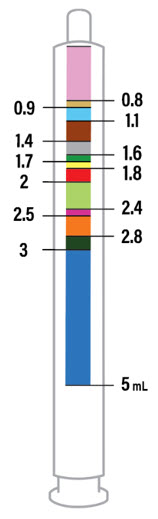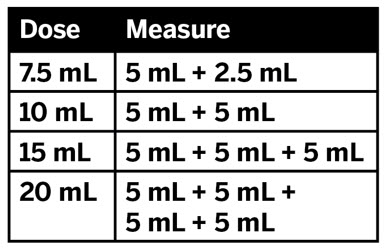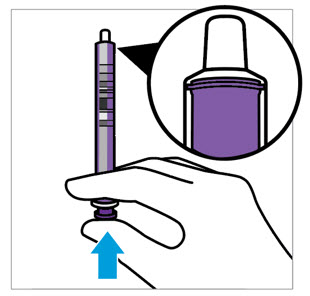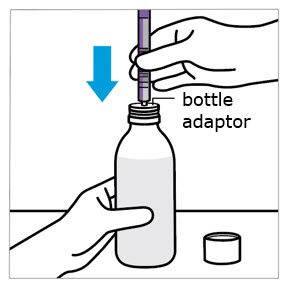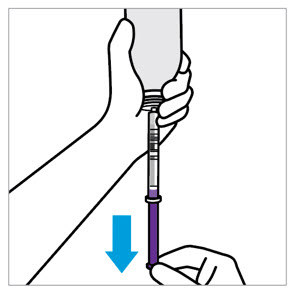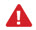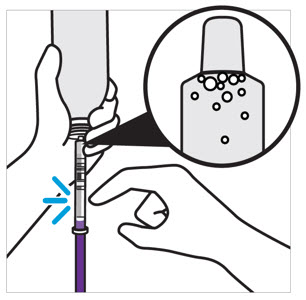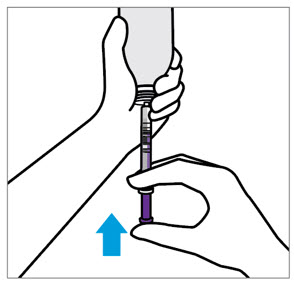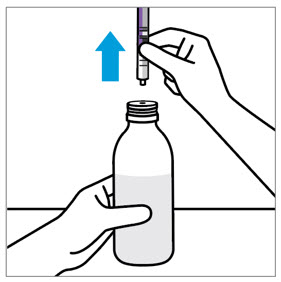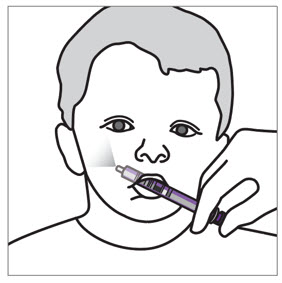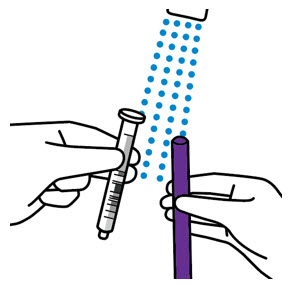 DRUG LABEL: XARELTO
NDC: 50458-577 | Form: TABLET, FILM COATED
Manufacturer: Janssen Pharmaceuticals, Inc.
Category: prescription | Type: HUMAN PRESCRIPTION DRUG LABEL
Date: 20260116

ACTIVE INGREDIENTS: RIVAROXABAN 2.5 mg/1 1
INACTIVE INGREDIENTS: HYPROMELLOSE, UNSPECIFIED; LACTOSE MONOHYDRATE; CROSCARMELLOSE SODIUM; MAGNESIUM STEARATE; MICROCRYSTALLINE CELLULOSE; SODIUM LAURYL SULFATE; FERRIC OXIDE YELLOW; POLYETHYLENE GLYCOL 3350; TITANIUM DIOXIDE

HIGHLIGHTS OF PRESCRIBING INFORMATION

These highlights do not include all the information needed to use XARELTO safely and effectively. See full prescribing information for XARELTO.
XARELTO®(rivaroxaban) tablets, for oral use
XARELTO®(rivaroxaban) for oral suspension
Initial U.S. Approval: 2011

WARNING: (A) PREMATURE DISCONTINUATION OF XARELTO INCREASES THE RISK OF THROMBOTIC EVENTS, (B) SPINAL/EPIDURAL HEMATOMA

See full prescribing information for complete boxed warning.

(A) Premature discontinuation of XARELTO increases the risk of thrombotic events

Premature discontinuation of any oral anticoagulant, including XARELTO, increases the risk of thrombotic events. To reduce this risk, consider coverage with another anticoagulant if XARELTO is discontinued for a reason other than pathological bleeding or completion of a course of therapy. (2.2, 2.3, 5.1, 14.1)

(B) Spinal/epidural hematoma

Epidural or spinal hematomas have occurred in patients treated with XARELTO who are receiving neuraxial anesthesia or undergoing spinal puncture. These hematomas may result in long-term or permanent paralysis. (5.2, 5.3, 6.2)

Monitor patients frequently for signs and symptoms of neurological impairment and if observed, treat urgently. Consider the benefits and risks before neuraxial intervention in patients who are or who need to be anticoagulated. (5.3)

RECENT MAJOR CHANGES

Warnings and Precautions (5.2) | 06/2025

1 INDICATIONS AND USAGE

XARELTO is a factor Xa inhibitor indicated:

- to reduce risk of stroke and systemic embolism in nonvalvular atrial fibrillation (1.1)
- for treatment of deep vein thrombosis (DVT) (1.2)
- for treatment of pulmonary embolism (PE) (1.3)
- for reduction in the risk of recurrence of DVT or PE (1.4)
- for the prophylaxis of DVT, which may lead to PE in patients undergoing knee or hip replacement surgery (1.5)
- for prophylaxis of venous thromboembolism (VTE) in acutely ill medical patients (1.6)
- to reduce the risk of major cardiovascular events in patients with coronary artery disease (CAD) (1.7)
- to reduce the risk of major thrombotic vascular events in patients with peripheral artery disease (PAD), including patients after recent lower extremity revascularization due to symptomatic PAD (1.8)
- for treatment of VTE and reduction in the risk of recurrent VTE in pediatric patients from birth to less than 18 years (1.9)
- for thromboprophylaxis in pediatric patients 2 years and older with congenital heart disease after the Fontan procedure (1.10)

2 DOSAGE AND ADMINISTRATION

- Nonvalvular Atrial Fibrillation: 15 or 20 mg, once daily with food (2.1)
- Treatment of DVT and/or PE: 15 mg orally twice daily with food for the first 21 days followed by 20 mg orally once daily with food for the remaining treatment (2.1)
- Reduction in the Risk of Recurrence of DVT and/or PE in patients at continued risk for DVT and/or PE: 10 mg once daily with or without food, after at least 6 months of standard anticoagulant treatment (2.1)
- Prophylaxis of DVT Following Hip or Knee Replacement Surgery: 10 mg orally once daily with or without food (2.1)
- Prophylaxis of VTE in Acutely Ill Medical Patients at Risk for Thromboembolic Complications Not at High Risk of Bleeding: 10 mg once daily, with or without food, in hospital and after hospital discharge for a total recommended duration of 31 to 39 days (2.1)
- CAD or PAD: 2.5 mg orally twice daily with or without food, in combination with aspirin (75–100 mg) once daily (2.1)
- Pediatric Patients:See dosing recommendations in the Full Prescribing Information (2.2)

3 DOSAGE FORMS AND STRENGTHS

- Tablets: 2.5 mg, 10 mg, 15 mg, and 20 mg (3)
- For oral suspension: 1 mg/mL once reconstituted (3)

4 CONTRAINDICATIONS

- Active pathological bleeding (4)
- Severe hypersensitivity reaction to XARELTO (4)

5 WARNINGS AND PRECAUTIONS

- Risk of bleeding: XARELTO can cause serious and fatal bleeding. An agent to reverse the activity of rivaroxaban is available. (5.2)
- Pregnancy-related hemorrhage: Use XARELTO with caution in pregnant women due to the potential for obstetric hemorrhage and/or emergent delivery. (5.7, 8.1)
- Prosthetic heart valves: XARELTO use not recommended. (5.8)
- Increased Risk of Thrombosis in Patients with Triple Positive Antiphospholipid Syndrome: XARELTO use not recommended. (5.10)

6 ADVERSE REACTIONS

- The most common adverse reaction (>5%) in adult patients was bleeding. (6.1)
- The most common adverse reactions (>10%) in pediatric patients were bleeding, cough, vomiting, and gastroenteritis. (6.1)

To report SUSPECTED ADVERSE REACTIONS, contact Janssen Pharmaceuticals, Inc. at 1-800-526-7736 or FDA at 1-800-FDA-1088 or www.fda.gov/medwatch.

7 DRUG INTERACTIONS

- Avoid combined P-gp and strong CYP3A inhibitors and inducers (7.2, 7.3)
- Anticoagulants: Avoid concomitant use (7.4)

8 USE IN SPECIFIC POPULATIONS

- Renal impairment: Avoid or adjust dose (8.6)
- Hepatic impairment: Avoid use in Child-Pugh B and C hepatic impairment or hepatic disease associated with coagulopathy (8.7)

FULL PRESCRIBING INFORMATION

WARNING: (A) PREMATURE DISCONTINUATION OF XARELTO INCREASES THE RISK OF THROMBOTIC EVENTS, (B) SPINAL/EPIDURAL HEMATOMA

A. Premature discontinuation of XARELTO increases the risk of thrombotic events

Premature discontinuation of any oral anticoagulant, including XARELTO, increases the risk of thrombotic events. If anticoagulation with XARELTO is discontinued for a reason other than pathological bleeding or completion of a course of therapy, consider coverage with another anticoagulant [see Dosage and Administration (2.3, 2.4), Warnings and Precautions (5.1), and Clinical Studies (14.1)] .

B. Spinal/epidural hematoma

Epidural or spinal hematomas have occurred in patients treated with XARELTO who are receiving neuraxial anesthesia or undergoing spinal puncture. These hematomas may result in long-term or permanent paralysis. Consider these risks when scheduling patients for spinal procedures. Factors that can increase the risk of developing epidural or spinal hematomas in these patients include:

- use of indwelling epidural catheters
- concomitant use of other drugs that affect hemostasis, such as non-steroidal anti-inflammatory drugs (NSAIDs), platelet inhibitors, other anticoagulants
- a history of traumatic or repeated epidural or spinal punctures
- a history of spinal deformity or spinal surgery
- optimal timing between the administration of XARELTO and neuraxial procedures is not known

[see Warnings and Precautions (5.2, 5.3)and Adverse Reactions (6.2)].

Monitor patients frequently for signs and symptoms of neurological impairment. If neurological compromise is noted, urgent treatment is necessary [see Warnings and Precautions (5.3)] .

Consider the benefits and risks before neuraxial intervention in patients anticoagulated or to be anticoagulated for thromboprophylaxis [see Warnings and Precautions (5.3)] .

1 INDICATIONS AND USAGE

1.1 Reduction of Risk of Stroke and Systemic Embolism in Nonvalvular Atrial Fibrillation

XARELTO is indicated to reduce the risk of stroke and systemic embolism in adult patients with nonvalvular atrial fibrillation.

There are limited data on the relative effectiveness of XARELTO and warfarin in reducing the risk of stroke and systemic embolism when warfarin therapy is well-controlled [see Clinical Studies (14.1)].

1.2 Treatment of Deep Vein Thrombosis

XARELTO is indicated for the treatment of deep vein thrombosis (DVT).

1.3 Treatment of Pulmonary Embolism

XARELTO is indicated for the treatment of pulmonary embolism (PE).

1.4 Reduction in the Risk of Recurrence of Deep Vein Thrombosis and/or Pulmonary Embolism

XARELTO is indicated for the reduction in the risk of recurrence of DVT and/or PE in adult patients at continued risk for recurrent DVT and/or PE after completion of initial treatment lasting at least 6 months.

1.5 Prophylaxis of Deep Vein Thrombosis Following Hip or Knee Replacement Surgery

XARELTO is indicated for the prophylaxis of DVT, which may lead to PE in adult patients undergoing knee or hip replacement surgery.

1.6 Prophylaxis of Venous Thromboembolism in Acutely Ill Medical Patients at Risk for Thromboembolic Complications Not at High Risk of Bleeding

XARELTO is indicated for the prophylaxis of venous thromboembolism (VTE) and VTE related death during hospitalization and post hospital discharge in adult patients admitted for an acute medical illness who are at risk for thromboembolic complications due to moderate or severe restricted mobility and other risk factors for VTE and not at high risk of bleeding [see Warnings and Precautions (5.2)and Clinical Studies (14.5)] .

1.7 Reduction of Risk of Major Cardiovascular Events in Patients with Coronary Artery Disease (CAD)

XARELTO, in combination with aspirin, is indicated to reduce the risk of major cardiovascular events (cardiovascular death, myocardial infarction, and stroke) in adult patients with coronary artery disease.

1.8 Reduction of Risk of Major Thrombotic Vascular Events in Patients with Peripheral Artery Disease (PAD), Including Patients after Lower Extremity Revascularization due to Symptomatic PAD

XARELTO, in combination with aspirin, is indicated to reduce the risk of major thrombotic vascular events (myocardial infarction, ischemic stroke, acute limb ischemia, and major amputation of a vascular etiology) in adult patients with PAD, including patients who have recently undergone a lower extremity revascularization procedure due to symptomatic PAD.

1.9 Treatment of Venous Thromboembolism and Reduction in Risk of Recurrent Venous Thromboembolism in Pediatric Patients

XARELTO is indicated for the treatment of venous thromboembolism (VTE) and the reduction in the risk of recurrent VTE in pediatric patients from birth to less than 18 years after at least 5 days of initial parenteral anticoagulant treatment.

1.10 Thromboprophylaxis in Pediatric Patients with Congenital Heart Disease after the Fontan Procedure

XARELTO is indicated for thromboprophylaxis in pediatric patients aged 2 years and older with congenital heart disease who have undergone the Fontan procedure.

2 DOSAGE AND ADMINISTRATION

2.1 Recommended Dosage in Adults

Table 1: Recommended Dosage in Adults
Indication | Renal Considerations [Calculate CrCl based on actual weight. [See Warnings and Precautions (5.4) and Use in Specific Populations (8.6)]] | Dosage | Food/Timing [See Clinical Pharmacology (12.3)]
Reduction in Risk of Stroke in Nonvalvular Atrial Fibrillation | CrCl >50 mL/min | 20 mg once daily | Take with evening meal
Reduction in Risk of Stroke in Nonvalvular Atrial Fibrillation | CrCl ≤50 mL/min [Patients with CrCl <30 mL/min were not studied, but administration of XARELTO is expected to result in serum concentrations of rivaroxaban similar to those in patients with moderate renal impairment (CrCl 30 to <50 mL/min) [see Use in Specific Populations (8.6)]] | 15 mg once daily | Take with evening meal
Treatment of DVT and/or PE | CrCl ≥15 mL/min | 15 mg twice daily ▼ after 21 days, transition to ▼ 20 mg once daily | Take with food, at the same time each day
Treatment of DVT and/or PE | CrCl <15 mL/min | Avoid Use
Reduction in the Risk of Recurrence of DVT and/or PE in patients at continued risk for DVT and/or PE | CrCl ≥15 mL/min | 10 mg once daily, after at least 6 months of standard anticoagulant treatment | Take with or without food
Reduction in the Risk of Recurrence of DVT and/or PE in patients at continued risk for DVT and/or PE | CrCl <15 mL/min | Avoid Use
Prophylaxis of DVT Following:
- Hip Replacement Surgery [See Dosage and Administration (2.4)] | CrCl ≥15 mL/min | 10 mg once daily for 35 days, 6–10 hours after surgery once hemostasis has been established | Take with or without food
- Hip Replacement Surgery [See Dosage and Administration (2.4)] | CrCl <15 mL/min | Avoid Use
- Knee Replacement Surgery | CrCl ≥15 mL/min | 10 mg once daily for 12 days, 6–10 hours after surgery once hemostasis has been established | Take with or without food
- Knee Replacement Surgery | CrCl <15 mL/min | Avoid Use
Prophylaxis of VTE in Acutely Ill Medical Patients at Risk for Thromboembolic Complications Not at High Risk of Bleeding | CrCl ≥15 mL/min | 10 mg once daily, in hospital and after hospital discharge, for a total recommended duration of 31 to 39 days | Take with or without food
Prophylaxis of VTE in Acutely Ill Medical Patients at Risk for Thromboembolic Complications Not at High Risk of Bleeding | CrCl <15 mL/min | Avoid Use
Reduction of Risk of Major Cardiovascular Events (CV Death, MI, and Stroke) in CAD | No dose adjustment needed based on CrCl | 2.5 mg twice daily, plus aspirin (75–100 mg) once daily | Take with or without food
Reduction of Risk of Major Thrombotic Vascular Events in PAD, Including Patients after Lower Extremity Revascularization due to Symptomatic PAD | No dose adjustment needed based on CrCl | 2.5 mg twice daily, plus aspirin (75–100 mg) once daily. When starting therapy after a successful lower extremity revascularization procedure, initiate once hemostasis has been established. | Take with or without food

2.2 Recommended Dosage in Pediatric Patients

Treatment of Venous Thromboembolism and Reduction in Risk of Recurrent Venous Thromboembolism in Pediatric Patients

Table 2: Recommended Dosage in Pediatric Patients Birth to Less than 18 Years for Treatment of and Reduction in Risk of Recurrent VTE [Initiate XARELTO treatment following at least 5 days of initial parenteral anticoagulation therapy.] , [Patients <6 months of age should meet the following criteria: at birth were at least 37 weeks of gestation, have had at least 10 days of oral feeding, and weigh ≥2.6 kg at the time of dosing.]
Dosage Form | Body Weight | 1 mg XARELTO = 1 mL Suspension
Dosage Form | Body Weight | Dosage |  |  | Total Daily Dose [All doses should be taken with feeding or with food since exposures match that of 20 mg daily dose in adults.]
Dosage Form | Body Weight | Once a Day [Once a day: approximately 24 hours apart; 2 times a day: approximately 12 hours apart; 3 times a day: approximately 8 hours apart] | 2 Times a Day | 3 Times a Day
Oral Suspension Only | 2.6 kg to 2.9 kg |  |  | 0.8 mg | 2.4 mg
Oral Suspension Only | 3 kg to 3.9 kg |  |  | 0.9 mg | 2.7 mg
Oral Suspension Only | 4 kg to 4.9 kg |  |  | 1.4 mg | 4.2 mg
Oral Suspension Only | 5 kg to 6.9 kg |  |  | 1.6 mg | 4.8 mg
Oral Suspension Only | 7 kg to 7.9 kg |  |  | 1.8 mg | 5.4 mg
Oral Suspension Only | 8 kg to 8.9 kg |  |  | 2.4 mg | 7.2 mg
Oral Suspension Only | 9 kg to 9.9 kg |  |  | 2.8 mg | 8.4 mg
Oral Suspension Only | 10 kg to 11.9 kg |  |  | 3 mg | 9 mg
Oral Suspension Only | 12 kg to 29.9 kg |  | 5 mg |  | 10 mg
Oral Suspension or Tablets | 30 kg to 49.9 kg | 15 mg |  |  | 15 mg
Oral Suspension or Tablets | ≥50 kg | 20 mg |  |  | 20 mg

Dosing of XARELTO was not studied and therefore dosing cannot be reliably determined in the following patient populations. Its use is therefore not recommended in children less than 6 months of age with any of the following:

- Less than 37 weeks of gestation at birth
- Less than 10 days of oral feeding
- Body weight of less than 2.6 kg.

To increase absorption, all doses should be taken with feeding or with food.

Monitor the child's weight and review the dose regularly, especially for children below 12 kg. This is to ensure a therapeutic dose is maintained.

All pediatric patients (except <2 years old with catheter-related thrombosis):Therapy with XARELTO should be continued for at least 3 months in children with thrombosis. Treatment can be extended up to 12 months when clinically necessary. The benefit of continued therapy beyond 3 months should be assessed on an individual basis taking into account the risk for recurrent thrombosis versus the potential risk of bleeding.

Pediatric patients <2 years old with catheter-related thrombosis:Therapy with XARELTO should be continued for at least 1 month in children less than 2 years old with catheter-related thrombosis. Treatment can be extended up to 3 months when clinically necessary. The benefit of continued therapy beyond 1 month should be assessed on an individual basis taking into account the risk for recurrent thrombosis versus the potential risk of bleeding.

Thromboprophylaxis in Pediatric Patients with Congenital Heart Disease after the Fontan Procedure

Table 3: Recommended Dosage for Thromboprophylaxis in Pediatric Patients with Congenital Heart Disease
Dosage Form | Body Weight | 1 mg XARELTO = 1 mL Suspension
Dosage Form | Body Weight | Dosage |  | Total Daily Dose [All doses can be taken with or without food since exposures match that of 10 mg daily dose in adults.]
Dosage Form | Body Weight | Once a Day [Once a day: approximately 24 hours apart; 2 times a day: approximately 12 hours apart.] | 2 Times a Day
Oral Suspension Only | 7 kg to 7.9 kg |  | 1.1 mg | 2.2 mg
Oral Suspension Only | 8 kg to 9.9 kg |  | 1.6 mg | 3.2 mg
Oral Suspension Only | 10 kg to 11.9 kg |  | 1.7 mg | 3.4 mg
Oral Suspension Only | 12 kg to 19.9 kg |  | 2 mg | 4 mg
Oral Suspension Only | 20 kg to 29.9 kg |  | 2.5 mg | 5 mg
Oral Suspension Only | 30 kg to 49.9 kg | 7.5 mg |  | 7.5 mg
Oral Suspension or Tablets | ≥50 kg | 10 mg |  | 10 mg

Administration in Pediatric Patients

Food Effect:

For the treatment of VTE in children, the dose should be taken with food to increase absorption.

For thromboprophylaxis after Fontan procedure, the dose can be taken with or without food.

Vomit or Spit up:If the patient vomits or spits up the dose within 30 minutes after receiving the dose, a new dose should be given. However, if the patient vomits more than 30 minutes after the dose is taken, the dose should not be re-administered and the next dose should be taken as scheduled. If the patient vomits or spits up the dose repeatedly, the caregiver should contact the child's doctor right away.

Tablets:XARELTO tablet must not be split in an attempt to provide a fraction of a tablet dose.

For children unable to swallow 10, 15, or 20 mg whole tablets, XARELTO oral suspension should be used. XARELTO 2.5 mg tablets are not recommended for use in pediatric patients [see Use in Specific Populations (8.4)] .

Use in Renal Impairment in Pediatric Patients

Patients 1 Year of Age or Older

- Mild renal impairment (eGFR: 50 to ≤ 80 mL/min/1.73 m^2): No dose adjustment is required.
- Moderate or severe renal impairment (eGFR: <50 mL/min/1.73 m^2): avoid use, as limited clinical data are available.

Estimated glomerular filtration rate (eGFR) can be done using the updated Schwartz formula, eGFR (Schwartz) = (0.413 × height in cm)/serum creatinine in mg/dL, if serum creatinine (SCr) is measured by an enzymatic creatinine method that has been calibrated to be traceable to isotope dilution mass spectrometry (IDMS).

If SCr is measured with routine methods that have not been recalibrated to be traceable to IDMS (e.g., the traditional Jaffé reaction), the eGFR should be obtained from the original Schwartz formula: eGFR (mL/min/1.73 m^2) = k * height (cm)/SCr (mg/dL), where k is proportionality constant:

- k = 0.55 in children 1 year to 13 years
- k = 0.55 in girls > 13 and < 18 years
- k = 0.70 in boys > 13 and < 18 years

Patients Less than 1 Year of Age

Determine renal function using serum creatinine. Avoid use of XARELTO in pediatric patients younger than 1 year with serum creatinine results above 97.5thpercentile, as no clinical data are available.

Table 4: Reference Values of Serum Creatinine in Pediatric Patients <1 Year of Age
Age | 97.5thPercentile of Creatinine (mg/dL) | 97.5thPercentile of Creatinine (µmol/L)
Week 2 | 0.52 | 46
Week 3 | 0.46 | 41
Week 4 | 0.42 | 37
Month 2 | 0.37 | 33
Month 3 | 0.34 | 30
Month 4–6 | 0.34 | 30
Month 7–9 | 0.34 | 30
Month 10–12 | 0.36 | 32

2.3 Switching to and from XARELTO

Switching from Warfarin to XARELTO- When switching patients from warfarin to XARELTO, discontinue warfarin and start XARELTO as soon as the International Normalized Ratio (INR) is below 3.0 in adults and below 2.5 in pediatric patients to avoid periods of inadequate anticoagulation.

Switching from XARELTO to Warfarin –

- Adults:

No clinical trial data are available to guide converting patients from XARELTO to warfarin. XARELTO affects INR, so INR measurements made during coadministration with warfarin may not be useful for determining the appropriate dose of warfarin. One approach is to discontinue XARELTO and begin both a parenteral anticoagulant and warfarin at the time the next dose of XARELTO would have been taken.

- Pediatric Patients:

To ensure adequate anticoagulation during the transition from XARELTO to warfarin, continue XARELTO for at least 2 days after the first dose of warfarin. After 2 days of co-administration, an INR should be obtained prior to the next scheduled dose of XARELTO. Co-administration of XARELTO and warfarin is advised to continue until the INR is ≥ 2.0.

Once XARELTO is discontinued, INR testing may be done reliably 24 hours after the last dose.

Switching from XARELTO to Anticoagulants other than Warfarin- For adult and pediatric patients currently taking XARELTO and transitioning to an anticoagulant with rapid onset, discontinue XARELTO and give the first dose of the other anticoagulant (oral or parenteral) at the time that the next XARELTO dose would have been taken [see Drug Interactions (7.4)] .

Switching from Anticoagulants other than Warfarin to XARELTO -For adult and pediatric patients currently receiving an anticoagulant other than warfarin, start XARELTO 0 to 2 hours prior to the next scheduled administration of the drug (e.g., low molecular weight heparin or non-warfarin oral anticoagulant) and omit administration of the other anticoagulant. For unfractionated heparin being administered by continuous infusion, stop the infusion and start XARELTO at the same time.

2.4 Discontinuation for Surgery and other Interventions

If anticoagulation must be discontinued to reduce the risk of bleeding with surgical or other procedures, XARELTO should be stopped at least 24 hours before the procedure to reduce the risk of bleeding [see Warnings and Precautions (5.2)] . In deciding whether a procedure should be delayed until 24 hours after the last dose of XARELTO, the increased risk of bleeding should be weighed against the urgency of intervention. XARELTO should be restarted after the surgical or other procedures as soon as adequate hemostasis has been established, noting that the time to onset of therapeutic effect is short [see Warnings and Precautions (5.1)] . If oral medication cannot be taken during or after surgical intervention, consider administering a parenteral anticoagulant.

2.5 Missed Dose

Adults

- For patients receiving 2.5 mg twice daily: if a dose is missed, the patient should take a single 2.5 mg XARELTO dose as recommended at the next scheduled time.
- For patients receiving 15 mg twice daily: The patient should take XARELTO immediately to ensure intake of 30 mg XARELTO per day. Two 15 mg tablets may be taken at once.
- For patients receiving 20 mg, 15 mg or 10 mg once daily: The patient should take the missed XARELTO dose immediately. The dose should not be doubled within the same day to make up for a missed dose.

Pediatric Patients

- If XARELTO is taken once a day, the patient should take the missed dose as soon as possible once it is noticed, but only on the same day. If this is not possible, the patient should skip the dose and continue with the next dose as prescribed. The patient should not take two doses to make up for a missed dose.
- If XARELTO is taken two times a day, the patient should take the missed morning dose as soon as possible once it is noticed. A missed morning dose may be taken together with the evening dose. A missed evening dose can only be taken in the same evening.
- If XARELTO is taken three times a day, if a dose is missed, the patient should skip the missed dose and go back to the regular dosing schedule at the usual time without compensating for the missed dose.

On the following day, the patient should continue with their regular regimen.

2.6 Administration Options

For adult patients who are unable to swallow whole tablets, XARELTO tablets (all strengths) may be crushed and mixed with applesauce immediately prior to use and administered orally. After the administration of a crushed XARELTO 15 mg or 20 mg tablet, the dose should be immediately followed by food. Administration with food is not required for the 2.5 mg or 10 mg tablets [see Clinical Pharmacology (12.3)] .

Administrationof XARELTO tablets via nasogastric (NG) tube or gastric feeding tube:After confirming gastric placement of the tube, XARELTO tablets (all strengths) may be crushed and suspended in 50 mL of water and administered via an NG tube or gastric feeding tube. Since rivaroxaban absorption is dependent on the site of drug release, avoid administration of XARELTO distal to the stomach which can result in reduced absorption and thereby, reduced drug exposure. After the administration of a crushed XARELTO 15 mg or 20 mg tablet, the dose should then be immediately followed by enteral feeding. Enteral feeding is not required following administration of the 2.5 mg or 10 mg tablets [see Clinical Pharmacology (12.3)] .

Crushed XARELTO tablets (all strengths) are stable in water and in applesauce for up to 4 hours. An in vitrocompatibility study indicated that there is no adsorption of rivaroxaban from a water suspension of a crushed XARELTO tablet to PVC or silicone nasogastric (NG) tubing.

Administration of XARELTO suspension via NG tube or gastric feeding tube: XARELTO oral suspension may be given through NG or gastric feeding tube. After the administration, flush the feeding tube with water.

For the treatment or reduction in risk of recurrent VTE in pediatric patients, the dose should then be immediately followed by enteral feeding to increase absorption. For the thromboprophylaxis in pediatric patients with congenital heart disease who have undergone the Fontan procedure, the dose does not require to be followed by enteral feeding.

An in vitrocompatibility study indicated that XARELTO suspension can be used with PVC, polyurethane or silicone NG tubing.

2.7 Preparation Instructions for Pharmacy of XARELTO for Oral Suspension

Do not add flavor as product is already flavored (sweet and creamy).

Reconstitute before dispensing:

- Tap the bottle until all granules flow freely.
- Add 150 mL of purified water for reconstitution.
- Shake for 60 seconds. Check that all granules are wetted and the suspension is uniform.
- Push the adaptor into bottleneck and recap bottle.
- The suspension must be used within 60 days.
- Write the "Discard after" date on the bottle and carton.

Dispensing Instructions:

- Dispense in the original bottle.
- Dispense the bottle upright with the syringes provided in the original carton.

Store reconstituted suspension at room temperature between 20 °C to 25 °C (68 °F to 77 °F); excursions permitted between 15 °C to 30 °C (59 °F to 86 °F). Do not freeze.

It is recommended the pharmacist counsel the caregiver on proper use. Alert the patient or caregiver to read the Medication Guide and Instructions for Use.

3 DOSAGE FORMS AND STRENGTHS

- 2.5 mg tablets: Round, light yellow, and film-coated with a triangle pointing down above a "2.5" marked on one side and "Xa" on the other side
- 10 mg tablets: Round, light red, biconvex and film-coated with a triangle pointing down above a "10" marked on one side and "Xa" on the other side
- 15 mg tablets: Round, red, biconvex, and film-coated with a triangle pointing down above a "15" marked on one side and "Xa" on the other side
- 20 mg tablets: Triangle-shaped, dark red, and film-coated with a triangle pointing down above a "20" marked on one side and "Xa" on the other side
- For oral suspension: white to off-white granules; once reconstituted, provide flavored white to off-white opaque liquid with a concentration of 1 mg/mL.

4 CONTRAINDICATIONS

XARELTO is contraindicated in patients with:

- active pathological bleeding [see Warnings and Precautions (5.2)]
- severe hypersensitivity reaction to XARELTO (e.g., anaphylactic reactions) [see Adverse Reactions (6.2)]

5 WARNINGS AND PRECAUTIONS

5.1 Increased Risk of Thrombotic Events after Premature Discontinuation

Premature discontinuation of any oral anticoagulant, including XARELTO, in the absence of adequate alternative anticoagulation increases the risk of thrombotic events. An increased rate of stroke was observed during the transition from XARELTO to warfarin in clinical trials in atrial fibrillation patients. If XARELTO is discontinued for a reason other than pathological bleeding or completion of a course of therapy, consider coverage with another anticoagulant [see Dosage and Administration (2.3, 2.4)and Clinical Studies (14.1)] .

5.2 Risk of Bleeding

XARELTO increases the risk of bleeding, including in any organ, and can cause serious or fatal bleeding. In deciding whether to prescribe XARELTO to patients at increased risk of bleeding, the risk of thrombotic events should be weighed against the risk of bleeding.

Promptly evaluate any signs or symptoms of blood loss and consider the need for blood replacement. Discontinue XARELTO in patients with active pathological hemorrhage. The terminal elimination half-life of rivaroxaban is 5 to 9 hours in healthy subjects aged 20 to 45 years.

Concomitant use of other drugs that impair hemostasis increases the risk of bleeding. These include aspirin, P2Y12platelet inhibitors, dual antiplatelet therapy, other antithrombotic agents, fibrinolytic therapy, non-steroidal anti-inflammatory drugs (NSAIDs) [see Drug Interactions (7.4)] , selective serotonin reuptake inhibitors, and serotonin norepinephrine reuptake inhibitors.

Concomitant use of drugs that are known combined P-gp and strong CYP3A inhibitors increases rivaroxaban exposure and may increase bleeding risk [see Drug Interactions (7.2)] .

Risk of Hemorrhage in Acutely Ill Medical Patients at High Risk of Bleeding

Acutely ill medical patients with the following conditions are at increased risk of bleeding with the use of XARELTO for primary VTE prophylaxis: history of bronchiectasis, pulmonary cavitation, or pulmonary hemorrhage, active cancer (i.e., undergoing acute, in-hospital cancer treatment), active gastroduodenal ulcer in the three months prior to treatment, history of bleeding in the three months prior to treatment, or dual antiplatelet therapy. XARELTO is not for use for primary VTE prophylaxis in these hospitalized, acutely ill medical patients at high risk of bleeding.

Reversal of Anticoagulant Effect

An agent to reverse the anti-factor Xa activity of rivaroxaban is available. Because of high plasma protein binding, rivaroxaban is not dialyzable [see Clinical Pharmacology (12.3)] . Protamine sulfate and vitamin K are not expected to affect the anticoagulant activity of rivaroxaban. Use of procoagulant reversal agents, such as prothrombin complex concentrate (PCC), activated prothrombin complex concentrate or recombinant factor VIIa, may be considered but has not been evaluated in clinical efficacy and safety studies. Monitoring for the anticoagulation effect of rivaroxaban using a clotting test (PT, INR or aPTT) or anti-factor Xa (FXa) activity is not recommended.

5.3 Spinal/Epidural Anesthesia or Puncture

When neuraxial anesthesia (spinal/epidural anesthesia) or spinal puncture is employed, patients treated with anticoagulant agents for prevention of thromboembolic complications are at risk of developing an epidural or spinal hematoma which can result in long-term or permanent paralysis [see Boxed Warning] .

To reduce the potential risk of bleeding associated with the concurrent use of XARELTO and epidural or spinal anesthesia/analgesia or spinal puncture, consider the pharmacokinetic profile of XARELTO [see Clinical Pharmacology (12.3)] . Placement or removal of an epidural catheter or lumbar puncture is best performed when the anticoagulant effect of XARELTO is low; however, the exact timing to reach a sufficiently low anticoagulant effect in each patient is not known.

An indwelling epidural or intrathecal catheter should not be removed before at least 2 half-lives have elapsed (i.e., 18 hours in young patients aged 20 to 45 years and 26 hours in elderly patients aged 60 to 76 years), after the last administration of XARELTO [see Clinical Pharmacology (12.3)] . The next XARELTO dose should not be administered earlier than 6 hours after the removal of the catheter. If traumatic puncture occurs, delay the administration of XARELTO for 24 hours.

Should the physician decide to administer anticoagulation in the context of epidural or spinal anesthesia/analgesia or lumbar puncture, monitor frequently to detect any signs or symptoms of neurological impairment, such as midline back pain, sensory and motor deficits (numbness, tingling, or weakness in lower limbs), bowel and/or bladder dysfunction. Instruct patients to immediately report if they experience any of the above signs or symptoms. If signs or symptoms of spinal hematoma are suspected, initiate urgent diagnosis and treatment including consideration for spinal cord decompression even though such treatment may not prevent or reverse neurological sequelae.

5.4 Use in Patients with Renal Impairment

Nonvalvular Atrial Fibrillation

Periodically assess renal function as clinically indicated (i.e., more frequently in situations in which renal function may decline) and adjust therapy accordingly [see Dosage and Administration (2.1)] . Consider dose adjustment or discontinuation of XARELTO in patients who develop acute renal failure while on XARELTO [see Use in Specific Populations (8.6)].

Treatment of Deep Vein Thrombosis (DVT), Pulmonary Embolism (PE), and Reduction in the Risk of Recurrence of DVT and of PE

In patients with CrCl <30 mL/min, rivaroxaban exposure and pharmacodynamic effects are increased compared to patients with normal renal function. There are limited clinical data in patients with CrCl 15 to <30 mL/min; therefore, observe closely and promptly evaluate any signs or symptoms of blood loss in these patients. There are no clinical data in patients with CrCl <15 mL/min (including patients on dialysis); therefore, avoid the use of XARELTO in these patients.

Discontinue XARELTO in patients who develop acute renal failure while on treatment [see Use in Specific Populations (8.6)] .

Prophylaxis of Deep Vein Thrombosis Following Hip or Knee Replacement Surgery

In patients with CrCl <30 mL/min, rivaroxaban exposure and pharmacodynamic effects are increased compared to patients with normal renal function. There are limited clinical data in patients with CrCl 15 to <30 mL/min; therefore, observe closely and promptly evaluate any signs or symptoms of blood loss in these patients. There are no clinical data in patients with CrCl <15 mL/min (including patients on dialysis); therefore, avoid the use of XARELTO in these patients.

Discontinue XARELTO in patients who develop acute renal failure while on treatment [see Use in Specific Populations (8.6)].

Prophylaxis of Venous Thromboembolism in Acutely Ill Medical Patients at Risk for Thromboembolic Complications Not at High Risk of Bleeding

In patients with CrCl <30 mL/min, rivaroxaban exposure and pharmacodynamic effects are increased compared to patients with normal renal function. There are limited clinical data in patients with CrCl 15 to <30 mL/min; therefore, observe closely and promptly evaluate any signs or symptoms of blood loss in these patients. There are no clinical data in patients with CrCl <15 mL/min (including patients on dialysis); therefore, avoid the use of XARELTO in these patients.

Discontinue XARELTO in patients who develop acute renal failure while on treatment [see Use in Specific Populations (8.6)].

Pediatric Patients

There are limited clinical data in pediatric patients 1 year or older with moderate or severe renal impairment (eGFR <50 mL/min/1.73 m^2); therefore, avoid the use of XARELTO in these patients.

There are no clinical data in pediatric patients younger than 1 year with serum creatinine results above 97.5thpercentile; therefore, avoid the use of XARELTO in these patients [see Dosage and Administration (2.2)and Use in Specific Populations (8.6)] .

5.5 Use in Patients with Hepatic Impairment

No clinical data are available for adult patients with severe hepatic impairment.

Avoid use of XARELTO in patients with moderate (Child-Pugh B) and severe (Child-Pugh C) hepatic impairment or with any hepatic disease associated with coagulopathy since drug exposure and bleeding risk may be increased [see Use in Specific Populations (8.7)] .

No clinical data are available in pediatric patients with hepatic impairment.

5.6 Use with P-gp and Strong CYP3A Inhibitors or Inducers

Avoid concomitant use of XARELTO with known combined P-gp and strong CYP3A inhibitors [see Drug Interactions (7.2)] .

Avoid concomitant use of XARELTO with drugs that are known combined P-gp and strong CYP3A inducers [see Drug Interactions (7.3)] .

5.7 Risk of Pregnancy-Related Hemorrhage

In pregnant women, XARELTO should be used only if the potential benefit justifies the potential risk to the mother and fetus. XARELTO dosing in pregnancy has not been studied. The anticoagulant effect of XARELTO cannot be monitored with standard laboratory testing. Promptly evaluate any signs or symptoms suggesting blood loss (e.g., a drop in hemoglobin and/or hematocrit, hypotension, or fetal distress) [see Warnings and Precautions (5.2)and Use in Specific Populations (8.1)] .

5.8 Patients with Prosthetic Heart Valves

On the basis of the GALILEO study, use of XARELTO is not recommended in patients who have had transcatheter aortic valve replacement (TAVR) because patients randomized to XARELTO experienced higher rates of death and bleeding compared to those randomized to an anti-platelet regimen. The safety and efficacy of XARELTO have not been studied in patients with other prosthetic heart valves or other valve procedures. Use of XARELTO is not recommended in patients with prosthetic heart valves.

5.9 Acute PE in Hemodynamically Unstable Patients or Patients Who Require Thrombolysis or Pulmonary Embolectomy

Initiation of XARELTO is not recommended acutely as an alternative to unfractionated heparin in patients with pulmonary embolism who present with hemodynamic instability or who may receive thrombolysis or pulmonary embolectomy.

5.10 Increased Risk of Thrombosis in Patients with Triple Positive Antiphospholipid Syndrome

Direct-acting oral anticoagulants (DOACs), including XARELTO, are not recommended for use in patients with triple-positive antiphospholipid syndrome (APS). For patients with APS (especially those who are triple positive [positive for lupus anticoagulant, anticardiolipin, and anti-beta 2-glycoprotein I antibodies]), treatment with DOACs has been associated with increased rates of recurrent thrombotic events compared with vitamin K antagonist therapy.

6 ADVERSE REACTIONS

The following clinically significant adverse reactions are also discussed in other sections of the labeling:

- Increased Risk of Stroke After Discontinuation in Nonvalvular Atrial Fibrillation [see Boxed Warningand Warnings and Precautions (5.1)]
- Bleeding Risk [see Warnings and Precautions (5.2, 5.4, 5.5, 5.6, 5.7)]
- Spinal/Epidural Hematoma [see Boxed Warningand Warnings and Precautions (5.3)]

6.1 Clinical Trials Experience

Because clinical trials are conducted under widely varying conditions, adverse reaction rates observed in the clinical trials of a drug cannot be directly compared to rates in the clinical trials of another drug and may not reflect the rates observed in clinical practice.

During clinical development for the approved indications, 34,947 adult patients were exposed to XARELTO.

Hemorrhage

The most common adverse reactions with XARELTO were bleeding complications [see Warnings and Precautions (5.2)] .

Nonvalvular Atrial Fibrillation

In the ROCKET AF trial, the most frequent adverse reactions associated with permanent drug discontinuation were bleeding events, with incidence rates of 4.3% for XARELTO vs. 3.1% for warfarin. The incidence of discontinuations for non-bleeding adverse events was similar in both treatment groups.

Table 5 shows the number of patients experiencing various types of bleeding events in the ROCKET AF trial.

Table 5: Bleeding Events in ROCKET AF [Major bleeding events within each subcategory were counted once per patient, but patients may have contributed events to multiple subcategories. These events occurred during treatment or within 2 days of stopping treatment.] - On Treatment Plus 2 Days
Parameter | XARELTO N=7111 n (%/year) | Warfarin N=7125 n (%/year) | XARELTO vs. Warfarin HR (95% CI)
Major Bleeding [Defined as clinically overt bleeding associated with a decrease in hemoglobin of ≥2 g/dL, a transfusion of ≥2 units of packed red blood cells or whole blood, bleeding at a critical site, or with a fatal outcome.] | 395 (3.6) | 386 (3.5) | 1.04 (0.90, 1.20)
Intracranial Hemorrhage (ICH) [Intracranial bleeding events included intraparenchymal, intraventricular, subdural, subarachnoid and/or epidural hematoma.] | 55 (0.5) | 84 (0.7) | 0.67 (0.47, 0.93)
Hemorrhagic Stroke [Hemorrhagic stroke in this table specifically refers to non-traumatic intraparenchymal and/or intraventricular hematoma in patients on treatment plus 2 days.] | 36 (0.3) | 58 (0.5) | 0.63 (0.42, 0.96)
Other ICH | 19 (0.2) | 26 (0.2) | 0.74 (0.41, 1.34)
Gastrointestinal (GI) [Gastrointestinal bleeding events included upper GI, lower GI, and rectal bleeding.] | 221 (2.0) | 140 (1.2) | 1.61 (1.30, 1.99)
Fatal Bleeding [Fatal bleeding is adjudicated death with the primary cause of death from bleeding.] | 27 (0.2) | 55 (0.5) | 0.50 (0.31, 0.79)
ICH | 24 (0.2) | 42 (0.4) | 0.58 (0.35, 0.96)
Non-intracranial | 3 (0.0) | 13 (0.1) | 0.23 (0.07, 0.82)
Abbreviations: HR = Hazard Ratio, CI = Confidence interval, CRNM = Clinically Relevant Non-Major.

Figure 1 shows the risk of major bleeding events across major subgroups.

Figure 1: Risk of Major Bleeding Events by Baseline Characteristics in ROCKET AF – On Treatment Plus 2 Days

Note: The figure above presents effects in various subgroups all of which are baseline characteristics and all of which were pre-specified (diabetic status was not pre-specified in the subgroup but was a criterion for the CHADS2 score). The 95% confidence limits that are shown do not take into account how many comparisons were made, nor do they reflect the effect of a particular factor after adjustment for all other factors. Apparent homogeneity or heterogeneity among groups should not be over-interpreted.

Treatment of Deep Vein Thrombosis (DVT) and/or Pulmonary Embolism (PE)

EINSTEIN DVT and EINSTEIN PE Studies

In the pooled analysis of the EINSTEIN DVT and EINSTEIN PE clinical studies, the most frequent adverse reactions leading to permanent drug discontinuation were bleeding events, with XARELTO vs. enoxaparin/Vitamin K antagonist (VKA) incidence rates of 1.7% vs. 1.5%, respectively. The mean duration of treatment was 208 days for XARELTO-treated patients and 204 days for enoxaparin/VKA-treated patients.

Table 6 shows the number of patients experiencing major bleeding events in the pooled analysis of the EINSTEIN DVT and EINSTEIN PE studies.

Table 6: Bleeding Events [Bleeding event occurred after randomization and up to 2 days after the last dose of study drug. Although a patient may have had 2 or more events, the patient is counted only once in a category.] in the Pooled Analysis of EINSTEIN DVT and EINSTEIN PE Studies
Parameter | XARELTO [Treatment schedule in EINSTEIN DVT and EINSTEIN PE studies: XARELTO 15 mg twice daily for 3 weeks followed by 20 mg once daily; enoxaparin/VKA [enoxaparin: 1 mg/kg twice daily, VKA: individually titrated doses to achieve a target INR of 2.5 (range: 2.0–3.0)]] N=4130 n (%) | Enoxaparin/VKA N=4116 n (%)
Major bleeding event | 40 (1.0) | 72 (1.7)
Fatal bleeding | 3 (<0.1) | 8 (0.2)
Intracranial | 2 (<0.1) | 4 (<0.1)
Non-fatal critical organ bleeding | 10 (0.2) | 29 (0.7)
Intracranial [Treatment-emergent major bleeding events with at least >2 subjects in any pooled treatment group] | 3 (<0.1) | 10 (0.2)
Retroperitoneal | 1 (<0.1) | 8 (0.2)
Intraocular | 3 (<0.1) | 2 (<0.1)
Intra-articular | 0 | 4 (<0.1)
Non-fatal non-critical organ bleeding [Major bleeding which is not fatal or in a critical organ, but resulting in a decrease in Hb ≥ 2 g/dL and/or transfusion of ≥2 units of whole blood or packed red blood cells] | 27 (0.7) | 37 (0.9)
Decrease in Hb ≥ 2 g/dL | 28 (0.7) | 42 (1.0)
Transfusion of ≥2 units of whole blood or packed red blood cells | 18 (0.4) | 25 (0.6)
Clinically relevant non-major bleeding | 357 (8.6) | 357 (8.7)
Any bleeding | 1169 (28.3) | 1153 (28.0)

Reduction in the Risk of Recurrence of DVT and/or PE

EINSTEIN CHOICE Study

In the EINSTEIN CHOICE clinical study, the most frequent adverse reactions associated with permanent drug discontinuation were bleeding events, with incidence rates of 1% for XARELTO 10 mg, 2% for XARELTO 20 mg, and 1% for acetylsalicylic acid (aspirin) 100 mg. The mean duration of treatment was 293 days for XARELTO 10 mg-treated patients and 286 days for aspirin 100 mg-treated patients.

Table 7 shows the number of patients experiencing bleeding events in the EINSTEIN CHOICE study.

Table 7: Bleeding Events [Bleeding event occurred after the first dose and up to 2 days after the last dose of study drug. Although a patient may have had 2 or more events, the patient is counted only once in a category.] in EINSTEIN CHOICE
Parameter | XARELTO [Treatment schedule: XARELTO 10 mg once daily or aspirin 100 mg once daily.] 10 mg N=1127 n (%) | Acetylsalicylic Acid (aspirin) 100 mg N=1131 n (%)
Major bleeding event | 5 (0.4) | 3 (0.3)
Fatal bleeding | 0 | 1 (<0.1)
Non-fatal critical organ bleeding | 2 (0.2) | 1 (<0.1)
Non-fatal non-critical organ bleeding [Major bleeding which is not fatal or in a critical organ, but resulting in a decrease in Hb ≥ 2 g/dL and/or transfusion of ≥ 2 units of whole blood or packed red blood cells.] | 3 (0.3) | 1 (<0.1)
Clinically relevant non-major (CRNM) bleeding [Bleeding which was clinically overt, did not meet the criteria for major bleeding, but was associated with medical intervention, unscheduled contact with a physician, temporary cessation of treatment, discomfort for the patient, or impairment of activities of daily life.] | 22 (2.0) | 20 (1.8)
Any bleeding | 151 (13.4) | 138 (12.2)

In the EINSTEIN CHOICE study, there was an increased incidence of bleeding, including major and CRNM bleeding in the XARELTO 20 mg group compared to the XARELTO 10 mg or aspirin 100 mg groups.

Prophylaxis of Deep Vein Thrombosis Following Hip or Knee Replacement Surgery

In the RECORD clinical trials, the overall incidence rate of adverse reactions leading to permanent treatment discontinuation was 3.7% with XARELTO.

The rates of major bleeding events and any bleeding events observed in patients in the RECORD clinical trials are shown in Table 8.

Table 8: Bleeding Events [Bleeding events occurring any time following the first dose of double-blind study medication (which may have been prior to administration of active drug) until two days after the last dose of double-blind study medication. Patients may have more than one event.] in Patients Undergoing Hip or Knee Replacement Surgeries (RECORD 1–3)
 | XARELTO 10 mg | Enoxaparin [Includes the placebo-controlled period for RECORD 2, enoxaparin dosing was 40 mg once daily (RECORD 1–3)]
Total treated patients | N=4487 n (%) | N=4524 n (%)
Major bleeding event | 14 (0.3) | 9 (0.2)
Fatal bleeding | 1 (<0.1) | 0
Bleeding into a critical organ | 2 (<0.1) | 3 (0.1)
Bleeding that required re-operation | 7 (0.2) | 5 (0.1)
Extra-surgical site bleeding requiring transfusion of >2 units of whole blood or packed cells | 4 (0.1) | 1 (<0.1)
Any bleeding event [Includes major bleeding events] | 261 (5.8) | 251 (5.6)
Hip Surgery Studies | N=3281 n (%) | N=3298 n (%)
Major bleeding event | 7 (0.2) | 3 (0.1)
Fatal bleeding | 1 (<0.1) | 0
Bleeding into a critical organ | 1 (<0.1) | 1 (<0.1)
Bleeding that required re-operation | 2 (0.1) | 1 (<0.1)
Extra-surgical site bleeding requiring transfusion of >2 units of whole blood or packed cells | 3 (0.1) | 1 (<0.1)
Any bleeding event | 201 (6.1) | 191 (5.8)
Knee Surgery Study | N=1206 n (%) | N=1226 n (%)
Major bleeding event | 7 (0.6) | 6 (0.5)
Fatal bleeding | 0 | 0
Bleeding into a critical organ | 1 (0.1) | 2 (0.2)
Bleeding that required re-operation | 5 (0.4) | 4 (0.3)
Extra-surgical site bleeding requiring transfusion of >2 units of whole blood or packed cells | 1 (0.1) | 0
Any bleeding event | 60 (5.0) | 60 (4.9)

Following XARELTO treatment, the majority of major bleeding complications (≥60%) occurred during the first week after surgery.

Prophylaxis of Venous Thromboembolism in Acutely Ill Medical Patients at Risk for Thromboembolic Complications Not at High Risk of Bleeding

In the MAGELLAN study, the most frequent adverse reactions associated with permanent drug discontinuation were bleeding events. Cases of pulmonary hemorrhage and pulmonary hemorrhage with bronchiectasis were observed. Patients with bronchiectasis/pulmonary cavitation, active cancer (i.e., undergoing acute, in-hospital cancer treatment), dual antiplatelet therapy or active gastroduodenal ulcer or any bleeding in the previous three months all had an excess of bleeding with XARELTO compared with enoxaparin/placebo and are excluded from all MAGELLAN data presented in Table 9. The incidence of bleeding leading to drug discontinuation was 2.5% for XARELTO vs. 1.4% for enoxaparin/placebo.

Table 9 shows the number of patients experiencing various types of bleeding events in the MAGELLAN study.

Table 9: Bleeding Events in MAGELLAN [Patients at high risk of bleeding (i.e. bronchiectasis/pulmonary cavitation, active cancer, dual antiplatelet therapy or active gastroduodenal ulcer or any bleeding in the previous three months) were excluded.] Study–Safety Analysis Set - On Treatment Plus 2 Days
MAGELLAN Study [Patients received either XARELTO or placebo once daily for 35 ±4 days starting in hospital and continuing post hospital discharge or received enoxaparin or placebo once daily for 10 ±4 days in the hospital.] | XARELTO 10 mg N=3218 n (%) | Enoxaparin 40 mg /placebo N=3229 n (%)
Major bleeding [Defined as clinically overt bleeding associated with a drop in hemoglobin of ≥2 g/dL, a transfusion of ≥2 units of packed red blood cells or whole blood, bleeding at a critical site, or with a fatal outcome.] [Major bleeding events within each subcategory were counted once per patient, but patients may have contributed events to multiple subcategories. These events occurred during treatment or within 2 days of stopping treatment.] | 22 (0.7) | 15 (0.5)
Critical site bleeding | 7 (0.2) | 4 (0.1)
Fatal bleeding [Fatal bleeding is adjudicated death with the primary cause of death from bleeding.] | 3 (<0.1) | 1 (<0.1)
Clinically relevant non-major bleeding events (CRNM) | 93 (2.9) | 34 (1.1)

Reduction of Risk of Major Cardiovascular Events in Patients with CAD

In the COMPASS trial overall, the most frequent adverse reactions associated with permanent drug discontinuation were bleeding events, with incidence rates of 2.7% for XARELTO 2.5 mg twice daily vs. 1.2% for placebo on background therapy for all patients with aspirin 100 mg once daily. The incidences of important bleeding events in the CAD and PAD populations in COMPASS were similar.

Table 10 shows the number of patients experiencing various types of major bleeding events in the COMPASS trial.

Table 10: Major Bleeding Events in COMPASS - On Treatment Plus 2 Days [Major bleeding events within each subcategory were counted once per patient, but patients may have contributed events to multiple subcategories. These events occurred during treatment or within 2 days of stopping treatment in the safety analysis set in COMPASS patients.]
Parameter | XARELTO [Treatment schedule: XARELTO 2.5 mg twice daily or placebo. All patients received background therapy with aspirin 100 mg once daily.] N=9134 n (%/year) | Placebo N=9107 n (%/year) | XARELTO vs. Placebo HR (95 % CI)
Modified ISTH Major Bleeding [Defined as i) fatal bleeding, or ii) symptomatic bleeding in a critical area or organ, such as intraarticular, intramuscular with compartment syndrome, intraspinal, intracranial, intraocular, respiratory, pericardial, liver, pancreas, retroperitoneal, adrenal gland or kidney; or iii) bleeding into the surgical site requiring reoperation, or iv) bleeding leading to hospitalization.] | 263 (1.6) | 144 (0.9) | 1.8 (1.5, 2.3)
- Fatal bleeding event Intracranial hemorrhage (ICH) Non-intracranial | 12 (<0.1) 6 (<0.1) 6 (<0.1) | 8 (<0.1) 3 (<0.1) 5 (<0.1) | 1.5 (0.6, 3.7) 2.0 (0.5, 8.0) 1.2 (0.4, 4.0)
- Symptomatic bleeding in critical organ (non-fatal) - ICH (fatal and non-fatal) Hemorrhagic Stroke Other ICH | 58 (0.3) 23 (0.1) 18 (0.1) 6 (<0.1) | 43 (0.3) 21 (0.1) 13 (<0.1) 9 (<0.1) | 1.4 (0.9, 2.0) 1.1 (0.6, 2.0) 1.4 (0.7, 2.8) 0.7 (0.2, 1.9)
- Bleeding into the surgical site requiring reoperation (non-fatal, not in critical organ) | 7 (<0.1) | 6 (<0.1) | 1.2 (0.4, 3.5)
- Bleeding leading to hospitalization (non-fatal, not in critical organ, not requiring reoperation) | 188 (1.1) | 91 (0.5) | 2.1 (1.6, 2.7)
Major GI bleeding | 117 (0.7) | 49 (0.3) | 2.4 (1.7, 3.4)
CI: confidence interval; HR: hazard ratio; ISTH: International Society on Thrombosis and Hemostasis

Reduction of Risk of Major Thrombotic Vascular Events in Patients with Peripheral Artery Disease (PAD), Including Patients after Lower Extremity Revascularization due to Symptomatic PAD

The incidence of premature permanent discontinuation due to bleeding events for XARELTO 2.5 mg twice daily vs. placebo on background therapy with aspirin 100 mg once daily in VOYAGER was 4.1% vs. 1.6% and in COMPASS PAD was 2.7% vs. 1.3%, respectively.

Table 11 shows the number of patients experiencing various types of TIMI (Thrombolysis in Myocardial Infarction) major bleeding events in the VOYAGER trial. The most common site of bleeding was gastrointestinal.

Table 11: Major Bleeding Events [Major bleeding events within each subcategory were counted once per patient, but patients may have contributed events to multiple subcategories.] in VOYAGER- On Treatment Plus 2 Days
 | XARELTO [Treatment schedule: XARELTO 2.5 mg twice daily or placebo. All patients received background therapy with aspirin 100 mg once daily.] N=3256 |  | Placebo N=3248 |  | XARELTO vs. Placebo HR (95 % CI)
Parameter | n (%) | Event rate %/year | n (%) | Event rate %/year | XARELTO vs. Placebo HR (95 % CI)
TIMI Major Bleeding (CABG/non-CABG) | 62 (1.9) | 0.96 | 44 (1.4) | 0.67 | XARELTO vs. Placebo HR (95 % CI) | 1.4 (1.0, 2.1)
Fatal bleeding | 6 (0.2) | 0.09 | 6 (0.2) | 0.09 | 1.0 (0.3, 3.2)
Intracranial bleeding | 13 (0.4) | 0.20 | 17 (0.5) | 0.26 | 0.8 (0.4, 1.6)
Clinically overt signs of hemorrhage associated with a drop in hemoglobin of ≥5 g/dL or drop in hematocrit of ≥15% | 46 (1.4) | 0.71 | 24 (0.7) | 0.36 | 1.9 (1.2, 3.2)
CABG: Coronary artery bypass graft; CI: confidence interval; HR: hazard ratio; TIMI: Thrombolysis in Myocardial Infarction Bleeding Criteria

Other Adverse Reactions

Non-hemorrhagic adverse reactions reported in ≥1% of XARELTO-treated patients in the EINSTEIN DVT and EINSTEIN PE studies are shown in Table 12.

Table 12: Other Adverse Reactions [Adverse reaction with Relative Risk >1.5 for XARELTO versus comparator] Reported by ≥1% of XARELTO-Treated Patients in EINSTEIN DVT and EINSTEIN PE Studies
Body System Adverse Reaction
EINSTEIN DVT Study | XARELTO 20 mg N=1718 n (%) | Enoxaparin/VKA N=1711 n (%)
Gastrointestinal disorders
Abdominal pain | 46 (2.7) | 25 (1.5)
General disorders and administration site conditions
Fatigue | 24 (1.4) | 15 (0.9)
Musculoskeletal and connective tissue disorders
Back pain | 50 (2.9) | 31 (1.8)
Muscle spasm | 23 (1.3) | 13 (0.8)
Nervous system disorders
Dizziness | 38 (2.2) | 22 (1.3)
Psychiatric disorders
Anxiety | 24 (1.4) | 11 (0.6)
Depression | 20 (1.2) | 10 (0.6)
Insomnia | 28 (1.6) | 18 (1.1)
EINSTEIN PE Study | XARELTO 20 mg N=2412 n (%) | Enoxaparin/VKA N=2405 n (%)
Skin and subcutaneous tissue disorders
Pruritus | 53 (2.2) | 27 (1.1)

Non-hemorrhagic adverse reactions reported in ≥1% of XARELTO-treated patients in RECORD 1–3 studies are shown in Table 13.

Table 13: Other Adverse Drug Reactions [Adverse reaction occurring any time following the first dose of double-blind medication, which may have been prior to administration of active drug, until two days after the last dose of double-blind study medication] Reported by ≥1% of XARELTO-Treated Patients in RECORD 1–3 Studies
Body System Adverse Reaction | XARELTO 10 mg N=4487 n (%) | Enoxaparin [Includes the placebo-controlled period of RECORD 2, enoxaparin dosing was 40 mg once daily (RECORD 1–3)] N=4524 n (%)
Injury, poisoning and procedural complications
Wound secretion | 125 (2.8) | 89 (2.0)
Musculoskeletal and connective tissue disorders
Pain in extremity | 74 (1.7) | 55 (1.2)
Muscle spasm | 52 (1.2) | 32 (0.7)
Nervous system disorders
Syncope | 55 (1.2) | 32 (0.7)
Skin and subcutaneous tissue disorders
Pruritus | 96 (2.1) | 79 (1.8)
Blister | 63 (1.4) | 40 (0.9)

Pediatric Patients

Treatment of Venous Thromboembolism and Reduction in Risk of Recurrent Venous Thromboembolism in Pediatric Patients

The safety assessment is based on data from the EINSTEIN Junior Phase 3 study in 491 patients from birth to less than 18 years of age. Patients were randomized 2:1 to receive body weight-adjusted doses of XARELTO or comparator (unfractionated heparin, low molecular weight heparin, fondaparinux or VKA).

Discontinuation due to bleeding events occurred in 6 (1.8%) patients in the XARELTO group and 3 (1.9%) patients in the comparator group.

Table 14 shows the number of patients experiencing bleeding events in the EINSTEIN Junior study. In female patients who had experienced menarche, ages 12 to <18 years of age, menorrhagia occurred in 23 (27%) female patients in the XARELTO group and 5 (10%) female patients in the comparator group.

Table 14: Bleeding Events in EINSTEIN Junior Study – Safety Analysis Set - Main Treatment Period [These events occurred after randomization until 3 months of treatment (1 month for patients <2 years with central venous catheter-related VTE (CVC-VTE). Patients may have more than one event.]
Parameter | XARELTO [Treatment schedule: body weight-adjusted doses of XARELTO; randomized 2:1 (XARELTO: Comparator).] N=329 n (%) | Comparator Group [Unfractionated heparin (UFH), low molecular weight heparin (LMWH), fondaparinux or VKA.] N=162 n (%)
Major bleeding [Defined as clinically overt bleeding associated with a decrease in hemoglobin of ≥2 g/dL, a transfusion of ≥2 units of packed red blood cells or whole blood, bleeding at a critical site, or with a fatal outcome.] | 0 | 2 (1.2)
Clinically relevant non-major bleeding [Defined as clinically overt bleeding, which did not meet the criteria for major bleeding, but was associated with medical intervention, unscheduled contact with a physician, temporary cessation of treatment, discomfort for the patient, or impairment of activities of daily life.] | 10 (3.0) | 1 (0.6)
Trivial bleeding | 113 (34.3) | 44 (27.2)
Any bleeding | 119 (36.2) | 45 (27.8)

Non-bleeding adverse reactions reported in ≥5% of XARELTO-treated patients are shown in Table 15.

Table 15: Other Adverse Reactions [Adverse reaction with Relative Risk >1.5 for XARELTO versus comparator.] Reported in XARELTO-Treated Patients by ≥5% in EINSTEIN Junior Study
Adverse Reaction | XARELTO N=329 n (%) | Comparator Group N=162 n (%)
Pain in extremity | 23 (7) | 7 (4.3)
Fatigue [The following terms were combined: fatigue, asthenia.] | 23 (7) | 7 (4.3)

A clinically relevant adverse reaction in XARELTO-treated patients was vomiting (10.6% in the XARELTO group vs 8% in the comparator group).

Thromboprophylaxis in Pediatric Patients with Congenital Heart Disease (CHD) after the Fontan Procedure

The data below are based on Part B of the UNIVERSE study which was designed to evaluate the safety and efficacy of XARELTO for thromboprophylaxis in 98 children with CHD after the Fontan procedure who took at least one dose of study drug. Patients in Part B were randomized 2:1 to receive either body weight-adjusted doses of XARELTO or aspirin (approximately 5 mg/kg).

Discontinuation due to bleeding events occurred in 1 (1.6%) patient in the XARELTO group and no patients in the aspirin group.

Table 16 shows the number of patients experiencing bleeding events in the UNIVERSE study.

Table 16: Bleeding Events in UNIVERSE Study - Safety Analysis Set - On Treatment Plus 2 Days
Parameter | XARELTO [Treatment schedule: body weight-adjusted doses of XARELTO or aspirin (approximately 5 mg/kg); randomized 2:1 (XARELTO: Aspirin).] N=64 n (%) | Aspirin N=34 n (%)
Major Bleeding [Defined as clinically overt bleeding associated with a decrease in hemoglobin of ≥2 g/dL, a transfusion of the equivalent of ≥2 units of packed red blood cells or whole blood, bleeding at a critical site, or with a fatal outcome.] | 1 (1.6) | 0
Epistaxis leading to transfusion | 1 (1.6) | 0
Clinically relevant non-major (CRNM) bleeding [Defined as clinically overt bleeding, which did not meet the criteria for major bleeding, but was associated with medical intervention, unscheduled contact with a physician, temporary cessation of treatment, discomfort for the patient, or impairment of activities of daily life.] | 4 (6.3) | 3 (8.8)
Trivial bleeding | 21 (32.8) | 12 (35.3)
Any bleeding | 23 (35.9) | 14 (41.2)

Non-bleeding adverse reactions reported in ≥5% of XARELTO-treated patients are shown in Table 17.

Table 17: Other Adverse Reactions [Adverse reaction with Relative Risk >1.5 for XARELTO versus aspirin.] Reported by ≥5% of XARELTO-Treated Patients in UNIVERSE Study (Part B)
Adverse Reaction | XARELTO N=64 n (%) | Aspirin N=34 n (%)
Cough | 10 (15.6) | 3 (8.8)
Vomiting | 9 (14.1) | 3 (8.8)
Gastroenteritis [The following terms were combined: Gastroenteritis: gastroenteritis, gastroenteritis viral Rash: rash, rash maculo-papular, viral rash] | 8 (12.5) | 1 (2.9)
Rash | 6 (9.4) | 2 (5.9)

6.2 Postmarketing Experience

The following adverse reactions have been identified during post-approval use of XARELTO. Because these reactions are reported voluntarily from a population of uncertain size, it is not always possible to reliably estimate their frequency or establish a causal relationship to drug exposure.

Blood and lymphatic system disorders:agranulocytosis, thrombocytopenia

Hepatobiliary disorders:jaundice, cholestasis, hepatitis (including hepatocellular injury)

Immune system disorders:hypersensitivity, anaphylactic reaction, anaphylactic shock, angioedema

Nervous system disorders:hemiparesis

Renal disorders:Anticoagulant-related nephropathy

Respiratory, thoracic and mediastinal disorders:Eosinophilic pneumonia

Skin and subcutaneous tissue disorders:Stevens-Johnson syndrome, drug reaction with eosinophilia and systemic symptoms (DRESS)

Injury, poisoning and procedural complications:Atraumatic splenic rupture

7 DRUG INTERACTIONS

7.1 General Inhibition and Induction Properties

Rivaroxaban is a substrate of CYP3A4/5, CYP2J2, and the P-gp and ATP-binding cassette G2 (ABCG2) transporters. Combined P-gp and strong CYP3A inhibitors increase exposure to rivaroxaban and may increase the risk of bleeding. Combined P-gp and strong CYP3A inducers decrease exposure to rivaroxaban and may increase the risk of thromboembolic events.

7.2 Drugs that Inhibit Cytochrome P450 3A Enzymes and Drug Transport Systems

Interaction with Combined P-gp and Strong CYP3A Inhibitors

Avoid concomitant administration of XARELTO with known combined P-gp and strong CYP3A inhibitors (e.g., ketoconazole and ritonavir) [see Warnings and Precautions (5.6)and Clinical Pharmacology (12.3)] .

Although clarithromycin is a combined P-gp and strong CYP3A inhibitor, pharmacokinetic data suggests that no precautions are necessary with concomitant administration with XARELTO as the change in exposure is unlikely to affect the bleeding risk [see Clinical Pharmacology (12.3)] .

Interaction with Combined P-gp and Moderate CYP3A Inhibitors in Patients with Renal Impairment

XARELTO should not be used in patients with CrCl 15 to <80 mL/min who are receiving concomitant combined P-gp and moderate CYP3A inhibitors (e.g., erythromycin) unless the potential benefit justifies the potential risk [see Warnings and Precautions (5.4)and Clinical Pharmacology (12.3)] .

7.3 Drugs that Induce Cytochrome P450 3A Enzymes and Drug Transport Systems

Avoid concomitant use of XARELTO with drugs that are combined P-gp and strong CYP3A inducers (e.g., carbamazepine, phenytoin, rifampin, St. John's wort) [see Warnings and Precautions (5.6)and Clinical Pharmacology (12.3)] .

7.4 Anticoagulants and NSAIDs/Aspirin

Coadministration of enoxaparin, warfarin, aspirin, clopidogrel and chronic NSAID use may increase the risk of bleeding [see Clinical Pharmacology (12.3)].

Avoid concurrent use of XARELTO with other anticoagulants due to increased bleeding risk unless benefit outweighs risk. Promptly evaluate any signs or symptoms of blood loss if patients are treated concomitantly with aspirin, other platelet aggregation inhibitors, or NSAIDs [see Warnings and Precautions (5.2)] .

8 USE IN SPECIFIC POPULATIONS

8.1 Pregnancy

Risk Summary

The limited available data on XARELTO in pregnant women are insufficient to inform a drug-associated risk of adverse developmental outcomes. Use XARELTO with caution in pregnant patients because of the potential for pregnancy related hemorrhage and/or emergent delivery. The anticoagulant effect of XARELTO cannot be reliably monitored with standard laboratory testing. Consider the benefits and risks of XARELTO for the mother and possible risks to the fetus when prescribing XARELTO to a pregnant woman [see Warnings and Precautions (5.2, 5.7)] .

Adverse outcomes in pregnancy occur regardless of the health of the mother or the use of medications. The estimated background risk of major birth defects and miscarriage for the indicated populations is unknown. In the U.S. general population, the estimated background risk of major birth defects and miscarriage in clinically recognized pregnancies is 2–4% and 15–20%, respectively.

Clinical Considerations

Disease-Associated Maternal and/or Embryo/Fetal Risk

Pregnancy is a risk factor for venous thromboembolism and that risk is increased in women with inherited or acquired thrombophilias. Pregnant women with thromboembolic disease have an increased risk of maternal complications including pre-eclampsia. Maternal thromboembolic disease increases the risk for intrauterine growth restriction, placental abruption and early and late pregnancy loss.

Fetal/Neonatal Adverse Reactions

Based on the pharmacologic activity of Factor Xa inhibitors and the potential to cross the placenta, bleeding may occur at any site in the fetus and/or neonate.

Labor or Delivery

All patients receiving anticoagulants, including pregnant women, are at risk for bleeding and this risk may be increased during labor or delivery [see Warnings and Precautions (5.7)]. The risk of bleeding should be balanced with the risk of thrombotic events when considering the use of XARELTO in this setting.

Data

Human Data

There are no adequate or well-controlled studies of XARELTO in pregnant women, and dosing for pregnant women has not been established. Post-marketing experience is currently insufficient to determine a rivaroxaban-associated risk for major birth defects or miscarriage. In an in vitroplacenta perfusion model, unbound rivaroxaban was rapidly transferred across the human placenta.

Animal Data

Rivaroxaban crosses the placenta in animals. Rivaroxaban increased fetal toxicity (increased resorptions, decreased number of live fetuses, and decreased fetal body weight) when pregnant rabbits were given oral doses of ≥10 mg/kg rivaroxaban during the period of organogenesis. This dose corresponds to about 4 times the human exposure of unbound drug, based on AUC comparisons at the highest recommended human dose of 20 mg/day. Fetal body weights decreased when pregnant rats were given oral doses of 120 mg/kg during the period of organogenesis. This dose corresponds to about 14 times the human exposure of unbound drug. In rats, peripartal maternal bleeding and maternal and fetal death occurred at the rivaroxaban dose of 40 mg/kg (about 6 times maximum human exposure of the unbound drug at the human dose of 20 mg/day).

8.2 Lactation

Risk Summary

Rivaroxaban has been detected in human milk. There are insufficient data to determine the effects of rivaroxaban on the breastfed child or on milk production. Rivaroxaban and/or its metabolites were present in the milk of rats. The developmental and health benefits of breastfeeding should be considered along with the mother's clinical need for XARELTO and any potential adverse effects on the breastfed infant from XARELTO or from the underlying maternal condition (see Data) .

Data

Animal Data

Following a single oral administration of 3 mg/kg of radioactive [^14C]-rivaroxaban to lactating rats between Day 8 to 10 postpartum, the concentration of total radioactivity was determined in milk samples collected up to 32 hours post-dose. The estimated amount of radioactivity excreted with milk within 32 hours after administration was 2.1% of the maternal dose.

8.3 Females and Males of Reproductive Potential

Females of reproductive potential requiring anticoagulation should discuss pregnancy planning with their physician.

The risk of clinically significant uterine bleeding, potentially requiring gynecological surgical interventions, identified with oral anticoagulants including XARELTO should be assessed in females of reproductive potential and those with abnormal uterine bleeding.

8.4 Pediatric Use

The safety and effectiveness of XARELTO have been established in pediatric patients from birth to less than 18 years for the treatment of VTE and the reduction in risk of recurrent VTE. Use of XARELTO is supported in these age groups by evidence from adequate and well-controlled studies of XARELTO in adults with additional pharmacokinetic, safety and efficacy data from a multicenter, prospective, open-label, active-controlled randomized study in 500 pediatric patients from birth to less than 18 years of age. XARELTO was not studied and therefore dosing cannot be reliably determined or recommended in children less than 6 months who were less than 37 weeks of gestation at birth; had less than 10 days of oral feeding, or had a body weight of less than 2.6 kg [see Dosage and Administration (2.2), Adverse Reactions (6.1), Clinical Pharmacology (12.3)and Clinical Studies (14.8)] .

The safety and effectiveness of XARELTO have been established for use in pediatric patients aged 2 years and older with congenital heart disease who have undergone the Fontan procedure. Use of XARELTO is supported in these age groups by evidence from adequate and well-controlled studies of XARELTO in adults with additional data from a multicenter, prospective, open-label, active controlled study in 112 pediatric patients to evaluate the single- and multiple-dose pharmacokinetic properties of XARELTO and the safety and efficacy of XARELTO when used for thromboprophylaxis for 12 months in children with single ventricle physiology who had the Fontan procedure [see Dosage and Administration (2.2), Adverse Reactions (6.1), Clinical Pharmacology (12.3)and Clinical Studies (14.9)] .

Clinical studies that evaluated safety, efficacy, pharmacokinetic and pharmacodynamic data support the use of XARELTO 10 mg, 15 mg, and 20 mg tablets in pediatric patients. For the XARELTO 2.5 mg tablets, there are no safety, efficacy, pharmacokinetic and pharmacodynamic data to support the use in pediatric patients. Therefore, XARELTO 2.5 mg tablets are not recommended for use in pediatric patients.

Although not all adverse reactions identified in the adult population have been observed in clinical trials of children and adolescent patients, the same warnings and precautions for adults should be considered for children and adolescents.

8.5 Geriatric Use

Of the total number of adult patients in clinical trials for the approved indications of XARELTO (N=64,943 patients), 64 percent were 65 years and over, with 27 percent 75 years and over. In clinical trials the efficacy of XARELTO in the elderly (65 years or older) was similar to that seen in patients younger than 65 years. Both thrombotic and bleeding event rates were higher in these older patients [see Clinical Pharmacology (12.3)and Clinical Studies (14)] .

8.6 Renal Impairment

In pharmacokinetic studies, compared to healthy adult subjects with normal creatinine clearance, rivaroxaban exposure increased by approximately 44 to 64% in adult subjects with renal impairment. Increases in pharmacodynamic effects were also observed [see Clinical Pharmacology (12.3)] .

Nonvalvular Atrial Fibrillation

Patients with Chronic Kidney Disease not on Dialysis

In the ROCKET AF trial, patients with CrCl 30 to 50 mL/min were administered XARELTO 15 mg once daily resulting in serum concentrations of rivaroxaban and clinical outcomes similar to those in patients with better renal function administered XARELTO 20 mg once daily. Patients with CrCl <30 mL/min were not studied, but administration of XARELTO 15 mg once daily is expected to result in serum concentrations of rivaroxaban similar to those in patients with moderate renal impairment [see Clinical Pharmacology (12.3)] .

Patients with End-Stage Renal Disease on Dialysis

Clinical efficacy and safety studies with XARELTO did not enroll patients with end-stage renal disease (ESRD) on dialysis. In patients with ESRD maintained on intermittent hemodialysis, administration of XARELTO 15 mg once daily will result in concentrations of rivaroxaban and pharmacodynamic activity similar to those observed in the ROCKET AF study [see Clinical Pharmacology (12.2, 12.3)] . It is not known whether these concentrations will lead to similar stroke reduction and bleeding risk in patients with ESRD on dialysis as was seen in ROCKET AF.

Treatment of DVT and/or PE and Reduction in the Risk of Recurrence of DVT and/or PE

In the EINSTEIN trials, patients with CrCl values <30 mL/min at screening were excluded from the studies, but administration of XARELTO is expected to result in serum concentrations of rivaroxaban similar to those in patients with moderate renal impairment (CrCl 30 to <50 mL/min) [see Clinical Pharmacology (12.3)]. Observe closely and promptly evaluate any signs or symptoms of blood loss in patients with CrCl 15 to <30 mL/min. Avoid the use of XARELTO in patients with CrCl <15 mL/min.

Prophylaxis of DVT Following Hip or Knee Replacement Surgery

The combined analysis of the RECORD 1–3 clinical efficacy studies did not show an increase in bleeding risk for patients with CrCl 30 to 50 mL/min and reported a possible increase in total venous thromboemboli in this population. In the RECORD 1–3 trials, patients with CrCl values <30 mL/min at screening were excluded from the studies, but administration of XARELTO 10 mg once daily is expected to result in serum concentrations of rivaroxaban similar to those in patients with moderate renal impairment (CrCl 30 to <50 mL/min) [see Clinical Pharmacology (12.3)]. Observe closely and promptly evaluate any signs or symptoms of blood loss in patients with CrCl 15 to <30 mL/min. Avoid the use of XARELTO in patients with CrCl <15 mL/min.

Prophylaxis of Venous Thromboembolism in Acutely Ill Medical Patients at Risk for Thromboembolic Complications Not at High Risk of Bleeding

Patients with CrCl values <30 mL/min at screening were excluded from the MAGELLAN study. In patients with CrCl <30 mL/min a dose of XARELTO 10 mg once daily is expected to result in serum concentrations of rivaroxaban similar to those in patients with moderate renal impairment (CrCl 30 to <50 mL/min) [see Clinical Pharmacology (12.3)] . Observe closely and promptly evaluate any signs or symptoms of blood loss in patients with CrCl 15 to <30 mL/min. Avoid use of XARELTO in patients with CrCl <15 mL/min.

Reduction of Risk of Major Cardiovascular Events in Patients with CAD and Reduction of Risk of Major Thrombotic Vascular Events in Patients with PAD, Including Patients After Recent Lower Extremity Revascularization due to Symptomatic PAD

Patients with Chronic Kidney Disease not on Dialysis

Patients with a CrCl <15 mL/min at screening were excluded from COMPASS and VOYAGER, and limited data are available for patients with a CrCl of 15 to 30 mL/min. In patients with CrCl <30 mL/min, a dose of 2.5 mg XARELTO twice daily is expected to give an exposure similar to that in patients with moderate renal impairment (CrCl 30 to <50 mL/min) [see Clinical Pharmacology (12.3)] , whose efficacy and safety outcomes were similar to those with preserved renal function.

Patients with End-Stage Renal Disease on Dialysis

No clinical outcome data is available for the use of XARELTO with aspirin in patients with ESRD on dialysis since these patients were not enrolled in COMPASS or VOYAGER. In patients with ESRD maintained on intermittent hemodialysis, administration of XARELTO 2.5 mg twice daily will result in concentrations of rivaroxaban and pharmacodynamic activity similar to those observed in moderate renal impaired patients in the COMPASS study [see Clinical Pharmacology (12.2, 12.3)] . It is not known whether these concentrations will lead to similar CV risk reduction and bleeding risk in patients with ESRD on dialysis as was seen in COMPASS.

Pediatric Use

No dosage adjustment is required in patients 1 year of age or older with mild renal impairment (eGFR 50 to ≤ 80 mL/min/1.73 m^2). There are limited clinical data in pediatric patients 1 year or older with moderate or severe renal impairment (eGFR <50 mL/min/1.73 m^2); therefore, avoid the use of XARELTO in these patients.

There are no clinical data in pediatric patients younger than 1 year with serum creatinine results above 97.5thpercentile; therefore, avoid the use of XARELTO in these patients [see Dosage and Administration (2.2)] .

8.7 Hepatic Impairment

In a pharmacokinetic study, compared to healthy adult subjects with normal liver function, AUC increases of 127% were observed in adult subjects with moderate hepatic impairment (Child-Pugh B).

The safety or PK of XARELTO in patients with severe hepatic impairment (Child-Pugh C) has not been evaluated [see Clinical Pharmacology (12.3)] .

Avoid the use of XARELTO in patients with moderate (Child-Pugh B) and severe (Child-Pugh C) hepatic impairment or with any hepatic disease associated with coagulopathy.

No clinical data are available in pediatric patients with hepatic impairment.

10 OVERDOSAGE

Overdose of XARELTO may lead to hemorrhage. Discontinue XARELTO and initiate appropriate therapy if bleeding complications associated with overdosage occur. Rivaroxaban systemic exposure is not further increased at single doses >50 mg due to limited absorption. The use of activated charcoal to reduce absorption in case of XARELTO overdose may be considered. Due to the high plasma protein binding, rivaroxaban is not dialyzable [see Warnings and Precautions (5.2)and Clinical Pharmacology (12.3)] . Partial reversal of laboratory anticoagulation parameters may be achieved with use of plasma products. An agent to reverse the anti-factor Xa activity of rivaroxaban is available.

11 DESCRIPTION

Rivaroxaban, a factor Xa (FXa) inhibitor, is the active ingredient in XARELTO®Tablets and XARELTO®for oral suspension with the chemical name 5-Chloro-N-({(5S)-2-oxo-3-[4-(3-oxo-4-morpholinyl)phenyl]-1,3-oxazolidin-5-yl}methyl)-2-thiophenecarboxamide. The molecular formula of rivaroxaban is C19H18ClN3O5S and the molecular weight is 435.89. The structural formula is:

Rivaroxaban is a pure (S)-enantiomer. It is an odorless, non-hygroscopic, white to yellowish powder. Rivaroxaban is only slightly soluble in organic solvents (e.g., acetone, polyethylene glycol 400) and is practically insoluble in water and aqueous media.

Each XARELTO tablet contains 2.5 mg, 10 mg, 15 mg, or 20 mg of rivaroxaban. The inactive ingredients of XARELTO are: croscarmellose sodium, hypromellose, lactose monohydrate, magnesium stearate, microcrystalline cellulose, and sodium lauryl sulfate. Additionally, the proprietary film coating mixture used for XARELTO 2.5 mg is Opadry®Light Yellow, containing ferric oxide yellow, hypromellose, polyethylene glycol 3350, and titanium dioxide, and for XARELTO 10 mg tablets is Opadry®Pink and for XARELTO 15 mg tablets is Opadry®Red, both containing ferric oxide red, hypromellose, polyethylene glycol 3350, and titanium dioxide, and for XARELTO 20 mg tablets is Opadry®II Dark Red, containing ferric oxide red, polyethylene glycol 3350, polyvinyl alcohol (partially hydrolyzed), talc, and titanium dioxide.

XARELTO for oral suspension is supplied as granules in bottles containing 155 mg of rivaroxaban (1 mg of rivaroxaban per mL after reconstitution). The inactive ingredients are: anhydrous citric acid, hypromellose, mannitol, microcrystalline cellulose and carboxymethylcellulose sodium, sodium benzoate, sucralose, sweet and creamy flavor and xanthan gum.

12 CLINICAL PHARMACOLOGY

12.1 Mechanism of Action

XARELTO is a selective inhibitor of FXa. It does not require a cofactor (such as Anti-thrombin III) for activity. Rivaroxaban inhibits free FXa and prothrombinase activity. Rivaroxaban has no direct effect on platelet aggregation, but indirectly inhibits platelet aggregation induced by thrombin. By inhibiting FXa, rivaroxaban decreases thrombin generation.

12.2 Pharmacodynamics

Rivaroxaban produces dose-dependent inhibition of FXa activity. Clotting tests, such as prothrombin time (PT), activated partial thromboplastin time (aPTT) and HepTest®, are also prolonged dose-dependently. In children treated with rivaroxaban, the correlation between anti-factor Xa to plasma concentrations is linear with a slope close to 1.

Monitoring for anticoagulation effect of rivaroxaban using anti-FXa activity or a clotting test is not recommended.

Specific Populations

Renal Impairment

The relationship between systemic exposure and pharmacodynamic activity of rivaroxaban was altered in adult subjects with renal impairment relative to healthy control subjects [see Use in Specific Populations (8.6)] .

Table 18: Percentage Increase in Rivaroxaban PK and PD Measures in Adult Subjects with Renal Impairment Relative to Healthy Subjects from Clinical Pharmacology Studies
Measure | Parameter | Creatinine Clearance (mL/min)
Measure | Parameter | 50–79 | 30–49 | 15–29 | ESRD (on dialysis) [Separate stand-alone study.] | ESRD (post-dialysis)
Exposure | AUC | 44 | 52 | 64 | 47 | 56
FXa Inhibition | AUEC | 50 | 86 | 100 | 49 | 33
PT Prolongation | AUEC | 33 | 116 | 144 | 112 | 158
PT = Prothrombin time; FXa = Coagulation factor Xa; AUC = Area under the plasma concentration-time curve; AUEC = Area under the effect-time curve

Hepatic Impairment

Anti-Factor Xa activity was similar in adult subjects with normal hepatic function and in mild hepatic impairment (Child-Pugh A class). There is no clear understanding of the impact of hepatic impairment beyond this degree on the coagulation cascade and its relationship to efficacy and safety.

12.3 Pharmacokinetics

Absorption

The absolute bioavailability of rivaroxaban is dose-dependent. For the 2.5 mg and 10 mg dose, it is estimated to be 80% to 100% and is not affected by food. XARELTO 2.5 mg and 10 mg tablets can be taken with or without food. XARELTO 20 mg administered in the fasted state has an absolute bioavailability of approximately 66%. Coadministration of XARELTO with food increases the bioavailability of the 20 mg dose (mean AUC and Cmaxincreasing by 39% and 76% respectively with food). XARELTO 15 mg and 20 mg tablets should be taken with food [see Dosage and Administration (2.1)] .

The maximum concentrations (Cmax) of rivaroxaban appear 2 to 4 hours after tablet intake. The pharmacokinetics of rivaroxaban were not affected by drugs altering gastric pH. Coadministration of XARELTO (30 mg single dose) with the H2-receptor antagonist ranitidine (150 mg twice daily), the antacid aluminum hydroxide/magnesium hydroxide (10 mL) or XARELTO (20 mg single dose) with the PPI omeprazole (40 mg once daily) did not show an effect on the bioavailability and exposure of rivaroxaban (see Figure 3).

Absorption of rivaroxaban is dependent on the site of drug release in the GI tract. A 29% and 56% decrease in AUC and Cmaxcompared to tablet was reported when rivaroxaban granulate is released in the proximal small intestine. Exposure is further reduced when drug is released in the distal small intestine, or ascending colon. Avoid administration of rivaroxaban distal to the stomach which can result in reduced absorption and related drug exposure.

In a study with 44 healthy subjects, both mean AUC and Cmaxvalues for 20 mg rivaroxaban administered orally as a crushed tablet mixed in applesauce were comparable to that after the whole tablet. However, for the crushed tablet suspended in water and administered via an NG tube followed by a liquid meal, only mean AUC was comparable to that after the whole tablet, and Cmaxwas 18% lower.

Distribution

Protein binding of rivaroxaban in human plasma is approximately 92% to 95%, with albumin being the main binding component. The steady-state volume of distribution in healthy subjects is approximately 50 L.

Metabolism

Approximately 51% of an orally administered [^14C]-rivaroxaban dose was recovered as inactive metabolites in urine (30%) and feces (21%). Oxidative degradation catalyzed by CYP3A4/5 and CYP2J2 and hydrolysis are the major sites of biotransformation. Unchanged rivaroxaban was the predominant moiety in plasma with no major or active circulating metabolites.

Excretion

In a Phase 1 study, following the administration of [^14C]-rivaroxaban, approximately one-third (36%) was recovered as unchanged drug in the urine and 7% was recovered as unchanged drug in feces. Unchanged drug is excreted into urine, mainly via active tubular secretion and to a lesser extent via glomerular filtration (approximate 5:1 ratio). Rivaroxaban is a substrate of the efflux transporter proteins P-gp and ABCG2 (also abbreviated BCRP). Rivaroxaban's affinity for influx transporter proteins is unknown.

Rivaroxaban is a low-clearance drug, with a systemic clearance of approximately 10 L/hr in healthy volunteers following intravenous administration. The terminal elimination half-life of rivaroxaban is 5 to 9 hours in healthy subjects aged 20 to 45 years.

Specific Populations

The effects of level of renal impairment, age, body weight, and level of hepatic impairment on the pharmacokinetics of rivaroxaban are summarized in Figure 2.

Figure 2: Effect of Specific Adult Populations on the Pharmacokinetics of Rivaroxaban

[see Dosage and Administration (2.1)]

Gender

Gender did not influence the pharmacokinetics or pharmacodynamics of XARELTO.

Race

Healthy Japanese subjects were found to have 20 to 40% on average higher exposures compared to other ethnicities including Chinese. However, these differences in exposure are reduced when values are corrected for body weight.

Hemodialysis in ESRD subjects:Systemic exposure to rivaroxaban administered as a single 15 mg dose in ESRD subjects dosed 3 hours after the completion of a 4-hour hemodialysis session (post-dialysis) is 56% higher when compared to subjects with normal renal function (see Table 18). The systemic exposure to rivaroxaban administered 2 hours prior to a 4-hour hemodialysis session with a dialysate flow rate of 600 mL/min and a blood flow rate in the range of 320 to 400 mL/min is 47% higher compared to those with normal renal function. The extent of the increase is similar to the increase in patients with CrCl 15 to 50 mL/min taking XARELTO 15 mg. Hemodialysis had no significant impact on rivaroxaban exposure. Protein binding was similar (86% to 89%) in healthy controls and ESRD subjects in this study.

Pediatric Patients:Limited clinical data are available in children 1 year or older with moderate or severe renal impairment (eGFR <50 mL/min/1.73 m^2) or in children younger than 1 year with serum creatinine results above 97.5th percentile [see Dosage and Administration (2.2)and Use in Specific Populations (8.6)] .

Elderly

The terminal elimination half-life is 11 to 13 hours in the elderly subjects aged 60 to 76 years [see Use in Specific Populations (8.5)] .

Pediatric Patients

The rate and extent of absorption were similar between the tablet and suspension. After repeated administration of rivaroxaban for the treatment of VTE, the Cmaxof rivaroxaban in plasma was observed at median times of 1.5 to 2.2 hours in subjects who ranged from birth to less than 18 years of age.

In children who were 6 months to 9 years of age, in vitroplasma protein binding of rivaroxaban is approximately 90%.

The half-life of rivaroxaban in plasma of pediatric patients treated for VTE decreased with decreasing age. Mean half-life values were 4.2 hours in adolescents, 3 hours in children 2 to 12 years of age, 1.9 hours in children 0.5 to <2 years of age, and 1.6 hours in children <0.5 years of age.

An exploratory analysis in pediatric patients treated for VTE did not reveal relevant differences in rivaroxaban exposure based on gender or race.

Renal Impairment

The safety and pharmacokinetics of single-dose XARELTO (10 mg) were evaluated in a study in healthy subjects [CrCl ≥80 mL/min (n=8)] and in subjects with varying degrees of renal impairment (see Figure 2). Compared to healthy subjects with normal creatinine clearance, rivaroxaban exposure increased in subjects with renal impairment. Increases in pharmacodynamic effects were also observed [see Use in Specific Populations (8.6)] .

Hepatic Impairment

The safety and pharmacokinetics of single-dose XARELTO (10 mg) were evaluated in a study in healthy adult subjects (n=16) and adult subjects with varying degrees of hepatic impairment (see Figure 2). No patients with severe hepatic impairment (Child-Pugh C) were studied. Compared to healthy subjects with normal liver function, significant increases in rivaroxaban exposure were observed in subjects with moderate hepatic impairment (Child-Pugh B) (see Figure 2). Increases in pharmacodynamic effects were also observed [see Use in Specific Populations (8.7)] .

No clinical data are available in pediatric patients with hepatic impairment.

Drug Interactions

In vitrostudies indicate that rivaroxaban neither inhibits the major cytochrome P450 enzymes CYP1A2, 2C8, 2C9, 2C19, 2D6, 2J2, and 3A nor induces CYP1A2, 2B6, 2C19, or 3A. In vitrodata also indicates a low rivaroxaban inhibitory potential for P-gp and ABCG2 transporters.

The effects of coadministered drugs on the pharmacokinetics of rivaroxaban exposure are summarized in Figure 3 [see Drug Interactions (7)] .

Figure 3: Effect of Coadministered Drugs on the Pharmacokinetics of Rivaroxaban in Adults

Anticoagulants

In a drug interaction study, single doses of enoxaparin (40 mg subcutaneous) and XARELTO (10 mg) given concomitantly resulted in an additive effect on anti-factor Xa activity. In another study, single doses of warfarin (15 mg) and XARELTO (5 mg) resulted in an additive effect on factor Xa inhibition and PT. Neither enoxaparin nor warfarin affected the pharmacokinetics of rivaroxaban (see Figure 3).

NSAIDs/Aspirin

In ROCKET AF, concomitant aspirin use (almost exclusively at a dose of 100 mg or less) during the double-blind phase was identified as an independent risk factor for major bleeding. NSAIDs are known to increase bleeding, and bleeding risk may be increased when NSAIDs are used concomitantly with XARELTO. Neither naproxen nor aspirin affected the pharmacokinetics of rivaroxaban (see Figure 3).

Clopidogrel

In two drug interaction studies where clopidogrel (300 mg loading dose followed by 75 mg daily maintenance dose) and XARELTO (15 mg single dose) were coadministered in healthy subjects, an increase in bleeding time to 45 minutes was observed in approximately 45% and 30% of subjects in these studies, respectively. The change in bleeding time was approximately twice the maximum increase seen with either drug alone. There was no change in the pharmacokinetics of either drug.

Drug-Disease Interactions with Drugs that Inhibit Cytochrome P450 3A Enzymes and Drug Transport Systems

In a pharmacokinetic trial, XARELTO was administered as a single dose in subjects with mild (CrCl = 50 to 79 mL/min) or moderate renal impairment (CrCl = 30 to 49 mL/min) receiving multiple doses of erythromycin (a combined P-gp and moderate CYP3A inhibitor). Compared to XARELTO administered alone in subjects with normal renal function (CrCl >80 mL/min), subjects with mild and moderate renal impairment concomitantly receiving erythromycin reported a 76% and 99% increase in AUCinfand a 56% and 64% increase in Cmax, respectively. Similar trends in pharmacodynamic effects were also observed.

12.6 QT/QTc Prolongation

In a thorough QT study in healthy men and women aged 50 years and older, no QTc prolonging effects were observed for XARELTO (15 mg and 45 mg, single-dose).

13 NON-CLINICAL TOXICOLOGY

13.1 Carcinogenesis, Mutagenesis, Impairment of Fertility

Rivaroxaban was not carcinogenic when administered by oral gavage to mice or rats for up to 2 years. The systemic exposures (AUCs) of unbound rivaroxaban in male and female mice at the highest dose tested (60 mg/kg/day) were 1- and 2-times, respectively, the human exposure of unbound drug at the human dose of 20 mg/day. Systemic exposures of unbound drug in male and female rats at the highest dose tested (60 mg/kg/day) were 2- and 4-times, respectively, the human exposure.

Rivaroxaban was not mutagenic in bacteria (Ames-Test) or clastogenic in V79 Chinese hamster lung cells in vitroor in the mouse micronucleus test in vivo.

No impairment of fertility was observed in male or female rats when given up to 200 mg/kg/day of rivaroxaban orally. This dose resulted in exposure levels, based on the unbound AUC, at least 13 times the exposure in humans given 20 mg rivaroxaban daily.

14 CLINICAL STUDIES

14.1 Stroke Prevention in Nonvalvular Atrial Fibrillation

The evidence for the efficacy and safety of XARELTO was derived from Rivaroxaban Once-daily oral direct factor Xa inhibition Compared with vitamin Kantagonist for the prevention of stroke and Embolism Trial in Atrial Fibrillation (ROCKET AF) [NCT00403767], a multi-national, double-blind study comparing XARELTO (at a dose of 20 mg once daily with the evening meal in patients with CrCl >50 mL/min and 15 mg once daily with the evening meal in patients with CrCl 30 to 50 mL/min) to warfarin (titrated to INR 2.0 to 3.0) to reduce the risk of stroke and non-central nervous system (CNS) systemic embolism in patients with nonvalvular atrial fibrillation (AF). Patients had to have one or more of the following additional risk factors for stroke:

- a prior stroke (ischemic or unknown type), transient ischemic attack (TIA) or non-CNS systemic embolism, or
- 2 or more of the following risk factors:
  - age ≥75 years,
  - hypertension,
  - heart failure or left ventricular ejection fraction ≤35%, or
  - diabetes mellitus

ROCKET AF was a non-inferiority study designed to demonstrate that XARELTO preserved more than 50% of warfarin's effect on stroke and non-CNS systemic embolism as established by previous placebo-controlled studies of warfarin in atrial fibrillation.

A total of 14264 patients were randomized and followed on study treatment for a median of 590 days. The mean age was 71 years and the mean CHADS2score was 3.5. The population was 60% male, 83% Caucasian, 13% Asian and 1.3% Black. There was a history of stroke, TIA, or non-CNS systemic embolism in 55% of patients, and 38% of patients had not taken a vitamin K antagonist (VKA) within 6 weeks at time of screening. Concomitant diseases of patients in this study included hypertension 91%, diabetes 40%, congestive heart failure 63%, and prior myocardial infarction 17%. At baseline, 37% of patients were on aspirin (almost exclusively at a dose of 100 mg or less) and few patients were on clopidogrel. Patients were enrolled in Eastern Europe (39%); North America (19%); Asia, Australia, and New Zealand (15%); Western Europe (15%); and Latin America (13%). Patients randomized to warfarin had a mean percentage of time in the INR target range of 2.0 to 3.0 of 55%, lower during the first few months of the study.

In ROCKET AF, XARELTO was demonstrated non-inferior to warfarin for the primary composite endpoint of time to first occurrence of stroke (any type) or non-CNS systemic embolism [HR (95% CI): 0.88 (0.74, 1.03)], but superiority to warfarin was not demonstrated. There is insufficient experience to determine how XARELTO and warfarin compare when warfarin therapy is well-controlled.

Table 19 displays the overall results for the primary composite endpoint and its components.

Table 19: Primary Composite Endpoint Results in ROCKET AF Study (Intent-to-Treat Population)
 | XARELTO |  | Warfarin |  | XARELTO vs. Warfarin
Event | N=7081 n (%) | Event Rate (per 100 Pt-yrs) | N=7090 n (%) | Event Rate (per 100 Pt-yrs) | Hazard Ratio (95% CI)
Primary Composite Endpoint [The primary endpoint was the time to first occurrence of stroke (any type) or non-CNS systemic embolism. Data are shown for all randomized patients followed to site notification that the study would end.] | 269 (3.8) | 2.1 | 306 (4.3) | 2.4 | 0.88 (0.74, 1.03)
Stroke | 253 (3.6) | 2.0 | 281 (4.0) | 2.2
Hemorrhagic Stroke [Defined as primary hemorrhagic strokes confirmed by adjudication in all randomized patients followed up to site notification] | 33 (0.5) | 0.3 | 57 (0.8) | 0.4
Ischemic Stroke | 206 (2.9) | 1.6 | 208 (2.9) | 1.6
Unknown Stroke Type | 19 (0.3) | 0.2 | 18 (0.3) | 0.1
Non-CNS Systemic Embolism | 20 (0.3) | 0.2 | 27 (0.4) | 0.2

Figure 4 is a plot of the time from randomization to the occurrence of the first primary endpoint event in the two treatment arms.

Figure 4: Time to First Occurrence of Stroke (any type) or Non-CNS Systemic Embolism by Treatment Group (Intent-to-Treat Population)

Figure 5 shows the risk of stroke or non-CNS systemic embolism across major subgroups.

Figure 5: Risk of Stroke or Non-CNS Systemic Embolism by Baseline Characteristics in ROCKET AF [Data are shown for all randomized patients followed to site notification that the study would end.] (Intent-to-Treat Population)

Note: The figure above presents effects in various subgroups all of which are baseline characteristics and all of which were pre-specified (diabetic status was not pre-specified in the subgroup, but was a criterion for the CHADS2 score). The 95% confidence limits that are shown do not take into account how many comparisons were made, nor do they reflect the effect of a particular factor after adjustment for all other factors. Apparent homogeneity or heterogeneity among groups should not be over-interpreted.

The efficacy of XARELTO was generally consistent across major subgroups.

The protocol for ROCKET AF did not stipulate anticoagulation after study drug discontinuation, but warfarin patients who completed the study were generally maintained on warfarin. XARELTO patients were generally switched to warfarin without a period of coadministration of warfarin and XARELTO, so that they were not adequately anticoagulated after stopping XARELTO until attaining a therapeutic INR. During the 28 days following the end of the study, there were 22 strokes in the 4637 patients taking XARELTO vs. 6 in the 4691 patients taking warfarin.

Few patients in ROCKET AF underwent electrical cardioversion for atrial fibrillation. The utility of XARELTO for preventing post-cardioversion stroke and systemic embolism is unknown.

14.2 Treatment of Deep Vein Thrombosis (DVT) and/or Pulmonary Embolism (PE)

EINSTEIN Deep Vein Thrombosis and EINSTEIN Pulmonary Embolism Studies

XARELTO for the treatment of DVT and/or PE was studied in EINSTEIN DVT [NCT00440193] and EINSTEIN PE [NCT00439777], multi-national, open-label, non-inferiority studies comparing XARELTO (at an initial dose of 15 mg twice daily with food for the first three weeks, followed by XARELTO 20 mg once daily with food) to enoxaparin 1 mg/kg twice daily for at least five days with VKA and then continued with VKA only after the target INR (2.0–3.0) was reached. Patients who required thrombectomy, insertion of a caval filter, or use of a fibrinolytic agent and patients with creatinine clearance <30 mL/min, significant liver disease, or active bleeding were excluded from the studies. The intended treatment duration was 3, 6, or 12 months based on investigator's assessment prior to randomization.

A total of 8281 (3449 in EINSTEIN DVT and 4832 in EINSTEIN PE) patients were randomized and followed on study treatment for a mean of 208 days in the XARELTO group and 204 days in the enoxaparin/VKA group. The mean age was approximately 57 years. The population was 55% male, 70% Caucasian, 9% Asian and about 3% Black. About 73% and 92% of XARELTO-treated patients in the EINSTEIN DVT and EINSTEIN PE studies, respectively, received initial parenteral anticoagulant treatment for a median duration of 2 days. Enoxaparin/VKA-treated patients in the EINSTEIN DVT and EINSTEIN PE studies received initial parenteral anticoagulant treatment for a median duration of 8 days. Aspirin was taken as on treatment concomitant antithrombotic medication by approximately 12% of patients in both treatment groups. Patients randomized to VKA had an unadjusted mean percentage of time in the INR target range of 2.0 to 3.0 of 58% in EINSTEIN DVT study and 60% in EINSTEIN PE study, with the lower values occurring during the first month of the study.

In the EINSTEIN DVT and EINSTEIN PE studies, 49% of patients had an idiopathic DVT/PE at baseline. Other risk factors included previous episode of DVT/PE (19%), recent surgery or trauma (18%), immobilization (16%), use of estrogen-containing drug (8%), known thrombophilic conditions (6%), or active cancer (5%).

In the EINSTEIN DVT and EINSTEIN PE studies, XARELTO was demonstrated to be non-inferior to enoxaparin/VKA for the primary composite endpoint of time to first occurrence of recurrent DVT or non-fatal or fatal PE [EINSTEIN DVT HR (95% CI): 0.68 (0.44, 1.04); EINSTEIN PE HR (95% CI): 1.12 (0.75, 1.68)]. In each study the conclusion of non-inferiority was based on the upper limit of the 95% confidence interval for the hazard ratio being less than 2.0.

Table 20 displays the overall results for the primary composite endpoint and its components for EINSTEIN DVT and EINSTEIN PE studies.

Table 20: Primary Composite Endpoint Results [For the primary efficacy analysis, all confirmed events were considered from randomization up to the end of intended treatment duration (3, 6 or 12 months) irrespective of the actual treatment duration. If the same patient had several events, the patient may have been counted for several components.] in EINSTEIN DVT and EINSTEIN PE Studies – Intent-to-Treat Population
Event | XARELTO 20 mg [Treatment schedule in EINSTEIN DVT and EINSTEIN PE studies: XARELTO 15 mg twice daily for 3 weeks followed by 20 mg once daily; enoxaparin/VKA [enoxaparin: 1 mg/kg twice daily, VKA: individually titrated doses to achieve a target INR of 2.5 (range: 2.0–3.0)]] | Enoxaparin/VKA | XARELTO vs. Enoxaparin/VKA Hazard Ratio (95% CI)
EINSTEIN DVT Study | N=1731 n (%) | N=1718 n (%)
Primary Composite Endpoint | 36 (2.1) | 51 (3.0) | 0.68 (0.44, 1.04)
Death (PE) | 1 (<0.1) | 0
Death (PE cannot be excluded) | 3 (0.2) | 6 (0.3)
Symptomatic PE and DVT | 1 (<0.1) | 0
Symptomatic recurrent PE only | 20 (1.2) | 18 (1.0)
Symptomatic recurrent DVT only | 14 (0.8) | 28 (1.6)
EINSTEIN PE Study | N=2419 n (%) | N=2413 n (%)
Primary Composite Endpoint | 50 (2.1) | 44 (1.8) | 1.12 (0.75, 1.68)
Death (PE) | 3 (0.1) | 1 (<0.1)
Death (PE cannot be excluded) | 8 (0.3) | 6 (0.2)
Symptomatic PE and DVT | 0 | 2 (<0.1)
Symptomatic recurrent PE only | 23 (1.0) | 20 (0.8)
Symptomatic recurrent DVT only | 18 (0.7) | 17 (0.7)

Figures 6 and 7 are plots of the time from randomization to the occurrence of the first primary efficacy endpoint event in the two treatment groups in EINSTEIN DVT and EINSTEIN PE studies, respectively.

Figure 6: Time to First Occurrence of the Composite of Recurrent DVT or Non-fatal or Fatal PE by Treatment Group (Intent-to-Treat Population) – EINSTEIN DVT Study

Figure 7: Time to First Occurrence of the Composite of Recurrent DVT or Non-fatal or Fatal PE by Treatment Group (Intent-to-Treat Population) – EINSTEIN PE Study

14.3 Reduction in the Risk of Recurrence of DVT and/or PE

EINSTEIN CHOICE Study

XARELTO for reduction in the risk of recurrence of DVT and of PE was evaluated in the EINSTEIN CHOICE study [NCT02064439], a multi-national, double-blind, superiority study comparing XARELTO (10 or 20 mg once daily with food) to 100 mg acetylsalicylic acid (aspirin) once daily in patients who had completed 6 to 12 months of anticoagulant treatment for DVT and/or PE following the acute event. The intended treatment duration in the study was up to 12 months. Patients with an indication for continued therapeutic-dose anticoagulation were excluded.

Because the benefit-risk assessment favored the 10 mg dose versus aspirin compared to the 20 mg dose versus aspirin, only the data concerning the 10 mg dose is discussed below.

A total of 2275 patients were randomized and followed on study treatment for a mean of 290 days for the XARELTO and aspirin treatment groups. The mean age was approximately 59 years. The population was 56% male, 70% Caucasian, 14% Asian and 3% Black. In the EINSTEIN CHOICE study, 51% of patients had DVT only, 33% had PE only, and 16% had PE and DVT combined. Other risk factors included idiopathic VTE (43%), previous episode of DVT/PE (17%), recent surgery or trauma (12%), prolonged immobilization (10%), use of estrogen containing drugs (5%), known thrombophilic conditions (6%), Factor V Leiden gene mutation (4%), or active cancer (3%).

In the EINSTEIN CHOICE study, XARELTO 10 mg was demonstrated to be superior to aspirin 100 mg for the primary composite endpoint of time to first occurrence of recurrent DVT or non-fatal or fatal PE.

Table 21 displays the overall results for the primary composite endpoint and its components.

Table 21: Primary Composite Endpoint and its Components Results [For the primary efficacy analysis, all confirmed events were considered from randomization up to the end of intended treatment duration (12 months) irrespective of the actual treatment duration. The individual component of the primary endpoint represents the first occurrence of the event.] in EINSTEIN CHOICE Study – Full Analysis Set
Event | XARELTO 10 mg N=1,127 n (%) | Acetylsalicylic Acid (Aspirin) 100 mg N=1,131 n (%) | XARELTO 10 mg vs. Aspirin 100 mg Hazard Ratio (95% CI)
Primary Composite Endpoint | 13 (1.2) | 50 (4.4) | 0.26 (0.14, 0.47) p<0.0001
Symptomatic recurrent DVT | 8 (0.7) | 29 (2.6)
Symptomatic recurrent PE | 5 (0.4) | 19 (1.7)
Death (PE) | 0 | 1 (<0.1)
Death (PE cannot be excluded) | 0 | 1 (<0.1)

Figure 8 is a plot of the time from randomization to the occurrence of the first primary efficacy endpoint event in the two treatment groups.

Figure 8: Time to First Occurrence of the Composite of Recurrent DVT or Non-fatal or Fatal PE by Treatment Group (Full Analysis Set) – EINSTEIN CHOICE Study

14.4 Prophylaxis of Deep Vein Thrombosis Following Hip or Knee Replacement Surgery

XARELTO was studied in 9011 patients (4487 XARELTO-treated, 4524 enoxaparin-treated patients) in the REgulation of Coagulation in ORthopedic Surgery to Prevent DVT and PE, Controlled, Double-blind, Randomized Study of BAY 59-7939 in the Extended Prevention of VTE in Patients Undergoing Elective Total Hip or Knee Replacement (RECORD 1, 2, and 3) [NCT00329628, NCT00332020, NCT00361894] studies.

The two randomized, double-blind, clinical studies (RECORD 1 and 2) in patients undergoing elective total hip replacement surgery compared XARELTO 10 mg once daily starting at least 6 to 8 hours (about 90% of patients dosed 6 to 10 hours) after wound closure versus enoxaparin 40 mg once daily started 12 hours preoperatively. In RECORD 1 and 2, a total of 6727 patients were randomized and 6579 received study drug. The mean age [± standard deviation (SD)] was 63 ± 12.2 (range 18 to 93) years with 49% of patients ≥65 years and 55% of patients were female. More than 82% of patients were White, 7% were Asian, and less than 2% were Black. The studies excluded patients undergoing staged bilateral total hip replacement, patients with severe renal impairment defined as an estimated creatinine clearance <30 mL/min, or patients with significant liver disease (hepatitis or cirrhosis). In RECORD 1, the mean exposure duration (± SD) to active XARELTO and enoxaparin was 33.3 ± 7.0 and 33.6 ± 8.3 days, respectively. In RECORD 2, the mean exposure duration to active XARELTO and enoxaparin was 33.5 ± 6.9 and 12.4 ± 2.9 days, respectively. After Day 13, oral placebo was continued in the enoxaparin group for the remainder of the double-blind study duration. The efficacy data for RECORD 1 and 2 are provided in Table 22.

Table 22: Summary of Key Efficacy Analysis Results for Patients Undergoing Total Hip Replacement Surgery - Modified Intent-to-Treat Population
 | RECORD 1 |  |  | RECORD 2
Treatment Dosage and Duration | XARELTO 10 mg once daily | Enoxaparin 40 mg once daily | RRR [Relative Risk Reduction; CI = confidence interval] , p-value | XARELTO 10 mg once daily | Enoxaparin [Includes the placebo-controlled period of RECORD 2] 40 mg once daily | RRR , p-value
Number of Patients | N=1513 | N=1473 |  | N=834 | N=835
Total VTE | 17 (1.1%) | 57 (3.9%) | 71% (95% CI: 50, 83), p<0.001 | 17 (2.0%) | 70 (8.4%) | 76% (95% CI: 59, 86), p<0.001
Components of Total VTE
Proximal DVT | 1 (0.1%) | 31 (2.1%) |  | 5 (0.6%) | 40 (4.8%)
Distal DVT | 12 (0.8%) | 26 (1.8%) |  | 11 (1.3%) | 43 (5.2%)
Non-fatal PE | 3 (0.2%) | 1 (0.1%) |  | 1 (0.1%) | 4 (0.5%)
Death (any cause) | 4 (0.3%) | 4 (0.3%) |  | 2 (0.2%) | 4 (0.5%)
Number of Patients | N=1600 | N=1587 |  | N=928 | N=929
Major VTE [Proximal DVT, nonfatal PE or VTE-related death] | 3 (0.2%) | 33 (2.1%) | 91% (95% CI: 71, 97), p<0.001 | 6 (0.7%) | 45 (4.8%) | 87% (95% CI: 69, 94), p<0.001
Number of Patients | N=2103 | N=2119 |  | N=1178 | N=1179
Symptomatic VTE | 5 (0.2%) | 11 (0.5%) |  | 3 (0.3%) | 15 (1.3%)

One randomized, double-blind, clinical study (RECORD 3) in patients undergoing elective total knee replacement surgery compared XARELTO 10 mg once daily started at least 6 to 8 hours (about 90% of patients dosed 6 to 10 hours) after wound closure versus enoxaparin. In RECORD 3, the enoxaparin regimen was 40 mg once daily started 12 hours preoperatively. The mean age (± SD) of patients in the study was 68 ± 9.0 (range 28 to 91) years with 66% of patients ≥65 years. Sixty-eight percent (68%) of patients were female. Eighty-one percent (81%) of patients were White, less than 7% were Asian, and less than 2% were Black. The study excluded patients with severe renal impairment defined as an estimated creatinine clearance <30 mL/min or patients with significant liver disease (hepatitis or cirrhosis). The mean exposure duration (± SD) to active XARELTO and enoxaparin was 11.9 ± 2.3 and 12.5 ± 3.0 days, respectively. The efficacy data are provided in Table 23.

Table 23: Summary of Key Efficacy Analysis Results for Patients Undergoing Total Knee Replacement Surgery - Modified Intent-to-Treat Population
 | RECORD 3
Treatment Dosage and Duration | XARELTO 10 mg once daily | Enoxaparin 40 mg once daily | RRR [Relative Risk Reduction; CI = confidence interval] , p-value
Number of Patients | N=813 | N=871
Total VTE | 79 (9.7%) | 164 (18.8%) | 48% (95% CI: 34, 60), p<0.001
Components of events contributing to Total VTE
Proximal DVT | 9 (1.1%) | 19 (2.2%)
Distal DVT | 74 (9.1%) | 154 (17.7%)
Non-fatal PE | 0 | 4 (0.5%)
Death (any cause) | 0 | 2 (0.2%)
Number of Patients | N=895 | N=917
Major VTE [Proximal DVT, nonfatal PE or VTE-related death] | 9 (1.0%) | 23 (2.5%) | 60% (95% CI: 14, 81), p = 0.024
Number of Patients | N=1206 | N=1226
Symptomatic VTE | 8 (0.7%) | 24 (2.0%)

14.5 Prophylaxis of Venous Thromboembolism in Acutely Ill Medical Patients at Risk for Thromboembolic Complications Not at High Risk of Bleeding

The efficacy and safety of XARELTO for prophylaxis of venous thromboembolism in acutely ill medical patients at risk for thromboembolic complications not at high risk of bleeding was evaluated in the MAGELLAN study (Multicenter, r Andomized, parallel Group Efficacy and safety study for the prevention of venous thromboembolism in hospitalized medically i LLpatients comparing rivaroxab aNwith enoxaparin [NCT00571649]). MAGELLAN was a multicenter, randomized, double-blind, parallel-group efficacy and safety study comparing XARELTO to enoxaparin, in the prevention of VTE in hospitalized acutely ill medical patients during the in-hospital and post-hospital discharge period. Eligible patients included adults who were at least 40 years of age, hospitalized for an acute medical illness, at risk of VTE due to moderate or severe immobility, and had additional risk factors for VTE. The population at risk of VTE was required to have one or more of the following VTE risk factors, i.e. prolonged immobilization, age ≥75 years, history of cancer, history of VTE, history of heart failure, thrombophilia, acute infectious disease contributing to the hospitalization and BMI ≥35 kg/m^2). The causes for hospitalization included heart failure, active cancer, acute ischemic stroke, acute infectious and inflammatory disease and acute respiratory insufficiency. Patients were randomized to receive either XARELTO 10 mg once daily for 35 ±4 days starting in hospital and continuing post hospital discharge (n=4050) or enoxaparin 40 mg once daily for 10 ±4 days starting in hospital followed by placebo post-discharge (n=4051).

The major efficacy outcome in the MAGELLAN trial was a composite endpoint that included asymptomatic proximal deep venous thrombosis (DVT) in lower extremity, symptomatic proximal or distal DVT in the lower extremity, symptomatic non-fatal pulmonary embolism (PE), and death related to venous thromboembolism (VTE).

A total of 6024 patients were evaluable for the major efficacy outcome analysis (2967 on XARELTO 10 mg once daily and 3057 on enoxaparin/placebo). The mean age was 68.9 years, with 37.1% of the subject population ≥ 75 years. VTE risk factors included severe immobilization at study entry (99.9%), D-dimer > 2× ULN (43.7%), history of heart failure (35.6%), BMI ≥ 35 kg/m^2(15.2%), chronic venous insufficiency (14.9%), acute infectious disease (13.9%), severe varicosis (12.5%), history of cancer (16.2%), history of VTE (4.5%), hormone replacement therapy (1.1%), and thrombophilia (0.3%), recent major surgery (0.8%) and recent serious trauma (0.2%). The population was 54.7% male, 68.2% White, 20.4% Asian, 1.9% Black and 5.3% Other. Admitting diagnoses for hospitalization were acute infectious diseases (43.8%) followed by congestive heart failure NYHA class III or IV (33.2%), acute respiratory insufficiency (26.4%), acute ischemic stroke (18.5%) and acute inflammatory diseases (3.4%).

Table 24 shows the overall results from the prespecified, modified intent-to-treat (mITT) analysis for the efficacy outcomes and their components. This analysis excludes approximately 25% of the patients mainly due to no ultrasonographic assessment (13.5%), inadequate assessment at day 35 (8.1%), or lack of intake of study medication (1.3%).

Table 24: Efficacy Results at Day 35 (modified Intent-to-Treat) and at Day 10 (per protocol) in the MAGELLAN Study
Events from Day 1 to Day 35, mITT analysis set | XARELTO 10 mg N=2967 n (%) | Enoxaparin 40 mg/placebo N=3057 n (%) | RR (95% CI)
Primary Composite Endpoint at Day 35 | 131 (4.4%) | 175 (5.7%) | 0.77 (0.62, 0.96)
Symptomatic non-fatal PE | 10 (0.3) | 14 (0.5)
Symptomatic DVT in lower extremity | 13 (0.4) | 15 (0.5)
Asymptomatic proximal DVT in lower extremity | 103 (3.5) | 133 (4.4)
VTE related death | 19 (0.6) | 30 (1.0)
Events from Day 1 to Day 10, PP analysis set | XARELTO 10 mg N=2938 n (%) | Enoxaparin 40 mg N=2993 n (%) | RR (95% CI)
Primary Composite Endpoint at Day 10 | 78 (2.7) | 82 (2.7) | 0.97 (0.71, 1.31)
Symptomatic non-fatal PE | 6 (0.2) | 2 (<0.1)
Symptomatic DVT in lower extremity | 7 (0.2) | 6 (0.2)
Asymptomatic proximal DVT in lower extremity | 71 (2.4) | 71 (2.4)
VTE related death | 3 (0.1) | 6 (0.2)
mITT analysis set plus all-cause mortality | N=3096 n (%) | N=3169 n (%) | RR (95% CI)
Other Composite Endpoint at Day 35 | 266 (8.6) | 293 (9.2) | 0.93 (0.80, 1.09)
Symptomatic non-fatal PE | 10 (0.3) | 14 (0.4)
Symptomatic DVT in lower extremity | 13 (0.4) | 15 (0.5)
Asymptomatic proximal DVT in lower extremity | 103 (3.3) | 133 (4.2)
All-cause mortality | 159 (5.1) | 153 (4.8)
mITT: modified intent-to-treat; PP: per protocol; DVT: Deep vein thrombosis; PE: pulmonary embolism; VTE: venous thromboembolism; CI: Confidence Interval; RR: Relative Risk

Patients with bronchiectasis/pulmonary cavitation, active cancer, dual antiplatelet therapy or active gastroduodenal ulcer or any bleeding in the previous three months (19.4%) all had an excess of bleeding with XARELTO compared with enoxaparin/placebo. Therefore, patients meeting these criteria were excluded from the following analyses presented below.

Table 25 provides the efficacy results for the subgroup of patients not at a high risk of bleeding.

Table 25: Efficacy Results at Day 35 (modified Intent-to-Treat) and at Day 10 (per protocol) in patients not at a high risk of bleeding in the MAGELLAN Study [Patients at high risk of bleeding (i.e. bronchiectasis/pulmonary cavitation, active cancer, dual antiplatelet therapy or active gastroduodenal ulcer or any bleeding in the previous three months) were excluded.]
Events from Day 1 to Day 35, mITT analysis set | XARELTO 10 mg N=2419 n (%) | Enoxaparin 40 mg/placebo N=2506 n (%) | RR (95% CI)
Primary Composite Endpoint at Day 35 | 94 (3.9) | 143 (5.7) | 0.68 (0.53, 0.88)
Symptomatic non-fatal PE | 7 (0.3) | 10 (0.4)
Symptomatic DVT in lower extremity | 9 (0.4) | 10 (0.4)
Asymptomatic proximal DVT in lower extremity | 73 (3.0) | 110 (4.4)
VTE related death | 15 (0.6) | 26 (1.0)
Events from Day 1 to Day 10, PP analysis set | XARELTO 10 mg N=2385 n (%) | Enoxaparin 40 mg N=2433 n (%) | RR (95% CI)
Primary Composite Endpoint at Day 10 | 58 (2.4) | 72 (3.0) | 0.82 (0.58, 1.15)
Symptomatic non-fatal PE | 5 (0.2) | 2 (<0.1)
Symptomatic DVT in lower extremity | 6 (0.3) | 4 (0.2)
Asymptomatic proximal DVT in lower extremity | 52 (2.2) | 62 (2.5)
VTE related death | 2 (<0.1) | 6 (0.2)
mITT analysis set plus all-cause mortality | N=2504 n (%) | N=2583 n (%) | RR (95% CI)
Other Composite Endpoint at Day 35 | 184 (7.3) | 225 (8.7) | 0.84 (0.70, 1.02)
Symptomatic non-fatal PE | 7 (0.3) | 10 (0.4)
Symptomatic DVT in lower extremity | 9 (0.4) | 10 (0.4)
Asymptomatic proximal DVT in lower extremity | 73 (2.9) | 110 (4.3)
All-cause mortality | 107 (4.3) | 112 (4.3)
mITT: modified intent-to-treat; PP: per protocol; DVT: Deep vein thrombosis; PE: pulmonary embolism; VTE: venous thromboembolism; CI: Confidence Interval; RR: Relative Risk

14.6 Reduction of Risk of Major Cardiovascular Events in Patients with CAD

The evidence for the efficacy and safety of XARELTO for the reduction in the risk of stroke, myocardial infarction, or cardiovascular death in patients with coronary artery disease (CAD) or peripheral artery disease (PAD) was derived from the double-blind, placebo-controlled Cardiovascular Outco Mes for People using Anticoagulation Strategie Strial (COMPASS) [NCT10776424]. A total of 27,395 patients were evenly randomized to rivaroxaban 2.5 mg orally twice daily plus aspirin 100 mg once daily, rivaroxaban 5 mg orally twice daily alone, or aspirin 100 mg once daily alone. Because the 5 mg dose alone was not superior to aspirin alone, only the data concerning the 2.5 mg dose plus aspirin are discussed below.

Patients with established CAD or PAD were eligible. Patients with CAD who were younger than 65 years of age were also required to have documentation of atherosclerosis involving at least two vascular beds or to have at least two additional cardiovascular risk factors (current smoking, diabetes mellitus, an estimated glomerular filtration rate [eGFR] <60 mL per minute, heart failure, or non-lacunar ischemic stroke ≥1 month earlier). Patients with PAD were either symptomatic with ankle brachial index <0.90 or had asymptomatic carotid artery stenosis ≥50%, a previous carotid revascularization procedure, or established ischemic disease of one or both lower extremities. Patients were excluded for use of dual antiplatelet, other non-aspirin antiplatelet, or oral anticoagulant therapies, ischemic, non-lacunar stroke within 1 month, hemorrhagic or lacunar stroke at any time, or eGFR <15 mL/min.

The mean age was 68 years and 21% of the subject population were ≥75 years. Of the included patients, 91% had CAD (and will be referred to as the COMPASS CAD population), 27% had PAD (and will be referred to as the COMPASS PAD population), and 18% had both CAD and PAD. Of the patients with CAD, 69% had prior MI, 60% had prior percutaneous transluminal coronary angioplasty (PTCA)/atherectomy/ percutaneous coronary intervention (PCI), and 26% had history of coronary artery bypass grafting (CABG) prior to study. Of the patients with PAD, 49% had intermittent claudication, 27% had peripheral artery bypass surgery or peripheral percutaneous transluminal angioplasty, 26% had asymptomatic carotid artery stenosis > 50%, and 4% had limb or foot amputation for arterial vascular disease.

The mean duration of follow-up was 23 months. Relative to placebo, XARELTO reduced the rate of the primary composite outcome of stroke, myocardial infarction or cardiovascular death: HR 0.76 (95% CI: 0.66, 0.86; p=0.00004). In the COMPASS CAD population, the benefit was observed early with a constant treatment effect over the entire treatment period (see Table 26and Figure 10).

A benefit-risk analysis of the data from COMPASS was performed by comparing the number of CV events (CV deaths, myocardial infarctions and non-hemorrhagic strokes) prevented to the number of fatal or life-threatening bleeding events (fatal bleeds + symptomatic non-fatal bleeds into a critical organ) in the XARELTO group versus the placebo group. Compared to placebo, during 10,000 patient-years of treatment, XARELTO would be expected to result in 70 fewer CV events and 12 additional life-threatening bleeds, indicating a favorable balance of benefits and risks.

The results in the COMPASS CAD population were consistent across major subgroups (see Figure 9).

Figure 9: Risk of Primary Efficacy Outcome by Baseline Characteristics in the COMPASS CAD Population (Intent-to-Treat Population) [All patients received aspirin 100 mg once daily as background therapy.]

Table 26: Efficacy results from COMPASS CAD Population [intention to treat analysis set, primary analyses.]
Event | XARELTO [Treatment schedule: XARELTO 2.5 mg twice daily vs placebo. All patients received aspirin 100 mg once daily as background therapy.] N=8313 |  | Placebo N=8261 |  | Hazard Ratio (95% CI) [XARELTO vs. placebo.]
Event | n (%) | Event Rate (%/year) | n (%) | Event Rate (%/year) | Hazard Ratio (95% CI) [XARELTO vs. placebo.]
Stroke, MI or CV death | 347 (4.2) | 2.2 | 460 (5.6) | 2.9 | 0.74 (0.65, 0.86)
- Stroke | 74 (0.9) | 0.5 | 130 (1.6) | 0.8 | 0.56 (0.42, 0.75)
- MI | 169 (2.0) | 1.1 | 195 (2.4) | 1.2 | 0.86 (0.70, 1.05)
- CV death | 139 (1.7) | 0.9 | 184 (2.2) | 1.1 | 0.75 (0.60, 0.93)
Coronary heart disease death, MI, ischemic stroke, acute limb ischemia | 299 (3.6) | 1.9 | 411 (5.0) | 2.6 | 0.72 (0.62, 0.83)
- Coronary heart disease death [Coronary heart disease death: death due to acute MI, sudden cardiac death, or CV procedure.] | 80 (1.0) | 0.5 | 107 (1.3) | 0.7 | 0.74 (0.55, 0.99)
- Ischemic stroke | 56 (0.7) | 0.3 | 114 (1.4) | 0.7 | 0.49 (0.35, 0.67)
- Acute limb ischemia [Acute limb ischemia is defined as limb-threatening ischemia leading to an acute vascular intervention (i.e., pharmacologic, peripheral arterial surgery/reconstruction, peripheral angioplasty/stent, or amputation).] | 13 (0.2) | 0.1 | 27 (0.3) | 0.2 | 0.48 (0.25, 0.93)
CV death, [CV death includes CHD death, or death due to other CV causes or unknown death.] MI, ischemic stroke, acute limb ischemia | 349 (4.2) | 2.2 | 470 (5.7) | 3.0 | 0.73 (0.64, 0.84)
All-cause mortality | 262 (3.2) | 1.6 | 339 (4.1) | 2.1 | 0.77 (0.65, 0.90)
CHD: coronary heart disease, CI: confidence interval; CV: cardiovascular; MI: myocardial infarction

Figure 10: Time to First Occurrence of Primary Efficacy Outcome (Stroke, Myocardial Infarction, Cardiovascular Death) in the COMPASS CAD Population [All patients received aspirin 100 mg once daily as background therapy.]

CI: confidence interval

14.7 Reduction of Risk of Major Thrombotic Vascular Events in Patients with PAD, Including Patients after Lower Extremity Revascularization due to Symptomatic PAD

The efficacy and safety of XARELTO 2.5 mg orally twice daily versus placebo on a background of aspirin 100 mg once daily in patients with PAD were evaluated in the COMPASS study (n=4996) and will be referred to as the COMPASS PAD population [see Clinical Studies (14.6)] .

The efficacy and safety of XARELTO were also evaluated for the reduction in the risk of the composite endpoint of myocardial infarction, ischemic stroke, cardiovascular death, acute limb ischemia (ALI), and major amputation of a vascular etiology in patients undergoing a lower extremity infrainguinal revascularization procedure due to symptomatic peripheral artery disease (PAD) in the double-blinded, placebo-controlled Vascular Outcomes stud Yof ASA alon Gwith rivaroxaban in Endovascular or surgical limb Revascularization for peripheral artery disease (PAD) trial (VOYAGER) [NCT02504216]. A total of 6,564 patients were equally randomized to XARELTO 2.5 mg orally twice daily vs placebo on a background therapy of aspirin 100 mg once daily.

Eligible patients included adults who were at least 50 years of age with documented moderate to severe symptomatic lower extremity atherosclerotic PAD who had a successful peripheral surgical procedure and/or endovascular procedure with or without clopidogrel (up to a maximum of 6 months was allowed; median duration of therapy was 31 days). Patients had either a prior history of limb revascularization with ankle brachial index ≤0.85 or no prior history of limb revascularization with ankle brachial index ≤0.80. Patients in need of dual antiplatelet for >6 months, or any additional antiplatelet other than aspirin and clopidogrel, or oral anticoagulant, as well as patients with a history of intracranial hemorrhage, stroke, or transient ischemic attack (TIA), or patients with eGFR <15 mL/min were excluded.

The mean age was 67 years and 20% of the subject population was ≥75 years. Of the included patients, 35% had surgical revascularization, 47% had endovascular revascularization with clopidogrel, and 18% endovascular revascularization without clopidogrel. The median duration of follow-up was 30.8 months.

XARELTO 2.5 mg twice daily was superior to placebo in reducing the rate of the primary composite outcome of myocardial infarction, ischemic stroke, cardiovascular death, acute limb ischemia (ALI), and major amputation of a vascular etiology. The primary efficacy outcome and its components are provided in Table 27. The Kaplan-Meier plot for the primary efficacy outcome can be seen in Figure 11. The secondary efficacy outcomes were tested for superiority in a prespecified, hierarchical order and the first five of seven endpoints were significantly reduced in the rivaroxaban treatment arm (see Table 27). Compared to placebo during 10,000 patient-years of treatment, XARELTO would be expected to result in 181 fewer primary outcome events and 29 more TIMI major bleeding events, indicating a favorable balance of benefits and risks.

Figure 11: Time to First Occurrence of Primary Efficacy Outcome (Myocardial Infarction, Ischemic Stroke, Cardiovascular Death, Acute Limb Ischemia, Major Amputation due to Vascular Origins) in VOYAGER [All patients received aspirin 100 mg once daily as background therapy.]

Figure 12 shows the risk of primary efficacy outcome across major subgroups. Subgroup analyses must be interpreted cautiously, as differences can reflect the play of chance among a large number of analyses. The primary efficacy endpoint generally shows homogeneous results across subgroups.

Figure 12: Risk of Primary Efficacy Outcome by Baseline Characteristics in VOYAGER (Intent-to-Treat Population) [All patients received aspirin 100 mg once daily as background therapy.]

Table 27 provides the efficacy event rates for the prespecified endpoints in VOYAGER and similar endpoints in the COMPASS PAD population.

Table 27: Efficacy Results in VOYAGER (Intent-to-Treat Population) and COMPASS PAD
 | VOYAGER |  |  | COMPASS PAD
 | XARELTO N=3286 | Placebo N=3278 | Hazard Ratio (95% CI) [XARELTO vs. placebo.] p-value [Two-sided p-values] | XARELTO N=2492 | Placebo N=2504 | Hazard Ratio (95% CI)
Outcome Components | Event Rate (%/year) |  | Hazard Ratio (95% CI) [XARELTO vs. placebo.] p-value [Two-sided p-values] | Event Rate (%/year) |  | Hazard Ratio (95% CI)
5-Component Outcome (Major thrombotic vascular events) [Major thrombotic vascular event is the composite of MI, ischemic stroke, CV death, ALI, and major amputation of a vascular etiology.] | 6.8 | 8.0 | 0.85 (0.76, 0.96) p=0.0085 | 3.4 | 4.8 | 0.71 (0.57, 0.87)
MI | 1.7 | 1.9 | 0.88 (0.70, 1.12) | 1.1 | 1.5 | 0.76 (0.53, 1.09)
Ischemic Stroke [Ischemic stroke for VOYAGER included stroke of uncertain/unknown etiology whereas COMPASS only included ischemic stroke.] | 0.9 | 1.0 | 0.87 (0.63, 1.19) | 0.5 | 0.9 | 0.55 (0.33, 0.93)
CV death [CV death includes Coronary Heart Disease death, or death due to other CV causes or sudden cardiac arrest and unknown death.] | 2.5 | 2.2 | 1.14 (0.93, 1.40) | 1.4 | 1.7 | 0.82 (0.59, 1.14)
ALI | 2.0 | 3.0 | 0.67 (0.55, 0.82) | 0.4 | 0.8 | 0.56 (0.32, 0.99)
Major amputation of a vascular etiology [Adjudicated events in VOYAGER and investigator reported events in COMPASS] | 1.3 | 1.5 | 0.89 (0.68, 1.16) | 0.2 | 0.6 | 0.40 (0.20, 0.79)
VOYAGER Secondary Efficacy Outcomes [Secondary outcomes for VOYAGER were tested sequentially.]
MI, ischemic stroke, CHD death, [CHD death includes death due to sudden cardiac death, MI, or coronary revascularization procedure] ALI, and major amputation due to vascular etiology | 5.8 | 7.3 | 0.80 (0.71, 0.91) p=0.0008 | 2.8 | 4.2 | 0.66 (0.53, 0.83)
Unplanned index limb revascularization for recurrent limb ischemia [Unplanned index limb revascularization for recurrent limb ischemia was not captured in COMPASS study.] | 8.4 | 9.5 | 0.88 (0.79, 0.99) p=0.028 | N/A | N/A | N/A
Hospitalization for a coronary or peripheral cause of a thrombotic nature | 3.5 | 4.8 | 0.72 (0.62, 0.85) p<0.0001 | 1.7 | 2.9 | 0.58 (0.44, 0.77)
MI, ischemic stroke, all-cause mortality, ALI, and major amputation due to vascular etiology | 8.2 | 9.3 | 0.89 (0.79, 0.99) p=0.029 | 4.8 | 6.0 | 0.80 (0.67, 0.96)
MI, all-cause stroke, CV death, ALI, and major amputation due to vascular etiology | 6.9 | 8.1 | 0.86 (0.76, 0.96) p=0.010 | 3.4 | 4.9 | 0.70 (0.57, 0.86)
All-cause mortality | 4.0 | 3.7 | 1.08 (0.92, 1.27) | 2.8 | 3.1 | 0.91 (0.72, 1.16)
VTE events [Investigator reported in VOYAGER and adjudicated events in COMPASS] | 0.3 | 0.5 | 0.61 (0.37, 1.00) | 0.2 | 0.3 | 0.67 (0.30, 1.49)
Efficacy endpoints in COMPASS PAD were analysed according to the pre-specified endpoints in VOYAGER when applicable.
ALI=acute limb ischemia, CHD=coronary heart disease; CI=confidence interval, CV=cardiovascular; MI=myocardial infarction, VTE=venous thromboembolism.

14.8 Treatment of Venous Thromboembolism and Reduction in Risk of Recurrent Venous Thromboembolism in Pediatric Patients

XARELTO for the treatment of venous thromboembolism (VTE) and reduction in the risk of recurrent VTE was evaluated in the EINSTEIN Junior Phase 3 study [NCT02234843], a multicenter, open-label, active-controlled, randomized study in 500 pediatric patients from birth to less than 18 years with confirmed VTE. There were 276 children aged 12 to <18 years, 101 children aged 6 to <12 years, 69 children aged 2 to <6 years, and 54 children aged <2 years. Patients <6 months of age were excluded from enrollment if they were <37 weeks of gestation at birth, or had <10 days of oral feeding, or had a body weight of <2.6 kg.

Index VTE was classified as either central venous catheter-related VTE (CVC-VTE), cerebral vein and sinus thrombosis (CVST), and all other VTE including DVT and PE (non-CVC-VTE).

Patients received initial treatment with therapeutic dosages of unfractionated heparin (UFH), low molecular weight heparin (LMWH), or fondaparinux for at least 5 days, and were randomized 2:1 to receive either body weight-adjusted doses of XARELTO (exposures to match that of 20 mg daily dose in adults) or comparator group (UFH, LMWH, fondaparinux or VKA) for a main study treatment period of 3 months (or 1 month for children <2 years with CVC-VTE). A diagnostic imaging test was obtained at baseline and at the end of the main study treatment. When clinically necessary, treatment was extended up to 12 months in total (or up to 3 months in total for children <2 years with CVC-VTE).

Table 28 displays the primary and secondary efficacy results.

Table 28: Efficacy Results in EINSTEIN Junior Study – Full Analysis Set
Event | XARELTO [Treatment schedule: body weight-adjusted doses of XARELTO (exposures to match that of 20 mg daily dose in adults); randomized 2:1 (XARELTO: Comparator).] N=335 n (%) (95% CI) [Confidence intervals for incidence proportion were calculated by applying the method of Blyth-Still-Casella.] | Comparator Group [Unfractionated heparin (UFH), low molecular weight heparin (LMWH), fondaparinux or VKA.] N=165 n (%) (95% CI) | XARELTO vs. Comparator Group Risk Difference (95% CI) [Confidence intervals for difference in incidence proportions were calculated by unstratified exact method according to Agresti-Min using the standardized test statistic and inverting a two-sided test.] | XARELTO vs. Comparator Group Hazard Ratio (95% CI)
Primary efficacy outcome: Symptomatic recurrent VTE | 4 (1.2) (0.4%, 3.0%) | 5 (3.0) (1.2%, 6.6%) | -1.8% (-6.0%, 0.6%) | 0.40 (0.11, 1.41)
Secondary efficacy outcome: Symptomatic recurrent VTE or asymptomatic deterioration on repeat imaging | 5 (1.5) (0.6%, 3.4%) | 6 (3.6) (1.6%, 7.6%) | -2.1% (-6.5%, 0.6%)

Complete resolution of thrombus on repeat imaging without recurrent VTE occurred in 128 of 335 children (38.2%, 95% CI 33.0%, 43.5%) in the XARELTO group and 43 of 165 children (26.1%, 95% CI 19.8%, 33.0%) in the comparator group. Symptomatic recurrent VTE or major bleeding events occurred in 4 of 335 children (1.2%, 95% CI 0.4%, 3.0%) in the XARELTO group and 7 of 165 children (4.2%, 95% CI 2.0%, 8.4%) in the comparator group.

14.9 Thromboprophylaxis in Pediatric Patients with Congenital Heart Disease after the Fontan Procedure

The efficacy and safety of XARELTO for thromboprophylaxis in pediatric patients with congenital heart disease who have undergone the Fontan procedure was evaluated in the UNIVERSE Phase 3 study [NCT02846532]. UNIVERSE was a prospective, open-label, active controlled, multicenter, 2-part study, designed to evaluate the single- and multiple-dose pharmacokinetic properties of XARELTO (Part A), and to evaluate the safety and efficacy of XARELTO when used for thromboprophylaxis for 12 months compared with aspirin (Part B) in children 2 to 8 years of age with single ventricle physiology who had the Fontan procedure. Patients in Part B were randomized 2:1 to receive either body weight-adjusted doses of XARELTO (exposures to match that of 10 mg daily dose in adults) or aspirin (approximately 5 mg/kg). Patients with eGFR <30 ml/min/1.73 m^2were excluded.

The median time between Fontan procedure and the first dose of XARELTO was 4 (range: 2–61) days in Part A and 34 (range: 2–124) days in part B. In comparison, the median time to initiating aspirin was 24 (range 2–117) days.

Table 29 displays the primary efficacy results.

Table 29: Efficacy Results in UNIVERSE Study – Full Analysis Set
 | Part A [Part A: single arm; not randomized] | Part B [Part B: randomized 2:1 (XARELTO: Aspirin)]
Event | XARELTO N=12 n (%) (95% CI) [Confidence intervals for incidence proportion were calculated by applying the method of Blyth-Still-Casella.] | XARELTO [Treatment schedule: body weight-adjusted doses of XARELTO (exposures to match that of 10 mg daily dose in adults) or aspirin (approximately 5 mg/kg)] N=64 n (%) (95% CI) | Aspirin N=34 n (%) (95% CI) | XARELTO vs. Aspirin Risk Difference (95% CI) [Confidence intervals for difference in incidence proportions were calculated by unstratified exact method according to Agresti-Min using the standardized test statistic and inverting a two-sided test.]
Primary efficacy outcome: any thrombotic event | 1 (8.3) (0.4%, 34.9%) | 1 (1.6) (0.1%, 7.8%) | 3 (8.8) (2.4%, 22.2%) | -7.3% (-21.7%, 1.1%)
Ischemic stroke | 0 (0.0%, 23.6%) | 0 (0.0%, 5.6%) | 1 (2.9) 0.2%, 15.1%) | -2.9% (-16.2%, 2.9%)
Pulmonary embolism | 0 (0.0%, 23.6%) | 1 (1.6) (0.1%, 7.8%) | 0 (0.0%, 9.0%) | 1.6% (-9.9%, 8.4%)
Venous thrombosis | 1 (8.3) (0.4%, 34.9%) | 0 (0.0%, 5.6%) | 2 (5.9) (1.1%, 18.8%) | -5.9% (-20.6%, -0.1%)

16 HOW SUPPLIED/STORAGE AND HANDLING

XARELTO®(rivaroxaban) Tablets are available in the strengths and packages listed below:

- 2.5 mg tablets are round, light yellow, and film-coated with a triangle pointing down above a "2.5" marked on one side and "Xa" on the other side. The tablets are supplied in the packages listed:
  NDC 50458-577-60 | Bottle containing 60 tablets
  NDC 50458-577-18 | Bottle containing 180 tablets
  NDC 50458-577-10 | Blister package containing 100 tablets (10 blister cards containing 10 tablets each)
- 10 mg tablets are round, light red, biconvex film-coated tablets marked with a triangle pointing down above a "10" on one side, and "Xa" on the other side. The tablets are supplied in the packages listed:
  NDC 50458-580-30 | Bottle containing 30 tablets
  NDC 50458-580-90 | Bottle containing 90 tablets
  NDC 50458-580-10 | Blister package containing 100 tablets (10 blister cards containing 10 tablets each)
- 15 mg tablets are round, red, biconvex film-coated tablets with a triangle pointing down above a "15" marked on one side and "Xa" on the other side. The tablets are supplied in the packages listed:
  NDC 50458-578-30 | Bottle containing 30 tablets
  NDC 50458-578-90 | Bottle containing 90 tablets
  NDC 50458-578-10 | Blister package containing 100 tablets (10 blister cards containing 10 tablets each)
- 20 mg tablets are triangle-shaped, dark red film-coated tablets with a triangle pointing down above a "20" marked on one side and "Xa" on the other side. The tablets are supplied in the packages listed:
  NDC 50458-579-30 | Bottle containing 30 tablets
  NDC 50458-579-90 | Bottle containing 90 tablets
  NDC 50458-579-89 | Bulk bottle containing 1000 tablets
  NDC 50458-579-10 | Blister package containing 100 tablets (10 blister cards containing 10 tablets each)
- Starter Pack for treatment of deep vein thrombosis and treatment of pulmonary embolism:
  NDC 50458-584-51 | 30-day starter blister pack containing 51 tablets: 42 tablets of 15 mg and 9 tablets of 20 mg

XARELTO®(rivaroxaban) for oral suspension is available in the strength and package listed below:

NDC 50458-575-01 | Supplied as white to off-white granules in an amber glass bottle containing 155 mg rivaroxaban packaged with two oral dosing syringes. After reconstitution with 150 mL of purified water, 1 mL of the suspension contains 1 mg rivaroxaban.

STORAGE AND HANDLING

Discard reconstituted suspension after "Discard after" date written on the bottle.

Storage of tablets, granules and reconstituted suspension:

Store at room temperature between 20 °C to 25 °C (68 °F to 77 °F); excursions permitted between 15 °C to 30 °C (59 °F to 86 °F) [see USP Controlled Room Temperature].

Do not freeze the granules or reconstituted suspension.

Keep out of the reach of children.

17 PATIENT COUNSELING INFORMATION

For the tablets, advise the patient and/or caregiver to read the FDA-approved patient labeling (Medication Guide).

For the suspension, advise the patient and/or caregiver to read the FDA-approved patient labeling (Medication Guide and Instructions for Use).

Instructions for Patient Use

- Advise patients to take XARELTO only as directed.
- Remind patients to not discontinue XARELTO without first talking to their healthcare professional.

Adults

- Advise patients with atrial fibrillation to take XARELTO once daily with the evening meal.
- Advise patients for initial treatment of DVT and/or PE to take XARELTO 15 mg or 20 mg tablets with food at approximately the same time every day [see Dosage and Administration (2.1)] .
- Advise patients who are at a continued risk of recurrent DVT and/or PE after at least 6 months of initial treatment, to take XARELTO 10 mg once daily with or without food [see Dosage and Administration (2.1)].
- Advise patients who cannot swallow the tablet whole to crush XARELTO and combine with a small amount of applesauce followed by food [see Dosage and Administration (2.6)] .
- For patients requiring an NG tube or gastric feeding tube, instruct the patient or caregiver to crush the XARELTO tablet and mix it with a small amount of water before administering via the tube [see Dosage and Administration (2.6)] .
- If a dose is missed, advise the patient according to the instructions in the Full Prescribing Information based on their dosing schedule [see Dosage and Administration (2.5)] .

Pediatric Patients

- The adult caregiver should administer the dose. Advise caregivers to use the syringes provided in the original carton.
- Advise the caregiver whether the dose needs to be taken with food or not [see Dosage and Administration (2.2)] .
- Advise the caregiver the tablet must not be split in an attempt to provide a fraction of a tablet dose [see Dosage and Administration (2.2)] .
- If a child vomits or spits up the dose within 30 minutes after receiving the dose, a new dose should be given. However, if the child vomits more than 30 minutes after the dose is taken, the dose should not be re-administered and the next dose should be taken as scheduled. If a child vomits or spits up the dose repeatedly, the caregiver should contact the child's doctor right away [see Dosage and Administration (2.2)] .
- For children who are unable to swallow whole tablets, XARELTO oral suspension may be used.
- If a dose is missed, advise the patient according to the instructions in the Full Prescribing Information based on their dosing schedule [see Dosage and Administration (2.5)] .

Bleeding Risks

- Advise patients to report any unusual bleeding or bruising to their physician. Inform patients that it might take them longer than usual to stop bleeding, and that they may bruise and/or bleed more easily when they are treated with XARELTO [see Warnings and Precautions (5.2)] .
- If patients have had neuraxial anesthesia or spinal puncture, and particularly, if they are taking concomitant NSAIDs or platelet inhibitors, advise patients to watch for signs and symptoms of spinal or epidural hematoma, such as back pain, tingling, numbness (especially in the lower limbs), muscle weakness, and stool or urine incontinence. If any of these symptoms occur, advise the patient to contact his or her physician immediately [see Boxed Warning] .

Invasive or Surgical Procedures

Instruct patients to inform their healthcare professional that they are taking XARELTO before any invasive procedure (including dental procedures) is scheduled.

Concomitant Medication and Herbals

Advise patients to inform their physicians and dentists if they are taking, or plan to take, any prescription or over-the-counter drugs or herbals, so their healthcare professionals can evaluate potential interactions [see Drug Interactions (7)] .

Pregnancy and Pregnancy-Related Hemorrhage

- Advise patients to inform their physician immediately if they become pregnant or intend to become pregnant during treatment with XARELTO [see Use in Specific Populations (8.1)] .
- Advise pregnant women receiving XARELTO to immediately report to their physician any bleeding or symptoms of blood loss [see Warnings and Precautions (5.7)] .

Lactation

Advise patients to discuss with their physician the benefits and risks of XARELTO for the mother and for the child if they are nursing or intend to nurse during anticoagulant treatment [see Use in Specific Populations (8.2)] .

Females and Males of Reproductive Potential

Advise patients who can become pregnant to discuss pregnancy planning with their physician [see Use in Specific Populations (8.3)] .

Manufactured for:
Janssen Pharmaceuticals, Inc.
Titusville, NJ 08560, USA

Licensed from:
Bayer HealthCare AG
51368 Leverkusen, Germany

For patent information: www.janssenpatents.com

© Johnson & Johnson and its affiliates 2011-2021, 2025

MEDICATION GUIDE

XARELTO®(zah-REL-toe)
(rivaroxaban)
tablets

XARELTO®(zah-REL-toe)
(rivaroxaban)
oral suspension

What is the most important information I should know about XARELTO?
XARELTO may cause serious side effects, including:

- Increased risk of blood clots if you stop taking XARELTO.People with atrial fibrillation (a type of irregular heart beat) that is not caused by a heart valve problem (non-valvular) are at an increased risk of forming a blood clot in the heart, which can travel to the brain, causing a stroke, or to other parts of the body. XARELTO lowers your chance of having a stroke by helping to prevent clots from forming. If you stop taking XARELTO, you may have increased risk of forming a clot in your blood.
  Do not stop taking XARELTO without talking to the doctor who prescribes it for you. Stopping XARELTO increases your risk of having a stroke.If you have to stop taking XARELTO, your doctor may prescribe another blood thinner medicine to prevent a blood clot from forming.
- Increased risk of bleeding.XARELTO can cause bleeding which can be serious and may lead to death. This is because XARELTO is a blood thinner medicine (anticoagulant) that lowers blood clotting. During treatment with XARELTO you are likely to bruise more easily, and it may take longer for bleeding to stop. You may have a higher risk of bleeding if you take XARELTO and have certain other medical problems.
  You may have a higher risk of bleeding if you take XARELTO and take other medicines that increase your risk of bleeding, including:
  - aspirin or aspirin containing products
  - long-term (chronic) use of non-steroidal anti-inflammatory drugs (NSAIDs)
  - warfarin sodium (Coumadin®, Jantoven®)
  - any medicine that contains heparin
  - clopidogrel (Plavix®)
  - selective serotonin reuptake inhibitors (SSRIs) or serotonin norepinephrine reuptake inhibitors (SNRIs)
  - other medicines to prevent or treat blood clots
  Tell your doctorif you take any of these medicines. Ask your doctor or pharmacist if you are not sure if your medicine is one listed above.
  Call your doctor or get medical help right away if you or your child develop any of these signs or symptoms of bleeding:
  - unexpected bleeding or bleeding that lasts a long time, such as:
    - nose bleeds that happen often
    - unusual bleeding from the gums
    - menstrual bleeding that is heavier than normal or vaginal bleeding
  - bleeding that is severe or you cannot control
  - red, pink or brown urine
  - bright red or black stools (looks like tar)
  - cough up blood or blood clots
  - vomit blood or your vomit looks like "coffee grounds"
  - headaches, feeling dizzy or weak
  - pain, swelling, or new drainage at wound sites
  - left upper belly (abdominal) pain, pain below the left rib cage or at the tip of your left shoulder or diffuse abdominal discomfort (these may be symptoms of rupture of the spleen)
- Spinal or epidural blood clots (hematoma).People who take a blood thinner medicine (anticoagulant) like XARELTO, and have medicine injected into their spinal and epidural area, or have a spinal puncture have a risk of forming a blood clot that can cause long-term or permanent loss of the ability to move (paralysis). Your risk of developing a spinal or epidural blood clot is higher if:
  - a thin tube called an epidural catheter is placed in your back to give you certain medicine
  - you take NSAIDs or a medicine to prevent blood from clotting
  - you have a history of difficult or repeated epidural or spinal punctures
  - you have a history of problems with your spine or have had surgery on your spine
  If you take XARELTO and receive spinal anesthesia or have a spinal puncture, your doctor should watch you closely for symptoms of spinal or epidural blood clots.
  Tell your doctorright away if you have:

- back pain
- tingling
- numbness

- muscle weakness (especially in your legs and feet)
- loss of control of the bowels or bladder (incontinence)

XARELTO is not for use in people with artificial heart valves.
XARELTO is not for use in people with antiphospholipid syndrome (APS), especially with positive triple antibody testing.

What is XARELTO?
XARELTO is a prescription medicine used to:

- reduce the risk of stroke and blood clots in adults who have a medical condition called atrial fibrillation that is not caused by a heart valve problem. With atrial fibrillation, part of the heart does not beat the way it should. This can lead to the formation of blood clots, which can travel to the brain, causing a stroke, or to other parts of the body.
- treat blood clots in the veins of your legs (deep vein thrombosis or DVT) or lungs (pulmonary embolism or PE)
- reduce the risk of blood clots from happening again in adults who continue to be at risk for DVT or PE after receiving treatment for blood clots for at least 6 months.
- help prevent a blood clot in the legs and lungs of adults who have just had hip or knee replacement surgery.
- help prevent blood clots in certain adults hospitalized for an acute illness and after discharge who are at risk of getting blood clots because of the loss of or decreased ability to move around (mobility) and other risks for getting blood clots and who do not have a high risk of bleeding.

XARELTO is used with low dose aspirin to:

- reduce the risk of serious heart problems, heart attack and stroke in adults with coronary artery disease (a condition where the blood supply to the heart is reduced or blocked).
- reduce the risk of a sudden decrease in blood flow to the legs, major amputation, serious heart problems or stroke in adults with peripheral artery disease (a condition where the blood flow to the legs is reduced) and includes adults who have recently had a procedure to improve blood flow to the legs.

XARELTO is used in children to:

- treat blood clots or reduce the risk of blood clots from happening again in children from birth to less than 18 years, after receiving at least 5 days of treatment with injectable or intravenous medicines used to treat blood clots.
- help prevent blood clots in children 2 years and older with congenital heart disease after the Fontan procedure.

XARELTO was not studied and is not recommended in children less than 6 months of age who:

- were less than 37 weeks of growth (gestation) at birth
- had less than 10 days of oral feeding, or
- had a body weight of less than 5.7 pounds (2.6 kg)

Do not take XARELTO if you or your child:

- currently have certain types of abnormal bleeding. Talk to your doctor before taking XARELTO if you currently have unusual bleeding.
- are allergic to rivaroxaban or any of the ingredients in XARELTO. See the end of this Medication Guide for a complete list of ingredients in XARELTO.

Before taking XARELTO, tell your doctor about all of your medical conditions, including if you or your child:

- have or ever had bleeding problems
- have liver or kidney problems
- have antiphospholipid syndrome (APS)
- are pregnant or plan to become pregnant. It is not known if XARELTO will harm your unborn baby.
  - Tell your doctorright away if you become pregnant during treatment with XARELTO. Taking XARELTO while you are pregnant may increase the risk of bleeding in you or in your unborn baby.
  - Females who are able to become pregnant: Talk with your doctor about pregnancy planning during treatment with XARELTO. Talk with your doctor about your risk for severe uterine bleeding if you are treated with blood thinner medicines, including XARELTO.
  - If you take XARELTO during pregnancy tell your doctorright away if you have any signs or symptoms of bleeding or blood loss. See " What is the most important information I should know about XARELTO?" for signs and symptoms of bleeding.
- are breastfeeding or plan to breastfeed. XARELTO can pass into your breast milk. Talk to your doctor about the best way to feed your baby during treatment with XARELTO.

Tell all of your doctors and dentiststhat you or your child are taking XARELTO. They should talk to the doctor who prescribed XARELTO for you before you have any surgery, medical or dental procedure.
Tell your doctor about all the medicines you or your child take,including prescription and over-the-counter medicines, vitamins, and herbal supplements.
Some of your other medicines may affect the way XARELTO works, causing side effects. Certain medicines may increase your risk of bleeding. See " What is the most important information I should know about XARELTO?"
Especially tell your doctor if you or your child take:

- ketoconazole
- erythromycin
- phenytoin
- St. John's wort

- ritonavir
- carbamazepine
- rifampin

How should I take XARELTO?

- Take XARELTO exactly as prescribed by your doctor.
- Do not change your dose or stop taking XARELTO unless your doctor tells you to.Your doctor may change your dose if needed.
- Your doctor will decide how long you should take XARELTO.
- XARELTO may need to be stopped for one or more days before any surgery or medical or dental procedure. Your doctor will tell you when to stop taking XARELTO and when to start taking XARELTO again after your surgery or procedure.
- If you need to stop taking XARELTO for any reason, talk to the doctor who prescribed XARELTO to you to find out when you should stop taking it. Do not stop taking XARELTO without first talking to the doctor who prescribes it to you.
- If you have difficulty swallowing XARELTO tablets whole, talk to your doctor about other ways to take XARELTO.
- Do not run out of XARELTO. Refill your prescription of XARELTO before you run out. When leaving the hospital following a hip or knee replacement, be sure that you will have XARELTO available to avoid missing any doses.
- If you take too much XARELTO, go to the nearest hospital emergency room or call your doctor right away.

If you take XARELTO for:

- Atrial fibrillation that is not caused by a heart valve problem:
  - Take XARELTO 1 time a day with your evening meal.
  - If you miss a dose of XARELTO, take it as soon as you remember on the same day. Take your next dose at your regularly scheduled time.
- Blood clots in the veins of your legs or lungs:
  - Take XARELTO 1 or 2 times a dayas prescribed by your doctor.
  - For the 10 mg dose, take XARELTO with or without food.
  - For the 15 mg and 20 mg doses, take XARELTO with food at the same time each day.
  - If you miss a dose:
    - If you take the 15 mg dose of XARELTO 2 times a day (a total of 30 mg of XARELTO in 1 day): Take XARELTO as soon as you remember on the same day. You may take 2 doses at the same time to make up for the missed dose. Take your next dose at your regularly scheduled time.
    - If you take XARELTO 1 time a day:Take XARELTO as soon as you remember on the same day. Take your next dose at your regularly scheduled time.
- Hip or knee replacement surgery:
  - Take XARELTO 1 time a day with or without food.
  - If you miss a dose of XARELTO, take it as soon as you remember on the same day. Take your next dose at your regularly scheduled time.
- Blood clots in people hospitalized for an acute illness:
  - Take XARELTO 1 time a day, with or without food, while you are in the hospital and after you are discharged as prescribed by your doctor.
  - If you miss a dose of XARELTO, take it as soon as you remember on the same day. Take your next dose at your regularly scheduled time.
- Reducing the risk of serious heart problems, heart attack and stroke in coronary artery disease:
  - Take XARELTO 2.5 mg 2 times a day with or without food.
  - If you miss a dose of XARELTO, take your next dose at your regularly scheduled time.
  - Take aspirin 75 to 100 mg once daily as instructed by your doctor.
- Reducing the risk of a sudden decrease in blood flow to the legs, major amputation, serious heart problems or stroke in people with peripheral artery disease including those who have recently had a procedure to improve blood flow to the legs:
  - Take XARELTO 2.5 mg 2 times a day with or without food.
  - If you miss a dose of XARELTO, take your next dose at your regularly scheduled time.
  - Take aspirin 75 mg to 100 mg 1 time a day as instructed by your doctor.

For children who take XARELTO:

- The dose of XARELTO depends on your child's body weight and will be calculated by your child's doctor. Your child's doctor will tell you if XARELTO can be given to your child with or without food.
- The adult caregiver should give the dose.
- If your child is taking the tablet, the tablet should be taken whole and should not be split in an attempt to provide a lower dose of XARELTO.
- If your child is taking the oral suspension, use the syringes provided in the original carton. The suspension will be prepared by the pharmacy. See the Instructions for Useincluded in the carton on how to properly give a dose of XARELTO oral suspension to your child.
- Do not switch between the XARELTO oral suspension or tablet without first talking to your doctor.
- If your child vomits or spits up:
  - right after or within 30 minutes of taking the oral suspension, give a new full dose.
  - more than 30 minutes after taking the oral suspension, do not give the dose again. Give the next dose at the regularly scheduled time.
  - if vomiting or spitting up persists, contact your child's doctor right away.
- If your child misses a dose:
  - If your child is taking XARELTO 1 time a day, give the dose as soon as you remember on the same day. If this is not possible, skip this dose and give the next dose at the regularly scheduled time.
  - If your child is taking XARELTO 2 times a day, give the missed morning dose as soon as you remember. You may give the missed morning dose together with the evening dose. However, a missed evening dose can only be taken in the same evening.
  - If your child is taking XARELTO 3 times a day, skip the missed dose and give the next dose at the regularly scheduled time.

What are the possible side effects of XARELTO?
XARELTO may cause serious side effects:

- See " What is the most important information I should know about XARELTO?"

The most common side effect of XARELTO in adults was bleeding.
The most common side effects of XARELTO in children include:

- bleeding
- vomiting

- cough
- inflamed stomach and gut

Call your doctor for medical advice about side effects. You may report side effects to FDA at 1 800-FDA-1088.

How should I store XARELTO?

- Store XARELTO tablets and suspension at room temperature between 68 °F to 77 °F (20 °C to 25 °C).
- Store syringes and bottle upright in the original carton for XARELTO suspension.
- Do notfreeze XARELTO suspension.

Keep XARELTO and all medicines out of the reach of children.
Discard XARELTO suspension after "Discard after" date written on the bottle.

General information about the safe and effective use of XARELTO.
Medicines are sometimes prescribed for purposes other than those listed in a Medication Guide. Do not use XARELTO for a condition for which it was not prescribed. Do not give XARELTO to other people, even if they have the same symptoms that you have. It may harm them. You can ask your pharmacist or doctor for information about XARELTO that is written for health professionals.

What are the ingredients in XARELTO?
Active ingredient:rivaroxaban
Inactive ingredients tablets:
croscarmellose sodium, hypromellose, lactose monohydrate, magnesium stearate, microcrystalline cellulose, and sodium lauryl sulfate.
The proprietary film coating mixture for XARELTO 2.5 mg tablets is Opadry®Light Yellow and contains: ferric oxide yellow, hypromellose, polyethylene glycol 3350, and titanium dioxide.
The proprietary film coating mixture for XARELTO 10 mg tablets is Opadry®Pink and contains: ferric oxide red, hypromellose, polyethylene glycol 3350, and titanium dioxide.
The proprietary film coating mixture for XARELTO 15 mg tablets is Opadry®Red and contains: ferric oxide red, hypromellose, polyethylene glycol 3350, and titanium dioxide.
The proprietary film coating mixture for XARELTO 20 mg tablets is Opadry®II Dark Red and contains: ferric oxide red, polyethylene glycol 3350, polyvinyl alcohol (partially hydrolyzed), talc, and titanium dioxide.
Inactive ingredients for oral suspension:
anhydrous citric acid, hypromellose, mannitol, microcrystalline cellulose and carboxymethylcellulose sodium, sodium benzoate, sucralose, sweet and creamy flavor, and xanthan gum.
Manufactured for: Janssen Pharmaceuticals, Inc., Titusville, NJ 08560, USA. Licensed from: Bayer HealthCare AG 51368 Leverkusen, Germany
For patent information: www.janssenpatents.com
© Johnson & Johnson and its affiliates 2011-2021, 2025
Xarelto is a registered trademark of Bayer Aktiengesellschaft.
For more information go to www.XARELTO-US.com or call 1-800-526-7736.

This Medication Guide has been approved by the U.S. Food and Drug Administration

Revised: 06/2025

Instructions for Use XARELTO® (zah-REL-toe) (rivaroxaban) for oral suspension

This Instructions for Use contains information on how to give a dose of XARELTO oral suspension.

Read this Instructions for Use before giving XARELTO and each time you get a refill. There may be new information. This leaflet does not take the place of talking with your doctor about your child's medical condition or treatment.

Important information:

- XARELTO suspension is for oral use only.
- Give XARELTO to your child exactly as prescribed by your doctor. The adult caregiver should give the dose. If you have questions, contact your doctor or pharmacist for more information on giving a dose.
- Only use the oral dosing syringe provided with XARELTO oral suspension.Contact your doctor or pharmacist if the oral dosing syringe is missing, lost or damaged.

Storage information

Store XARELTO oral suspension at room temperature between 68°F to 77°F(20°C to 25°C). Do notfreeze.

Store the bottle upright with the oral dosing syringes in the original carton.

Keep XARELTO and all medicines out of reach of children.

XARELTO Oral Dosing Syringe:

Side 1: Dosing in milliliters (mL)

Side 2: Dosing with color band [The color band is an aid to withdraw the prescribed dose.] (mL)

XARELTO Bottle

Step 1 | Get ready

Check "Discard after" date on the XARELTO bottle.

If "Discard after" date has passed, do notuse and call your doctor or pharmacist.

Wash hands.

Wash your hands well with soap and warm water.

Step 2 | Prepare XARELTO

Shake bottle slowly for 10 seconds before each use.

Do notshake the bottle too fast to avoid foaming.
Foaming may lead to giving the wrong dose.

Check XARELTO oral suspension.

If there are lumps or granules at the bottom of the bottle, shake the bottle slowlyagain for 10 seconds.

Step 3 | Check the prescribed dose

Find your dose line.

You can use either side of the syringe to set your dose.

If using mL side of syringe:

Top of the plunger should line up with the prescribed mL.

If using color side of syringe:

Top of the plunger should line up with the prescribed mL dose line at the bottom of the color band.

Only use the oral dosing syringe provided with XARELTO oral suspension.

If your dose is more than 5 mL.

You will need to use the same syringe more than one time. Repeat Steps 4 and 5 to complete your dose. Ask your pharmacist if you are not sure.

Step 4 | Set prescribed dose

Push plunger all the way in to remove air.

Insert oral dosing syringe into bottle adaptor.

Twist off the cap from the bottle.

Do notremove the bottle adaptor from the bottle.

Insert the syringe tip into the bottle adaptor.

Fill oral dosing syringe.

Turn the bottle upside down, as shown.

Pull the plunger to fill the oral dosing syringe slightly past your prescribed dose lineto help remove any air bubbles.

CAUTION:

Make sure you have enough medicine for a full dose. Do not take a partial dose.

Tap syringe to move air bubbles to the top.

Doing this helps set the correct dose.

Adjust to your prescribed dose.

If using mL side of syringe:Push plunger to align with the prescribed dose line.

If using color side of syringe:Push plunger to align with the prescribed mL dose line at the bottom of the color band.

Remove oral dosing syringe.

Place the bottle on a flat surface.

Remove the oral dosing syringe from the bottle.

Step 5 | Give the dose

Give the dose.

Place the oral dosing syringe gently into the child's mouth with the tip of the syringe pointing toward the cheek and slowly press the plunger.

This allows the child to swallow naturally.

Make sure the child swallows the full dose.

If your child vomits or spits out the medicine repeatedly, contact your child's doctor right away.

If your dose is more than 5 mL, you will need to use the same syringe more than one time. Repeat Steps 4 and 5 to complete your dose.

Step 6 | Rinse and store

Close XARELTO bottle and rinse oral dosing syringe.

Rinse the oral dosing syringe with tap water and let it air dry.

Do notplace the oral dosing syringe in the dishwasher.

Disposing XARELTO bottle and syringe

- Throw the XARELTO bottle away in your household trash.
- Throw away any used oral dosing syringe with the opening of a new XARELTO bottle.
- Do not pour XARELTO suspension down the drain(for example: sink, toilet, shower or tub).
- Do notrecycle the bottle.

Manufactured for:
Janssen Pharmaceuticals, Inc.
Titusville, NJ 08560
Licensed from:
Bayer HealthCare AG
51368 Leverkusen, Germany

For patent information: www.janssenpatents.com

© 2021 Janssen Pharmaceutical Companies

This Instructions for Use has been approved by the U.S. Food and Drug Administration.
Issued: 02/2023

PRINCIPAL DISPLAY PANEL - 2.5 mg Tablet Bottle Label

NDC 50458-577-60

Xarelto®
(rivaroxaban)
Tablets 2.5 mg

Dispense the accompanying
Medication Guide to each patient.

Each tablet contains
2.5 mg of rivaroxaban.

Rx only

60 Tablets

PRINCIPAL DISPLAY PANEL - 10 mg Tablet Bottle Label

NDC 50458-580-30

Xarelto®
(rivaroxaban)
Tablets 10 mg

Dispense the accompanying
Medication Guide to each patient.

Each tablet contains
10 mg of rivaroxaban.

Rx only

30 Tablets

PRINCIPAL DISPLAY PANEL - 15 mg Tablet Bottle Label

NDC 50458-578-30

Xarelto®
(rivaroxaban)
Tablets 15 mg

Dispense the accompanying
Medication Guide to each patient.

Each tablet contains
15 mg of rivaroxaban.

Rx only

30 Tablets

PRINCIPAL DISPLAY PANEL - 20 mg Tablet Bottle Label

NDC 50458-579-30

Xarelto®
(rivaroxaban)
Tablets 20 mg

Dispense the accompanying
Medication Guide to each patient.

Each tablet contains
20 mg of rivaroxaban.

Rx only

30 Tablets

PRINCIPAL DISPLAY PANEL - Kit Carton

Xarelto®
(rivaroxaban) Tablets

NDC 50458-584-51
Rx only

Please see full Prescribing Information, including
BOXED WARNINGS, and Medication Guide inside.

Starter Pack
for treatment of deep vein thrombosis and treatment of pulmonary embolism

Days 1-21
15mg per tablet, twice daily
42 tablets

Days 22-30
20mg per tablet, once daily
9 tablets

First 30-day supply

LIFT HERE TO OPEN

PRINCIPAL DISPLAY PANEL - 1 mg/mL Bottle Carton

NDC 50458-575-01

Xarelto®
(rivaroxaban)
for Oral Suspension

1 mg/mL
(when reconstituted)

Pharmacist:

- Must reconstitute before
  dispensing.
- Counsel caregiver on proper use.

ATTENTION: Dispense the
enclosed Medication Guide
to each patient.

For Oral Use Only

Rx only
Johnson & Johnson